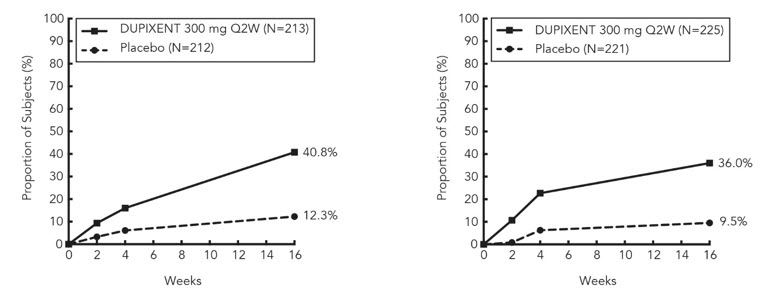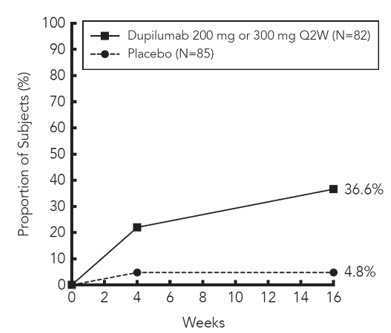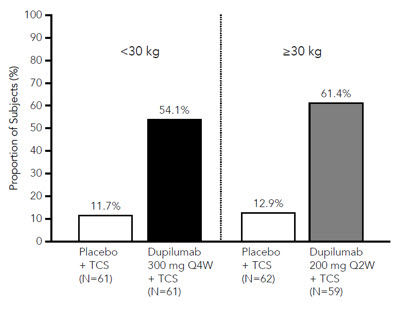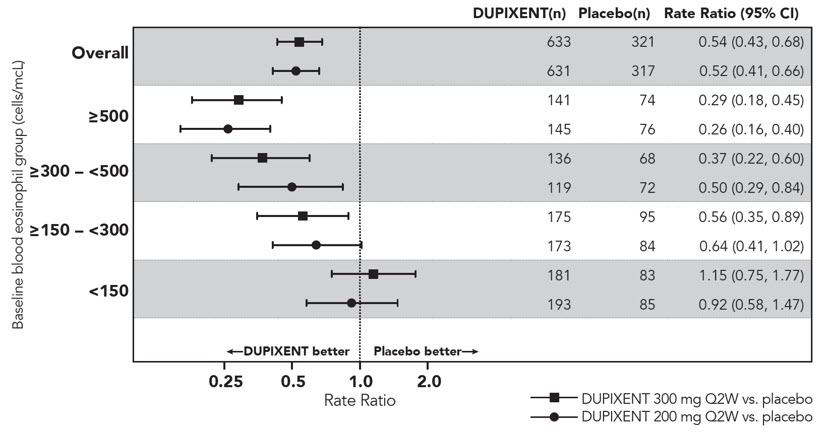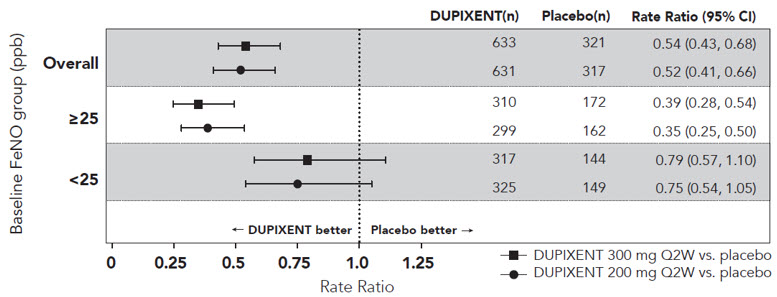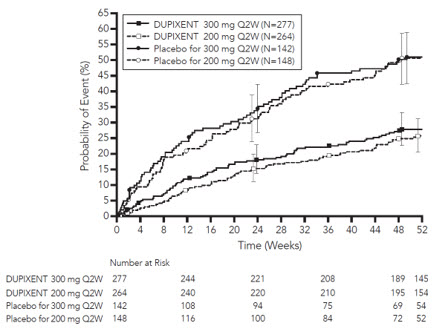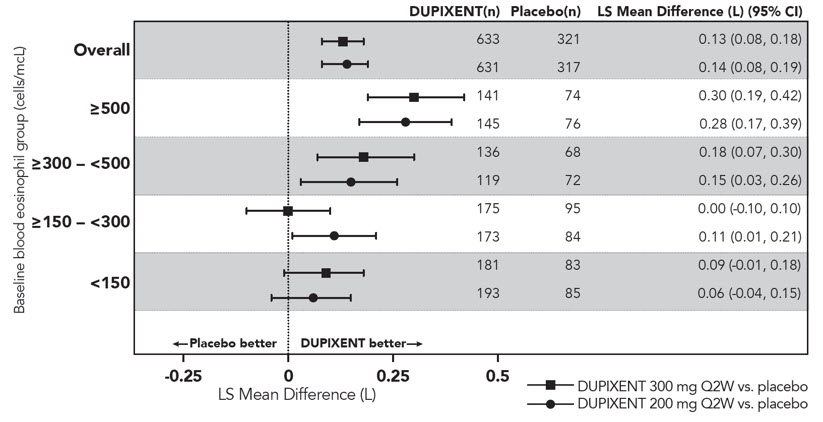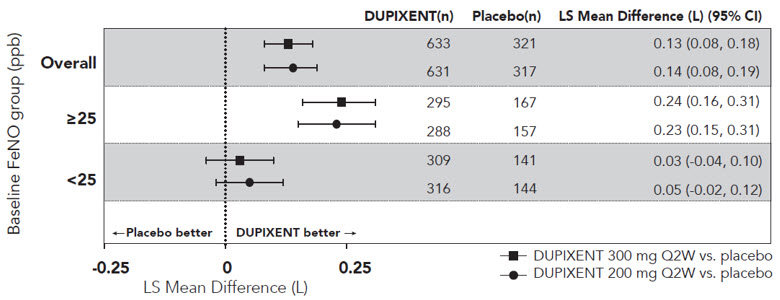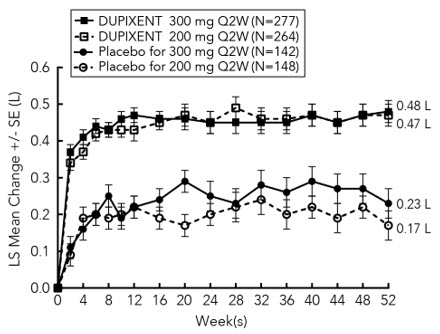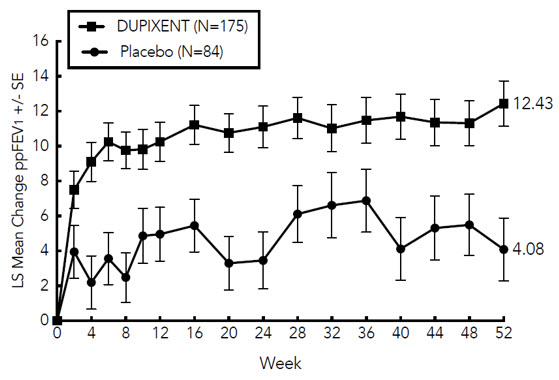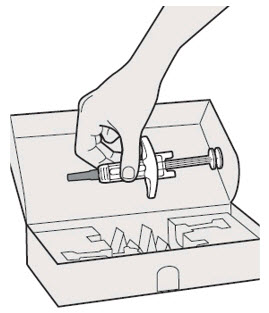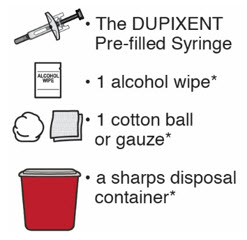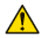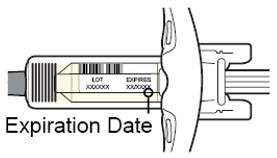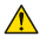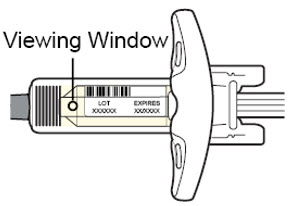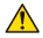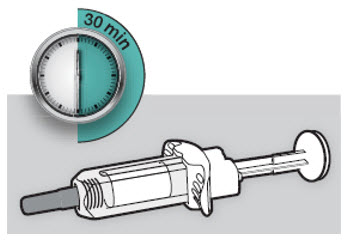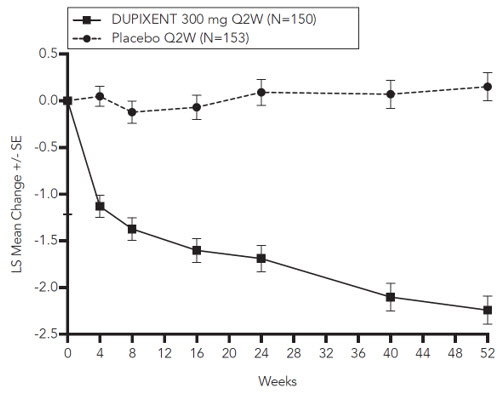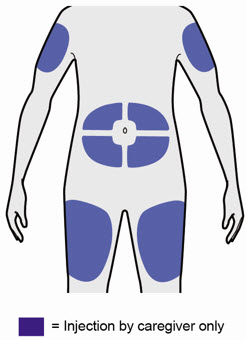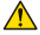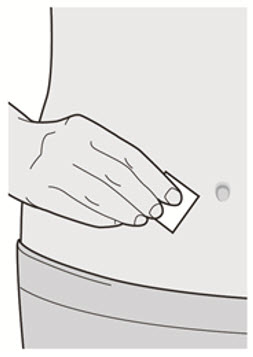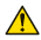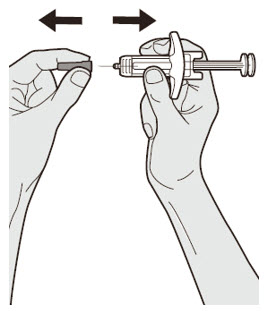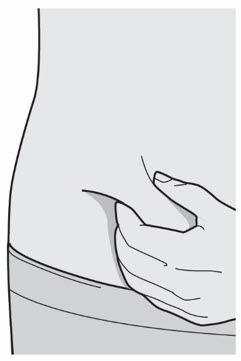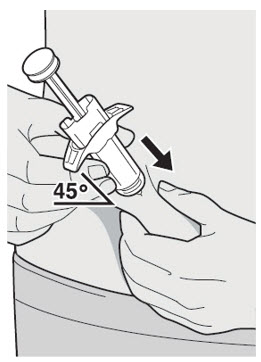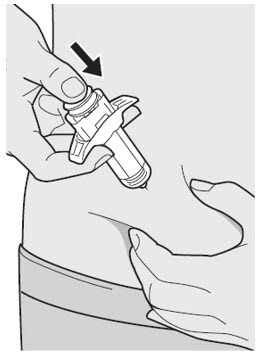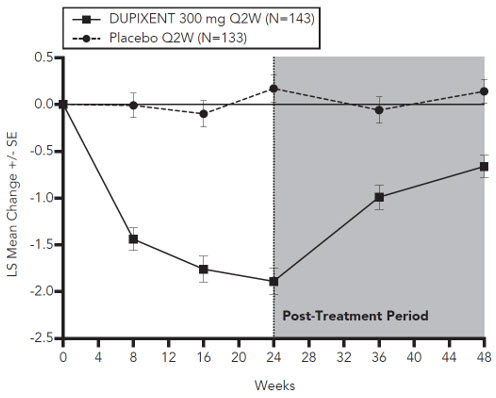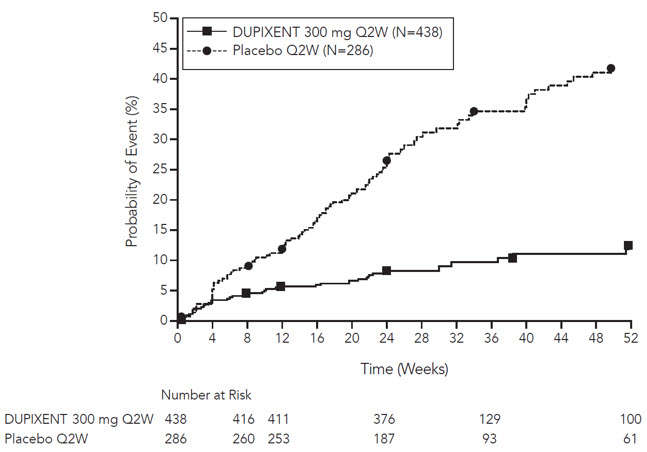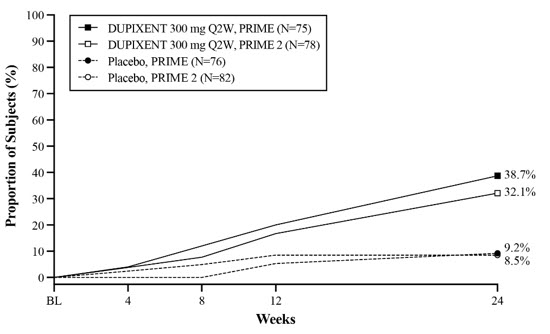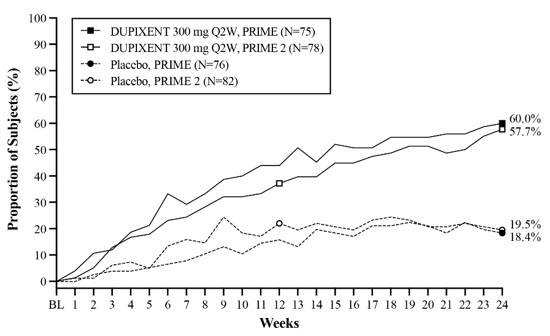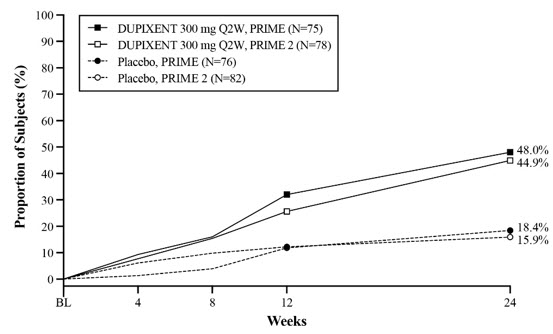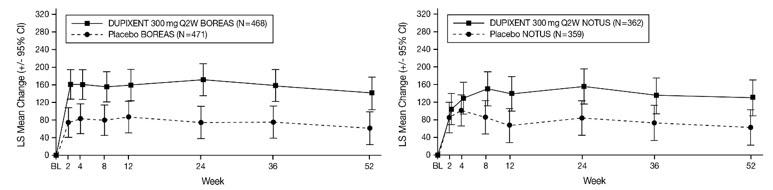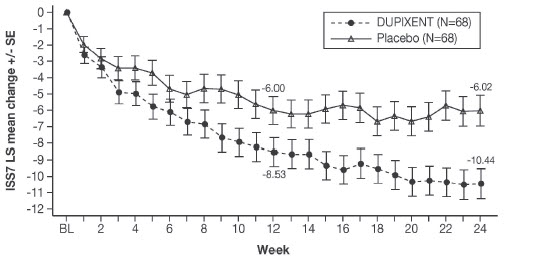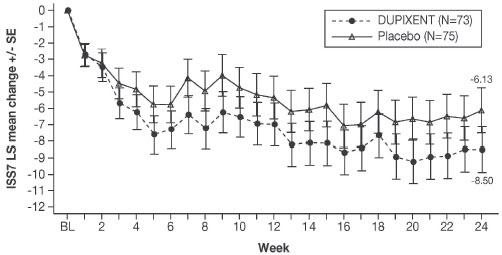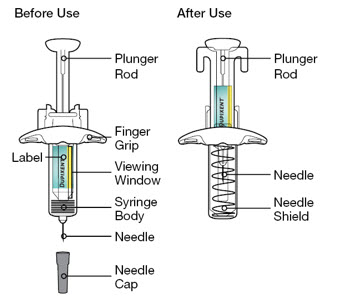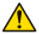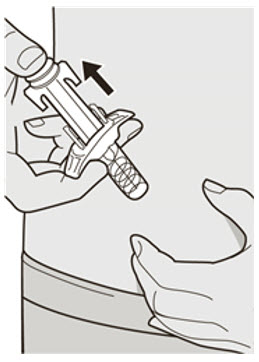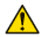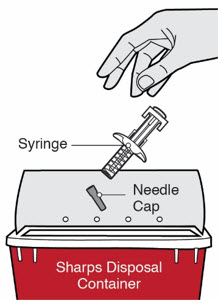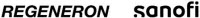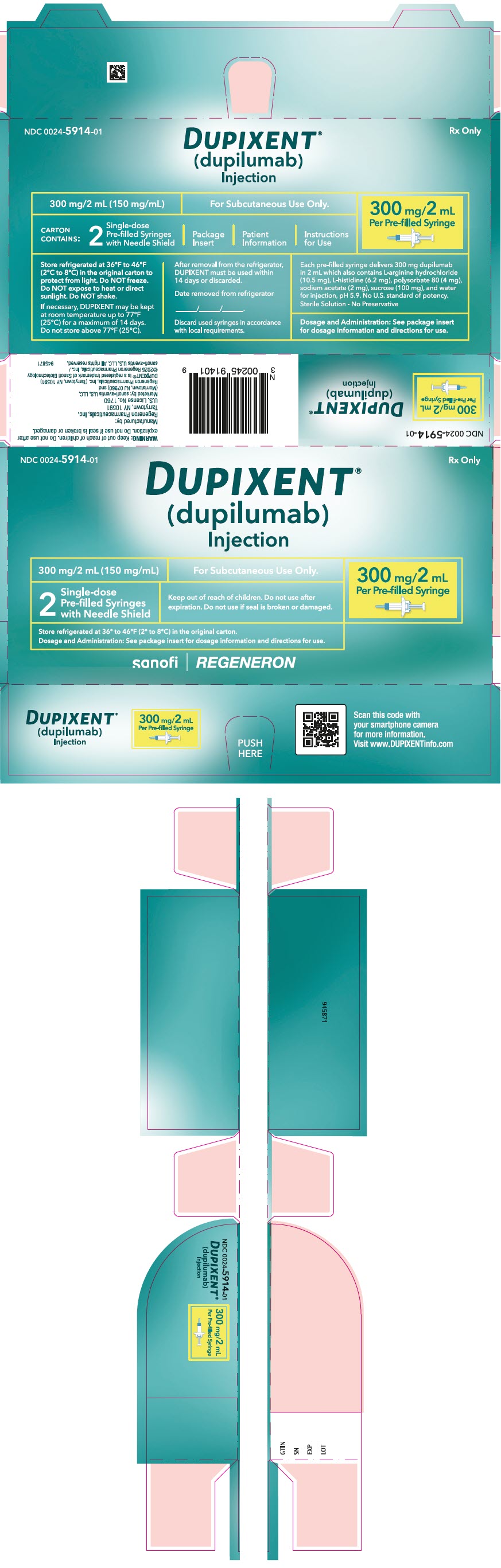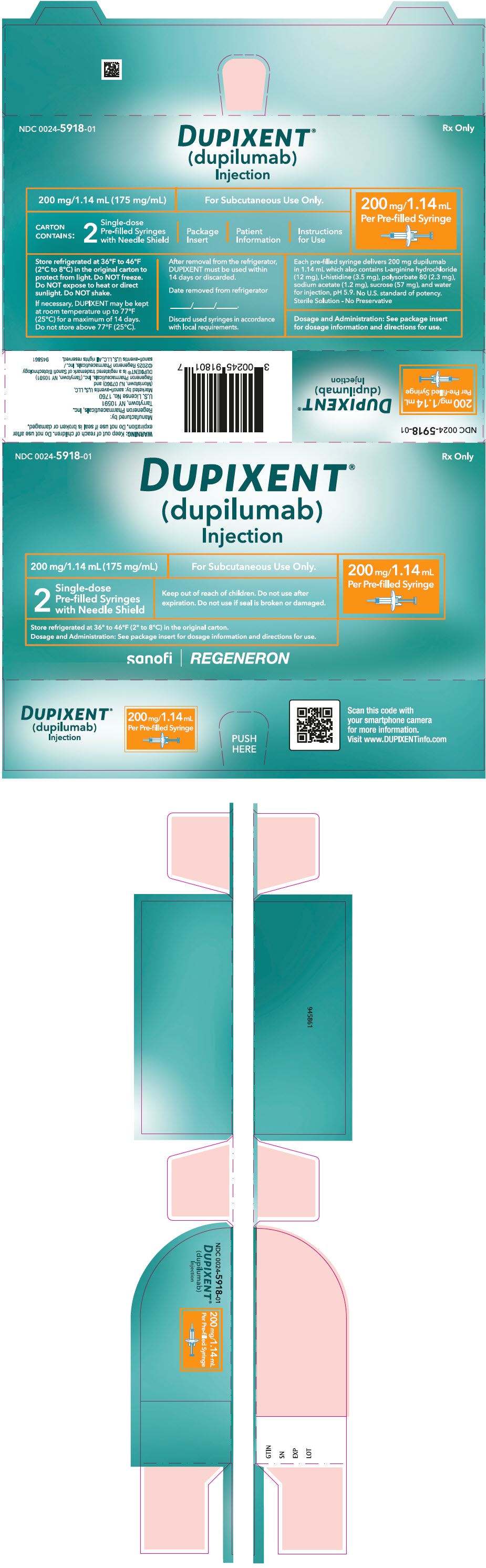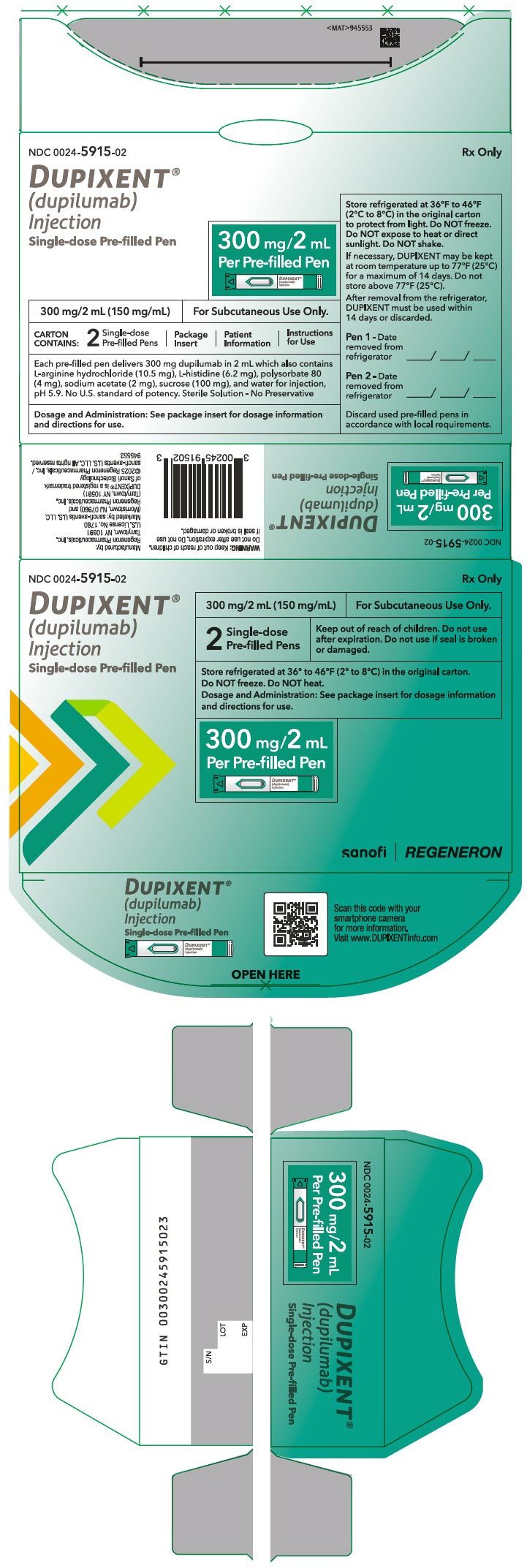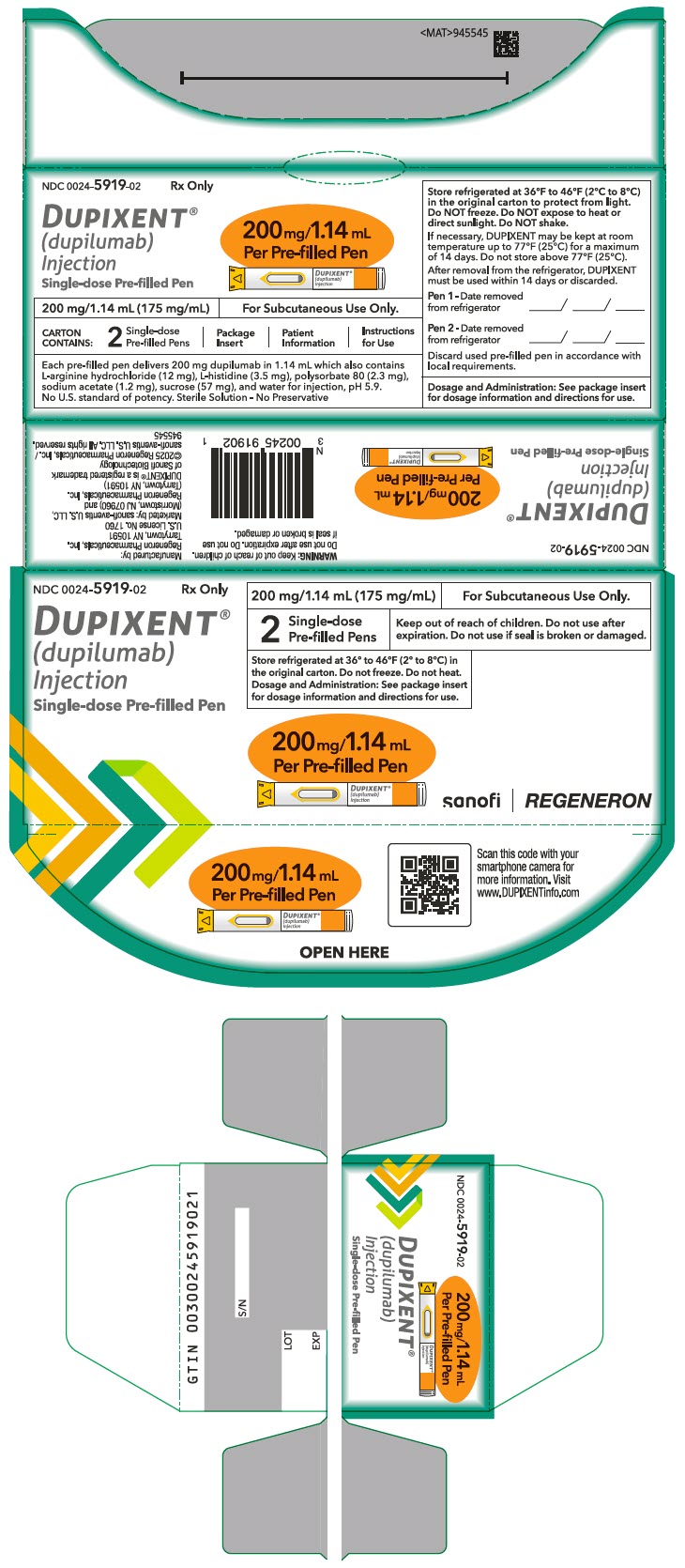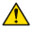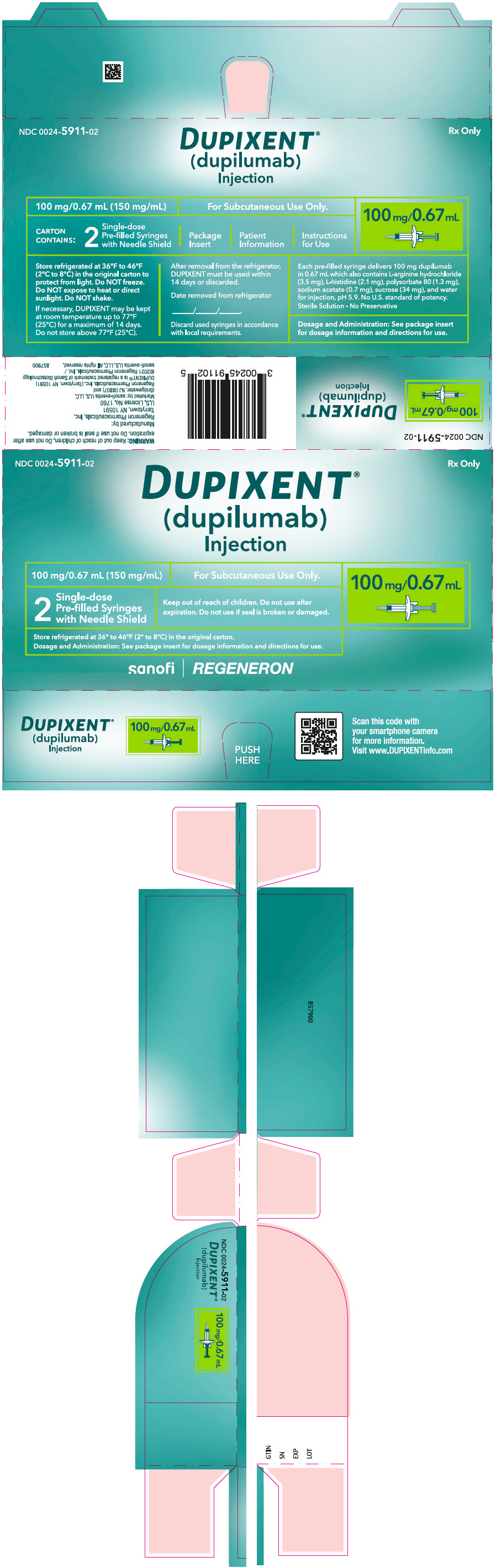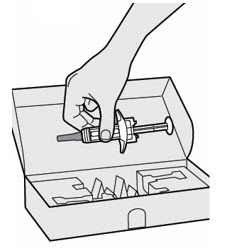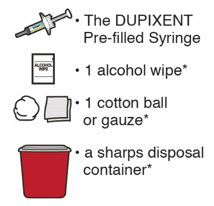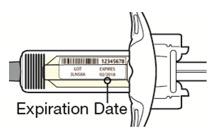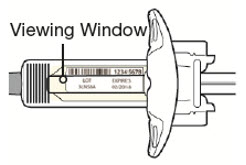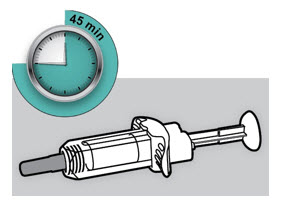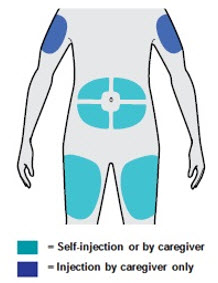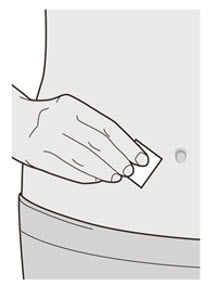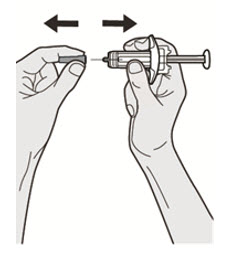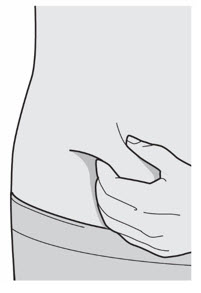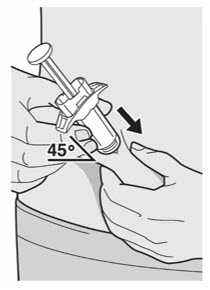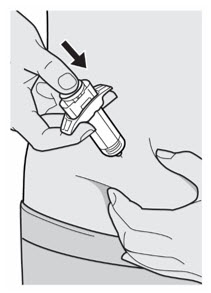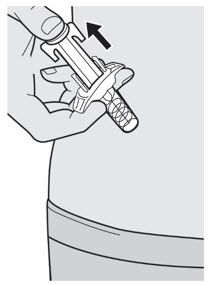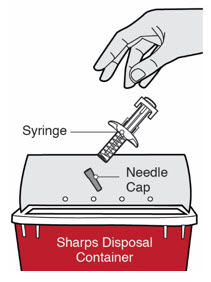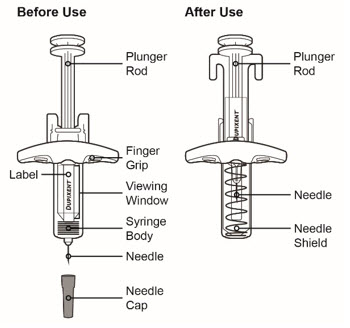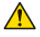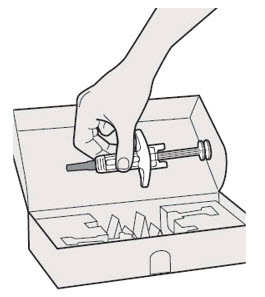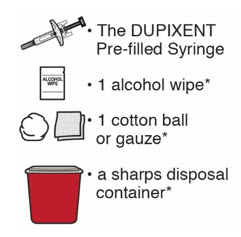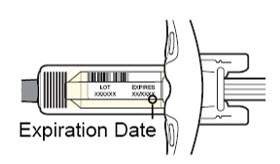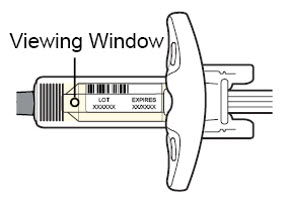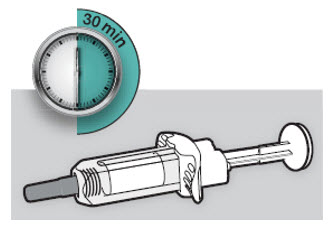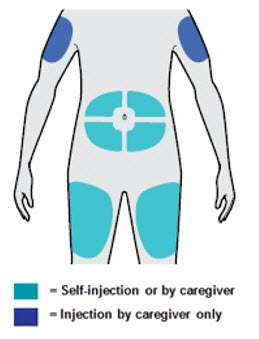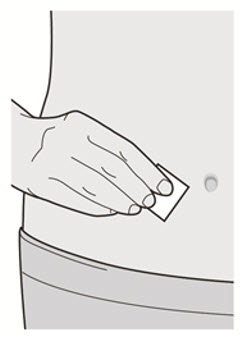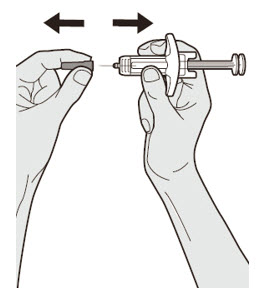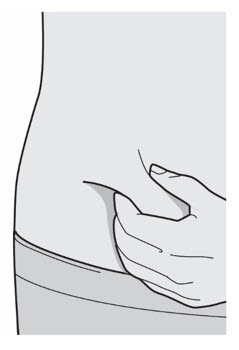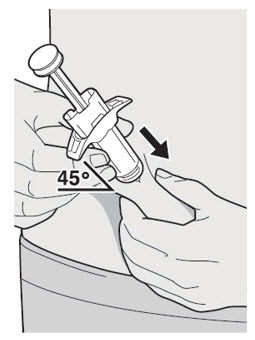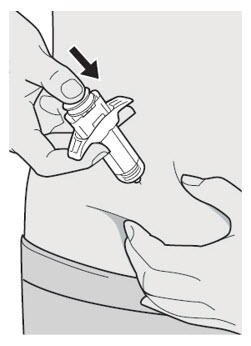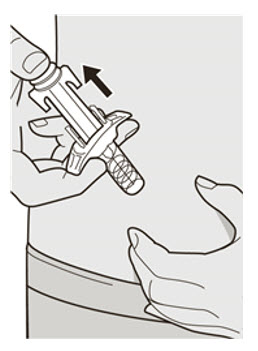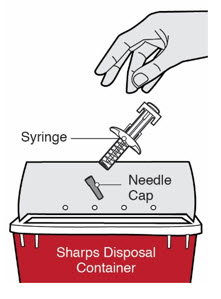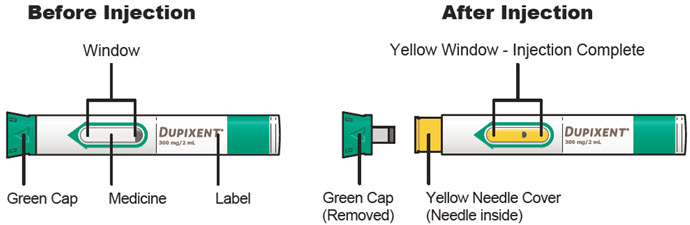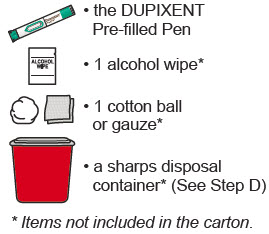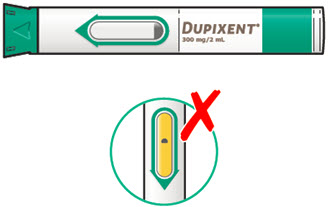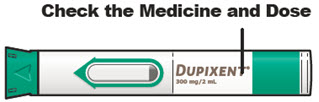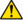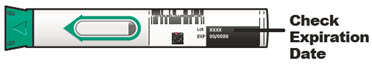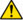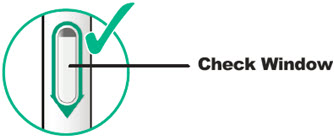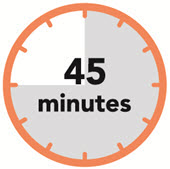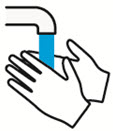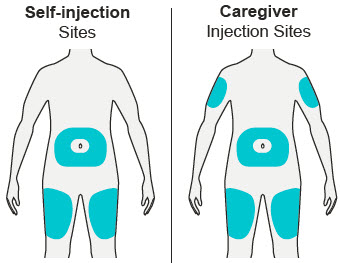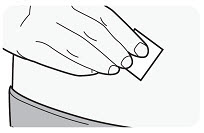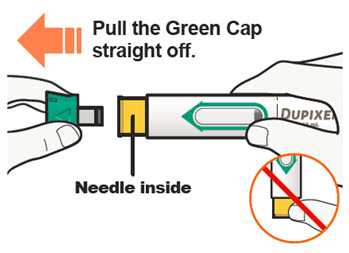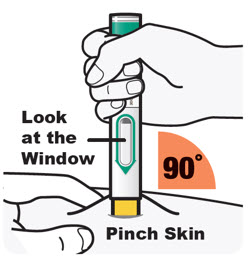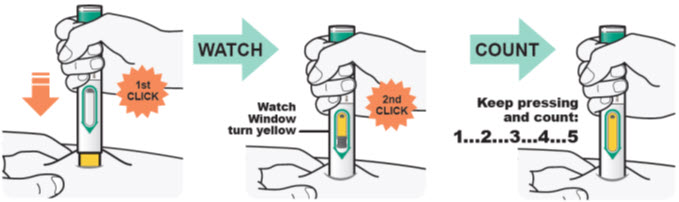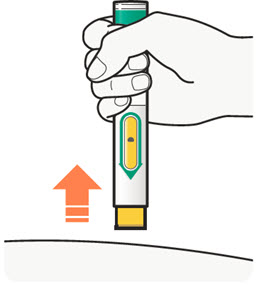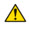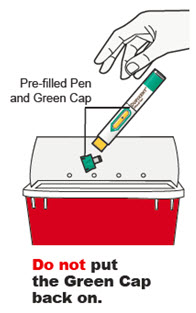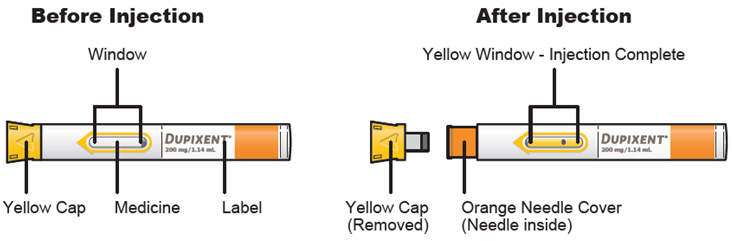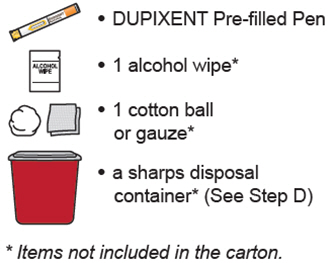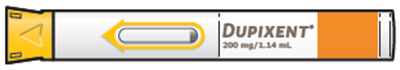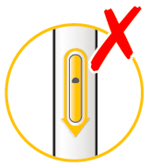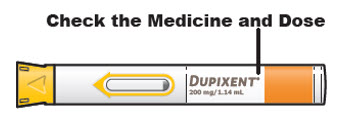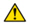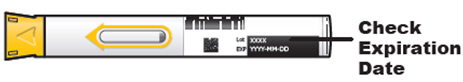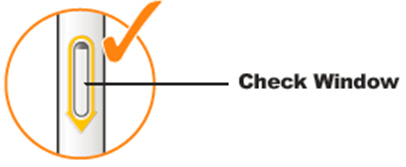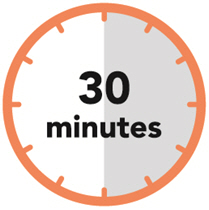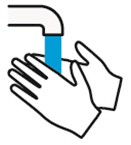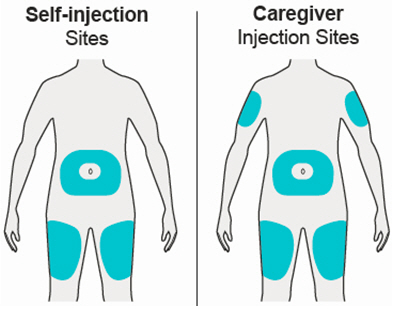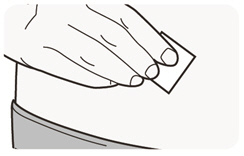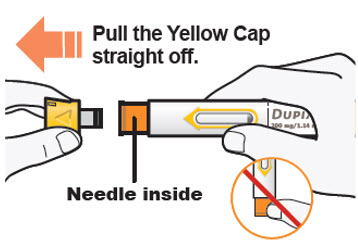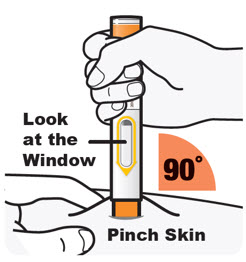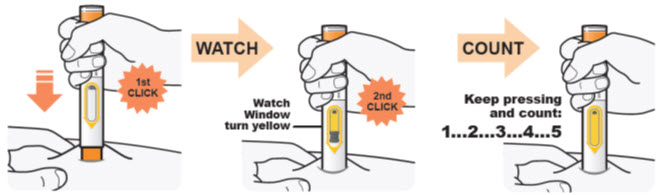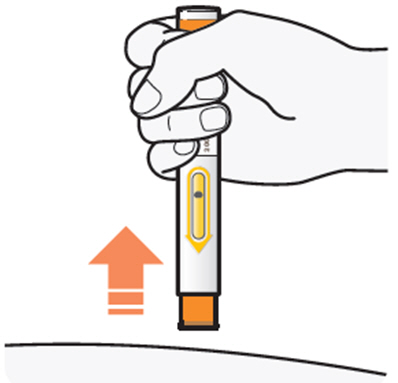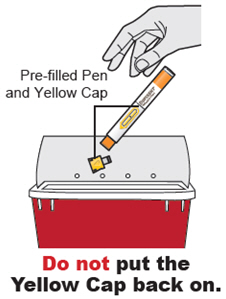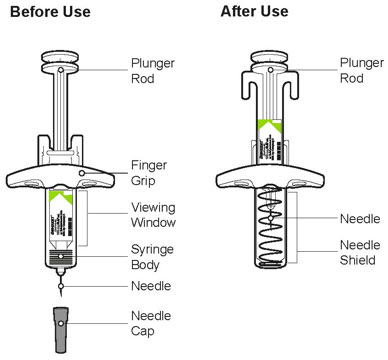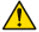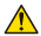 DRUG LABEL: Dupixent
NDC: 0024-5914 | Form: INJECTION, SOLUTION
Manufacturer: sanofi-aventis U.S. LLC
Category: prescription | Type: HUMAN PRESCRIPTION DRUG LABEL
Date: 20250930

ACTIVE INGREDIENTS: Dupilumab 300 mg/2 mL
INACTIVE INGREDIENTS: ARGININE HYDROCHLORIDE; HISTIDINE; polysorbate 80; sodium acetate; sucrose; water

HIGHLIGHTS OF PRESCRIBING INFORMATION

These highlights do not include all the information needed to use DUPIXENT safely and effectively. See full prescribing information for DUPIXENT.
DUPIXENT® (dupilumab) injection, for subcutaneous use
Initial U.S. Approval: 2017

RECENT MAJOR CHANGES

Indications and Usage, Chronic Rhinosinusitis with Nasal Polyps (1.3) | 09/2024
Indications and Usage, Chronic Obstructive Pulmonary Disease (1.6) | 09/2024
Indications and Usage, Chronic Spontaneous Urticaria (1.7) | 04/2025
Indications and Usage, Bullous Pemphigoid (1.8) | 06/2025
Dosage and Administration, Chronic Rhinosinusitis with Nasal Polyps (2.5) | 09/2024
Dosage and Administration, Chronic Obstructive Pulmonary Disease (2.8) | 09/2024
Dosage and Administration, Chronic Spontaneous Urticaria (2.9) | 04/2025
Dosage and Administration, Bullous Pemphigoid (2.10) | 06/2025
Dosage and Administration, Missed Doses (2.11) | 06/2025
Warnings and Precautions, Hypersensitivity (5.1) | 06/2025
Warnings and Precautions, Conjunctivitis and Keratitis (5.2) | 06/2025
Warnings and Precautions (5.2, 5.3, 5.7, 5.8) | 04/2025
Warnings and Precautions (5.2, 5.4) | 09/2024

1 INDICATIONS AND USAGE

DUPIXENT is an interleukin-4 receptor alpha antagonist indicated:

Atopic Dermatitis

for the treatment of adult and pediatric patients aged 6 months and older with moderate-to-severe AD whose disease is not adequately controlled with topical prescription therapies or when those therapies are not advisable. DUPIXENT can be used with or without topical corticosteroids. (1.1)

Asthma

as an add-on maintenance treatment of adult and pediatric patients aged 6 years and older with moderate-to-severe asthma characterized by an eosinophilic phenotype or with oral corticosteroid dependent asthma. (1.2)
Limitations of Use: Not for the relief of acute bronchospasm or status asthmaticus. (1.2)

Chronic Rhinosinusitis with Nasal Polyps

as an add-on maintenance treatment in adult and pediatric patients aged 12 years and older with inadequately controlled chronic rhinosinusitis with nasal polyps (CRSwNP). (1.3)

Eosinophilic Esophagitis

for the treatment of adult and pediatric patients aged 1 year and older, weighing at least 15 kg, with eosinophilic esophagitis (EoE). (1.4)

Prurigo Nodularis

for the treatment of adult patients with prurigo nodularis (PN). (1.5)

Chronic Obstructive Pulmonary Disease

as an add-on maintenance treatment of adult patients with inadequately controlled chronic obstructive pulmonary disease (COPD) and an eosinophilic phenotype. (1.6)
Limitations of Use: Not for the relief of acute bronchospasm. (1.6)

Chronic Spontaneous Urticaria

for the treatment of adult and pediatric patients aged 12 years and older with chronic spontaneous urticaria (CSU) who remain symptomatic despite H1 antihistamine treatment. (1.7)

Limitations of Use: Not indicated for other forms of urticaria. (1.7)

Bullous Pemphigoid

for the treatment of adult patients with bullous pemphigoid (BP). (1.8)

2 DOSAGE AND ADMINISTRATION

DUPIXENT is administered by subcutaneous injection. (2.1)

Atopic Dermatitis
Dosage in Adults (2.3):

Recommended dosage is an initial dose of 600 mg (two 300 mg injections), followed by 300 mg given every 2 weeks (Q2W).

Dosage in Pediatric Patients 6 Months to 5 Years of Age (2.3):

Body Weight | Initial and Subsequent Dosage
5 to less than 15 kg | 200 mg (one 200 mg injection) every 4 weeks (Q4W)
15 to less than 30 kg | 300 mg (one 300 mg injection) every 4 weeks (Q4W)

Dosage in Pediatric Patients 6 Years of Age and Older (2.3):

Body Weight | Initial Loading Dose | Subsequent Dosage [Q2W – every 2 weeks; Q4W – every 4 weeks]
15 to less than 30 kg | 600 mg (two 300 mg injections) | 300 mg Q4W
30 to less than 60 kg | 400 mg (two 200 mg injections) | 200 mg Q2W
60 kg or more | 600 mg (two 300 mg injections) | 300 mg Q2W

Asthma
Dosage in Adult and Pediatric Patients 12 Years and Older (2.4):

Initial Loading Dose | Subsequent Dosage
400 mg (two 200 mg injections) | 200 mg every 2 weeks (Q2W)
Or
600 mg (two 300 mg injections) | 300 mg every 2 weeks (Q2W)
Dosage for patients with oral corticosteroid-dependent asthma or with co-morbid moderate-to-severe atopic dermatitis or adults with co-morbid chronic rhinosinusitis with nasal polyps
600 mg (two 300 mg injections) | 300 mg every 2 weeks (Q2W)

Dosage in Pediatric Patients 6 to 11 Years of Age (2.4):

Body Weight | Initial Dose and Subsequent Dosage
15 to less than 30 kg | 300 mg every 4 weeks (Q4W)
≥30 kg | 200 mg every 2 weeks (Q2W)

For pediatric patients 6 to 11 years old with asthma and co-morbid moderate-to-severe atopic dermatitis, follow the recommended dosage as per Table 2 which includes an initial loading dose. (2.3)

Chronic Rhinosinusitis with Nasal Polyps (2.5):

Recommended dosage for adult and pediatric patients 12 years of age and older is 300 mg given every 2 weeks (Q2W).

Eosinophilic Esophagitis (2.6):

Body Weight | Recommended Dosage in Adult and Pediatric Patients 1 Year and Older, Weighing At Least 15 kg
15 to less than 30 kg | 200 mg every 2 weeks (Q2W)
30 to less than 40 kg | 300 mg every 2 weeks (Q2W)
40 kg or more | 300 mg every week (QW)

Prurigo Nodularis (2.7):

Recommended dosage for adult patients is an initial dose of 600 mg (two 300 mg injections), followed by 300 mg given every 2 weeks (Q2W).

Chronic Obstructive Pulmonary Disease (2.8):

Recommended dosage for adult patients is 300 mg given every 2 weeks (Q2W).

Chronic Spontaneous Urticaria
Dosage in Adults (2.9):

Recommended dosage is an initial dose of 600 mg (two 300 mg injections), followed by 300 mg given every 2 weeks (Q2W).

Dosage in Pediatric Patients 12 to 17 Years of Age (2.9):

Body Weight | Initial Loading Dose | Subsequent Dosage
30 to less than 60 kg | 400 mg (two 200 mg injections) | 200 mg Q2W
60 kg or more | 600 mg (two 300 mg injections) | 300 mg Q2W

Bullous Pemphigoid (2.10):

Recommended dosage for adult patients is an initial dose of 600 mg (two 300 mg injections), followed by 300 mg given every other week (Q2W). Use DUPIXENT in combination with a tapering course of oral corticosteroids.

3 DOSAGE FORMS AND STRENGTHS

Single-Dose Pre-Filled Syringe with Needle Shield (3):

- Injection: 300 mg/2 mL (150 mg/mL)
- Injection: 200 mg/1.14 mL (175 mg/mL)

Single-Dose Pre-Filled Pen (3):

- Injection: 300 mg/2 mL (150 mg/mL)
- Injection: 200 mg/1.14 mL (175 mg/mL)

4 CONTRAINDICATIONS

Known hypersensitivity to dupilumab or any excipients in DUPIXENT. (4)

5 WARNINGS AND PRECAUTIONS

- Hypersensitivity: Hypersensitivity reactions including anaphylaxis, acute generalized exanthematous pustulosis (AGEP), serum sickness, angioedema, urticaria, rash, erythema nodosum, and erythema multiforme have occurred. Discontinue DUPIXENT in the event of a hypersensitivity reaction. (5.1)
- Conjunctivitis and Keratitis: Advise patients to report new onset or worsening eye symptoms to their healthcare provider. Consider ophthalmological examination, as appropriate. (5.2)
- Eosinophilic Conditions: Be alert to vasculitic rash, worsening pulmonary symptoms, cardiac complications, kidney injury and/or neuropathy, especially upon reduction of oral corticosteroids. (5.3)
- Reduction of Corticosteroid Dosage: Do not discontinue systemic, topical, or inhaled corticosteroids abruptly upon initiation of DUPIXENT. Decrease steroids gradually, if appropriate. (5.5)
- Psoriasis: Advise patients to report new-onset psoriasis symptoms to their healthcare provider. If symptoms persist or worsen, consider dermatologic evaluation and/or discontinuation of DUPIXENT. (5.7)
- Arthralgia and Psoriatic Arthritis: Advise patients to report new onset joint symptoms to their healthcare provider. If symptoms persist or worsen, consider rheumatological evaluation and/or discontinuation of DUPIXENT. (5.8)
- Parasitic (Helminth) Infections: Treat pre-existing helminth infections before initiating DUPIXENT. If patients become infected while receiving DUPIXENT and do not respond to anti-helminth treatment, discontinue DUPIXENT until the infection resolves. (5.9)
- Vaccinations: Avoid use of live vaccines. (5.10)

6 ADVERSE REACTIONS

Most common adverse reactions are:

- Atopic Dermatitis (incidence ≥1%): injection site reactions, conjunctivitis, blepharitis, oral herpes, keratitis, eye pruritus, other herpes simplex virus infection, dry eye, and eosinophilia. (6.1)
- Asthma (incidence ≥1%): injection site reactions, oropharyngeal pain, and eosinophilia. (6.1)
- Chronic Rhinosinusitis with Nasal Polyps (incidence ≥1%): injection site reactions, eosinophilia, insomnia, toothache, gastritis, arthralgia, and conjunctivitis. (6.1)
- Eosinophilic Esophagitis (incidence ≥2%): injection site reactions, upper respiratory tract infections, arthralgia, and herpes viral infections. (6.1)
- Prurigo Nodularis (incidence ≥2%): nasopharyngitis, conjunctivitis, herpes infection, dizziness, myalgia, and diarrhea. (6.1)
- Chronic Obstructive Pulmonary Disease (incidence ≥2%): viral infection, headache, nasopharyngitis, back pain, diarrhea, arthralgia, urinary tract infection, local administration reactions, rhinitis, eosinophilia, toothache, and gastritis. (6.1)
- Chronic Spontaneous Urticaria (incidence ≥2%): injection site reactions. (6.1)
- Bullous Pemphigoid (incidence ≥2%): arthralgia, conjunctivitis, vision blurred, herpes viral infections, keratitis. (6.1)

To report SUSPECTED ADVERSE REACTIONS, contact Regeneron at 1-844-387-4936 or FDA at 1-800-FDA-1088 or www.fda.gov/medwatch.

FULL PRESCRIBING INFORMATION

1 INDICATIONS AND USAGE

1.1 Atopic Dermatitis

DUPIXENT is indicated for the treatment of adult and pediatric patients aged 6 months and older with moderate-to-severe atopic dermatitis (AD) whose disease is not adequately controlled with topical prescription therapies or when those therapies are not advisable. DUPIXENT can be used with or without topical corticosteroids.

1.2 Asthma

DUPIXENT is indicated as an add-on maintenance treatment of adult and pediatric patients aged 6 years and older with moderate-to-severe asthma characterized by an eosinophilic phenotype or with oral corticosteroid dependent asthma.

Limitations of Use

DUPIXENT is not indicated for the relief of acute bronchospasm or status asthmaticus.

1.3 Chronic Rhinosinusitis with Nasal Polyps

DUPIXENT is indicated as an add-on maintenance treatment in adult and pediatric patients aged 12 years and older with inadequately controlled chronic rhinosinusitis with nasal polyps (CRSwNP).

1.4 Eosinophilic Esophagitis

DUPIXENT is indicated for the treatment of adult and pediatric patients aged 1 year and older, weighing at least 15 kg, with eosinophilic esophagitis (EoE).

1.5 Prurigo Nodularis

DUPIXENT is indicated for the treatment of adult patients with prurigo nodularis (PN).

1.6 Chronic Obstructive Pulmonary Disease

DUPIXENT is indicated as an add-on maintenance treatment of adult patients with inadequately controlled chronic obstructive pulmonary disease (COPD) and an eosinophilic phenotype.

Limitations of Use

DUPIXENT is not indicated for the relief of acute bronchospasm.

1.7 Chronic Spontaneous Urticaria

DUPIXENT is indicated for the treatment of adult and pediatric patients aged 12 years and older with chronic spontaneous urticaria (CSU) who remain symptomatic despite H1 antihistamine treatment.

Limitations of Use:

DUPIXENT is not indicated for treatment of other forms of urticaria.

1.8 Bullous Pemphigoid

DUPIXENT is indicated for the treatment of adult patients with bullous pemphigoid (BP).

2 DOSAGE AND ADMINISTRATION

2.1 Important Administration Instructions

DUPIXENT is administered by subcutaneous injection.

DUPIXENT is intended for use under the guidance of a healthcare provider. Provide proper training to patients and/or caregivers on the preparation and administration of DUPIXENT prior to use according to the "Instructions for Use".

Use of Pre-filled Pen or Pre-filled Syringe

The DUPIXENT pre-filled pen is for use in adult and pediatric patients aged 2 years and older.

The DUPIXENT pre-filled syringe is for use in adult and pediatric patients aged 6 months and older.

A caregiver or patient 12 years of age and older may inject DUPIXENT using the pre-filled syringe or pre-filled pen. In pediatric patients 12 years of age and older, administer DUPIXENT under the supervision of an adult. In pediatric patients 6 months to less than 12 years of age, administer DUPIXENT by a caregiver.

Administration Instructions

For patients with AD, asthma, PN, CSU, and BP taking an initial 600 mg dose, administer each of the two DUPIXENT 300 mg injections at different injection sites.

For patients with AD, asthma, and CSU taking an initial 400 mg dose, administer each of the two DUPIXENT 200 mg injections at different injection sites.

Administer subcutaneous injection into the thigh or abdomen, except for the 2 inches (5 cm) around the navel. The upper arm can also be used if a caregiver administers the injection.

Rotate the injection site with each injection. DO NOT inject DUPIXENT into skin that is tender, damaged, bruised, or scarred.

The DUPIXENT "Instructions for Use" contains more detailed instructions on the preparation and administration of DUPIXENT [see Instructions for Use].

2.2 Vaccination Prior to Treatment

Consider completing all age-appropriate vaccinations as recommended by current immunization guidelines prior to initiating treatment with DUPIXENT [see Warnings and Precautions (5.10)].

2.3 Recommended Dosage for Atopic Dermatitis

Dosage in Adults

The recommended dosage of DUPIXENT for adult patients is an initial dose of 600 mg (two 300 mg injections), followed by 300 mg given every 2 weeks (Q2W).

Dosage in Pediatric Patients 6 Months to 5 Years of Age

The recommended dosage of DUPIXENT for pediatric patients 6 months to 5 years of age is specified in Table 1.

Table 1: Dosage of DUPIXENT in Pediatric Patients 6 Months to 5 Years of Age with Atopic Dermatitis
Body Weight | Initial [For pediatric patients 6 months to 5 years of age with AD, no initial loading dose is recommended.] and Subsequent Dosage
5 to less than 15 kg | 200 mg (one 200 mg injection) every 4 weeks (Q4W)
15 to less than 30 kg | 300 mg (one 300 mg injection) every 4 weeks (Q4W)

Dosage in Pediatric Patients 6 Years of Age and Older

The recommended dosage of DUPIXENT for pediatric patients 6 years of age and older is specified in Table 2.

Table 2: Dosage of DUPIXENT in Pediatric Patients 6 Years of Age and Older with Atopic Dermatitis
Body Weight | Initial Loading Dose | Subsequent Dosage
15 to less than 30 kg | 600 mg (two 300 mg injections) | 300 mg every 4 weeks (Q4W)
30 to less than 60 kg | 400 mg (two 200 mg injections) | 200 mg every 2 weeks (Q2W)
60 kg or more | 600 mg (two 300 mg injections) | 300 mg every 2 weeks (Q2W)

Concomitant Topical Therapies

DUPIXENT can be used with or without topical corticosteroids. Topical calcineurin inhibitors may be used, but should be reserved for problem areas only, such as the face, neck, intertriginous and genital areas.

2.4 Recommended Dosage for Asthma

Dosage in Adult and Pediatric Patients 12 Years and Older

The recommended dosage of DUPIXENT for adult and pediatric patients 12 years of age and older is specified in Table 3.

Table 3: Dosage of DUPIXENT in Adult and Pediatric Patients 12 Years and Older with Asthma
Initial Loading Dose | Subsequent Dosage
400 mg (two 200 mg injections) | 200 mg every 2 weeks (Q2W)
Or
600 mg (two 300 mg injections) | 300 mg every 2 weeks (Q2W)
Dosage for patients with oral corticosteroid-dependent asthma or with co-morbid moderate-to-severe atopic dermatitis or adults with co-morbid chronic rhinosinusitis with nasal polyps
600 mg (two 300 mg injections) | 300 mg every 2 weeks (Q2W)

Dosage in Pediatric Patients 6 to 11 Years of Age

The recommended dosage of DUPIXENT for pediatric patients 6 to 11 years of age is specified in Table 4.

Table 4: Dosage of DUPIXENT in Pediatric Patients 6 to 11 Years of Age with Asthma
Body Weight | Initial [For pediatric patients 6 to 11 years of age with asthma, no initial loading dose is recommended.] and Subsequent Dosage
15 to less than 30 kg | 300 mg every 4 weeks (Q4W)
≥30 kg | 200 mg every 2 weeks (Q2W)

For pediatric patients 6 to 11 years of age with asthma and co-morbid moderate-to-severe AD, follow the recommended dosage as per Table 2 which includes an initial loading dose [see Dosage and Administration (2.3)].

2.5 Recommended Dosage for Chronic Rhinosinusitis with Nasal Polyps

The recommended dosage of DUPIXENT for adult and pediatric patients 12 years of age and older is 300 mg given every 2 weeks (Q2W).

2.6 Recommended Dosage for Eosinophilic Esophagitis

The recommended dosage of DUPIXENT for adult and pediatric patients 1 year of age and older, weighing at least 15 kg, is specified in Table 5.

Table 5: Dosage of DUPIXENT in Adult and Pediatric Patients 1 Year of Age and Older with Eosinophilic Esophagitis
Body Weight | Recommended Dosage
15 to less than 30 kg | 200 mg every 2 weeks (Q2W)
30 to less than 40 kg | 300 mg every 2 weeks (Q2W)
40 kg or more | 300 mg every week (QW)

2.7 Recommended Dosage for Prurigo Nodularis

The recommended dosage of DUPIXENT for adult patients is an initial dose of 600 mg (two 300 mg injections) followed by 300 mg given every 2 weeks (Q2W).

2.8 Recommended Dosage for Chronic Obstructive Pulmonary Disease

The recommended dosage of DUPIXENT for adult patients is 300 mg given every 2 weeks (Q2W).

2.9 Recommended Dosage for Chronic Spontaneous Urticaria

Dosage in Adults

The recommended dosage of DUPIXENT for adult patients is an initial dose of 600 mg (two 300 mg injections), followed by 300 mg given every 2 weeks (Q2W).

Dosage in Pediatric Patients 12 to 17 Years of Age

The recommended dosage of DUPIXENT for pediatric patients 12 to 17 years of age is specified in Table 6.

Table 6: Dosage of DUPIXENT in Pediatric Patients 12 to 17 Years of Age with CSU
Body Weight | Initial Loading Dose | Subsequent Dosage
30 to less than 60 kg | 400 mg (two 200 mg injections) | 200 mg every 2 weeks (Q2W)
60 kg or more | 600 mg (two 300 mg injections) | 300 mg every 2 weeks (Q2W)

2.10 Recommended Dosage for Bullous Pemphigoid

The recommended dosage of DUPIXENT for adult patients is an initial dose of 600 mg (two 300 mg injections) followed by 300 mg given every other week (Q2W).

Concomitant Oral Corticosteroids:

Use DUPIXENT in combination with a tapering course of oral corticosteroids. Once disease control has occurred, gradually taper corticosteroids after which continue DUPIXENT as monotherapy. In case of relapse, corticosteroids may be added if medically advisable.

2.11 Missed Doses

If a weekly dose is missed, administer the dose as soon as possible, and start a new weekly schedule from the date of the last administered dose.

If an every 2 week dose is missed, administer the injection within 7 days from the missed dose and then resume the patient's original schedule. If the missed dose is not administered within 7 days, administer the dose, starting a new schedule based on this date.

If an every 4 week dose is missed, administer the injection within 7 days from the missed dose and then resume the patient's original schedule. If the missed dose is not administered within 7 days, administer the dose, starting a new schedule based on this date.

2.12 Preparation for Use

Before injection, remove DUPIXENT from the refrigerator and allow DUPIXENT to reach room temperature (45 minutes for the 300 mg/2 mL pre-filled syringe or pre-filled pen, and 30 minutes for the 200 mg/1.14 mL pre-filled syringe or pre-filled pen) without removing the needle cap. After removal from the refrigerator, DUPIXENT must be used within 14 days or discarded.

Inspect DUPIXENT visually for particulate matter and discoloration prior to administration. DUPIXENT is a clear to slightly opalescent, colorless to pale yellow solution. Do not use if the liquid contains visible particulate matter, is discolored or cloudy (other than clear to slightly opalescent, colorless to pale yellow). DUPIXENT does not contain preservatives; therefore, discard any unused product remaining in the pre-filled syringe or pre-filled pen.

3 DOSAGE FORMS AND STRENGTHS

DUPIXENT is a clear to slightly opalescent, colorless to pale yellow solution in a:

Single-dose pre-filled syringe with needle shield as:

- Injection: 300 mg/2 mL (150 mg/mL)
- Injection: 200 mg/1.14 mL (175 mg/mL)

Single-dose pre-filled pen as:

- Injection: 300 mg/2 mL (150 mg/mL)
- Injection: 200 mg/1.14 mL (175 mg/mL)

4 CONTRAINDICATIONS

DUPIXENT is contraindicated in patients who have known hypersensitivity to dupilumab or any excipients of DUPIXENT [see Warnings and Precautions (5.1)].

5 WARNINGS AND PRECAUTIONS

5.1 Hypersensitivity

Hypersensitivity reactions, including anaphylaxis, acute generalized exanthematous pustulosis (AGEP), serum sickness or serum sickness-like reactions, angioedema, generalized urticaria, rash, erythema nodosum and erythema multiforme have been reported. A case of AGEP was reported in an adult subject who participated in the bullous pemphigoid development program. If a clinically significant hypersensitivity reaction occurs, institute appropriate therapy and discontinue DUPIXENT [see Adverse Reactions (6.1, 6.2) and Clinical Pharmacology (12.6)].

5.2 Conjunctivitis and Keratitis

Conjunctivitis and keratitis adverse reactions have been reported in clinical trials [see Adverse Reactions (6.1)].

Conjunctivitis and keratitis occurred more frequently in AD subjects who received DUPIXENT compared to those who received placebo. Conjunctivitis was the most frequently reported eye disorder. Most subjects with conjunctivitis or keratitis recovered or were recovering during the treatment period.

Among subjects with asthma, the frequencies of conjunctivitis and keratitis were similar between DUPIXENT and placebo.

In adult subjects with CRSwNP, the frequency of conjunctivitis was 2% in the DUPIXENT group compared to 1% in the placebo group in the 24-week safety pool; these subjects recovered. There were no cases of keratitis reported in the CRSwNP development program.

Among subjects with EoE, there were no reports of conjunctivitis and keratitis in the DUPIXENT group in placebo-controlled trials.

In subjects with PN, the frequency of conjunctivitis was 4% in the DUPIXENT group compared to 1% in the placebo group; these subjects recovered or were recovering during the treatment period. There were no cases of keratitis reported in the PN development program.

Among subjects with COPD, the frequency of conjunctivitis and keratitis was 1.4% and 0.1% in the DUPIXENT group and 1% and 0% in the placebo group, respectively.

In subjects with CSU, the frequency of conjunctivitis was similar between DUPIXENT and placebo. There were no cases of keratitis reported in the CSU development program.

Among subjects with BP, the frequency of conjunctivitis and keratitis was 7.5% and 3.8% in the DUPIXENT group and 0% and 0% in the placebo group, respectively.

Conjunctivitis and keratitis adverse events have also been reported with DUPIXENT in postmarketing settings, predominantly in AD patients. Some patients reported visual disturbances (e.g., blurred vision) associated with conjunctivitis or keratitis.

Advise patients or their caregivers to report new onset or worsening eye symptoms to their healthcare provider. Consider ophthalmological examination for patients who develop conjunctivitis that does not resolve following standard treatment or signs and symptoms suggestive of keratitis, as appropriate.

5.3 Eosinophilic Conditions

Patients being treated for asthma may present with clinical features of eosinophilic pneumonia or eosinophilic granulomatosis with polyangiitis (EGPA). These events may be associated with the reduction of oral corticosteroid therapy. Healthcare providers should be alert to vasculitic rash, worsening pulmonary symptoms, cardiac complications, kidney injury, and/or neuropathy presenting in their patients with eosinophilia. Cases of eosinophilic pneumonia were reported in adults who participated in the asthma development program. Cases of EGPA have been reported with DUPIXENT in adults who participated in the asthma development program as well as in adults with co-morbid asthma in the CRSwNP development program. Advise patients to report signs of eosinophilic pneumonia and EGPA to their healthcare provider. Consider withholding DUPIXENT if eosinophilic pneumonia or EGPA are suspected.

5.4 Acute Symptoms of Asthma or Chronic Obstructive Pulmonary Disease or Acute Deteriorating Disease

DUPIXENT should not be used to treat acute symptoms or acute exacerbations of asthma or COPD. Do not use DUPIXENT to treat acute bronchospasm or status asthmaticus. Patients should seek medical advice if their asthma or COPD remains uncontrolled or worsens after initiation of treatment with DUPIXENT.

5.5 Risk Associated with Abrupt Reduction of Corticosteroid Dosage

Do not discontinue systemic, topical, or inhaled corticosteroids abruptly upon initiation of therapy with DUPIXENT. Reductions in corticosteroid dose, if appropriate, should be gradual and performed under the direct supervision of a healthcare provider. Reduction in corticosteroid dose may be associated with systemic withdrawal symptoms and/or unmask conditions previously suppressed by systemic corticosteroid therapy.

5.6 Patients with Co-morbid Asthma

Advise patients with co-morbid asthma not to adjust or stop their asthma treatments without consultation with their physicians.

5.7 Psoriasis

Cases of new-onset psoriasis have been reported with the use of DUPIXENT for the treatment of atopic dermatitis and asthma, including in patients without a family history of psoriasis. In postmarketing reports, onset of psoriasis varied from weeks to months after the first dose of DUPIXENT and resulted in partial or complete resolution of psoriasis with discontinuation of dupilumab, with or without use of supplemental treatment for psoriasis (topical or systemic). Those who continued on dupilumab received supplemental treatment for psoriasis to improve associated symptoms. Advise patients to report new-onset psoriasis symptoms to their healthcare provider. If symptoms persist or worsen, consider dermatologic evaluation and/or discontinuation of DUPIXENT.

5.8 Arthralgia and Psoriatic Arthritis

Arthralgia has been reported with the use of DUPIXENT with some patients reporting gait disturbances or decreased mobility associated with joint symptoms; some cases resulted in hospitalization [see Adverse Reactions (6.1)]. In postmarketing reports, onset of arthralgia was variable, ranging from days to months after the first dose of DUPIXENT.

Cases of new-onset psoriatic arthritis requiring systemic treatment have been reported with the use of DUPIXENT.

Some patients' symptoms resolved while continuing treatment with DUPIXENT, and other patients recovered or were recovering following discontinuation of DUPIXENT.

Advise patients to report new onset or worsening joint symptoms to their healthcare provider. If symptoms persist or worsen, consider rheumatological evaluation and/or discontinuation of DUPIXENT.

5.9 Parasitic (Helminth) Infections

Patients with known helminth infections were excluded from participation in clinical studies. It is unknown if DUPIXENT will influence the immune response against helminth infections.

Treat patients with pre-existing helminth infections before initiating therapy with DUPIXENT. If patients become infected while receiving treatment with DUPIXENT and do not respond to anti-helminth treatment, discontinue treatment with DUPIXENT until the infection resolves. Adverse reactions of helminth infections (5 cases of enterobiasis and 1 case of ascariasis) were reported in pediatric subjects 6 to 11 years old who participated in the pediatric asthma development program [see Adverse Reactions (6.1)].

5.10 Vaccinations

Consider completing all age-appropriate vaccinations as recommended by current immunization guidelines prior to initiating treatment with DUPIXENT. Avoid use of live vaccines during treatment with DUPIXENT. It is unknown if administration of live vaccines during DUPIXENT treatment will impact the safety or effectiveness of these vaccines. Limited data are available regarding coadministration of DUPIXENT with non-live vaccines [see Clinical Pharmacology (12.2)].

6 ADVERSE REACTIONS

The following clinically significant adverse reactions are described elsewhere in the labeling:

- Hypersensitivity [see Warnings and Precautions (5.1)]
- Conjunctivitis and Keratitis [see Warnings and Precautions (5.2)]
- Psoriasis [see Warnings and Precautions (5.7)]
- Arthralgia and Psoriatic Arthritis [see Warnings and Precautions (5.8)]
- Parasitic (Helminth) Infections [see Warnings and Precautions (5.9)]

6.1 Clinical Trials Experience

Because clinical trials are conducted under widely varying conditions, adverse reaction rates observed in the clinical trials of a drug cannot be directly compared to rates in the clinical trials of another drug and may not reflect the rates observed in practice.

Atopic Dermatitis

Adults with Atopic Dermatitis

Three randomized, double-blind, placebo-controlled, multicenter trials (SOLO 1, SOLO 2, and CHRONOS) and one dose-ranging trial (AD-1021) evaluated the safety of DUPIXENT in subjects with moderate-to-severe AD [see Clinical Studies (14)]. In terms of co-morbid conditions, 48% of the subjects had asthma, 49% had allergic rhinitis, 37% had food allergy, and 27% had allergic conjunctivitis. In these 4 trials, 1472 subjects were treated with subcutaneous injections of DUPIXENT, with or without concomitant topical corticosteroids (TCS).

A total of 739 subjects were treated with DUPIXENT for at least 1 year in the development program for moderate-to-severe AD.

SOLO 1, SOLO 2, and AD-1021 compared the safety of DUPIXENT monotherapy to placebo through Week 16. CHRONOS compared the safety of DUPIXENT + TCS to placebo + TCS through Week 52.

AD-1225 is a multicenter, open-label extension (OLE) trial which assessed the long-term safety of repeat doses of DUPIXENT through 260 weeks of treatment in adults with moderate-to-severe AD who had previously participated in controlled trials of DUPIXENT or had been screened for SOLO 1 or SOLO 2. The safety data in AD-1225 reflect exposure to DUPIXENT 200 mg QW, 300 mg QW and 300 mg Q2W in 2677 subjects, including 2254 exposed for at least 52 weeks, 1224 exposed for at least 100 weeks, 561 exposed for at least 148 weeks and 179 exposed for at least 260 weeks.

Weeks 0 to 16 (SOLO 1, SOLO 2, CHRONOS, and AD-1021)

In DUPIXENT monotherapy trials (SOLO 1, SOLO 2, and AD-1021) through Week 16, the proportion of subjects who discontinued treatment because of adverse events was 1.9% in both the DUPIXENT 300 mg Q2W and placebo groups. Table 7 summarizes the adverse reactions that occurred at a rate of at least 1% in the DUPIXENT 300 mg Q2W monotherapy groups, and in the DUPIXENT + TCS group, all at a higher rate than in their respective comparator groups during the first 16 weeks of treatment.

Table 7: Adverse Reactions Occurring in ≥1% of the DUPIXENT Monotherapy Group or the DUPIXENT + TCS Group in the Atopic Dermatitis Trials through Week 16
Adverse Reaction | DUPIXENT Monotherapy [Pooled analysis of SOLO 1, SOLO 2, and AD-1021.] |  | DUPIXENT + TCS [Analysis of CHRONOS where subjects were on background TCS therapy.]
Adverse Reaction | DUPIXENT 300 mg Q2W [DUPIXENT 600 mg at Week 0, followed by 300 mg every 2 weeks.] | Placebo | DUPIXENT 300 mg Q2W + TCS | Placebo + TCS
Adverse Reaction | N=529 n (%) | N=517 n (%) | N=110 n (%) | N=315 n (%)
Injection site reaction | 51 (10) | 28 (5) | 11 (10) | 18 (6)
Conjunctivitis [Conjunctivitis cluster includes conjunctivitis, allergic conjunctivitis, bacterial conjunctivitis, viral conjunctivitis, giant papillary conjunctivitis, eye irritation, and eye inflammation.] | 51 (10) | 12 (2) | 10 (9) | 15 (5)
Blepharitis | 2 (<1) | 1 (<1) | 5 (5) | 2 (1)
Oral herpes | 20 (4) | 8 (2) | 3 (3) | 5 (2)
Keratitis [Keratitis cluster includes keratitis, ulcerative keratitis, allergic keratitis, atopic keratoconjunctivitis, and ophthalmic herpes simplex.] | 1 (<1) | 0 | 4 (4) | 0
Eye pruritus | 3 (1) | 1 (<1) | 2 (2) | 2 (1)
Other herpes simplex virus infection [Other herpes simplex virus infection cluster includes herpes simplex, genital herpes, herpes simplex otitis externa, and herpes virus infection, but excludes eczema herpeticum.] | 10 (2) | 6 (1) | 1 (1) | 1 (<1)
Dry eye | 1 (<1) | 0 | 2 (2) | 1 (<1)

Safety through Week 52 (CHRONOS)

In the DUPIXENT with concomitant TCS trial (CHRONOS) through Week 52, the proportion of subjects who discontinued treatment because of adverse events was 1.8% in DUPIXENT 300 mg Q2W + TCS group and 7.6% in the placebo + TCS group. Two subjects discontinued DUPIXENT because of adverse reactions: atopic dermatitis (1 subject) and exfoliative dermatitis (1 subject).

The safety profile of DUPIXENT + TCS through Week 52 was generally consistent with the safety profile observed at Week 16.

Safety through 260 Weeks (AD-1225)

The long-term safety profile observed in this trial through 260 weeks was generally consistent with the safety profile of DUPIXENT observed in controlled studies.

Pediatric Subjects 12 Years of Age and Older with Atopic Dermatitis

The safety of DUPIXENT was assessed in a trial of 250 pediatric subjects 12 years of age and older with moderate-to-severe AD (AD-1526). The safety profile of DUPIXENT in these subjects through Week 16 was similar to the safety profile seen in adults with AD.

The long-term safety of DUPIXENT was assessed in an open-label extension study in pediatric subjects 12 years of age and older with moderate-to-severe AD (AD-1434). The safety profile of DUPIXENT in subjects followed through Week 52 was similar to the safety profile observed at Week 16 in AD-1526. The long-term safety profile of DUPIXENT observed in pediatric subjects 12 years of age and older was consistent with that seen in adults with AD.

Pediatric Subjects 6 to 11 Years of Age with Atopic Dermatitis

The safety of DUPIXENT with concomitant TCS was assessed in a trial of 367 pediatric subjects 6 to 11 years of age with severe AD (AD-1652). The safety profile of DUPIXENT + TCS in these subjects through Week 16 was similar to the safety profile from trials in adult and pediatric subjects 12 years of age and older with AD.

The long-term safety of DUPIXENT ± TCS was assessed in an open-label extension study of 368 pediatric subjects 6 to 11 years of age with AD (AD-1434). Among subjects who entered this study, 110 (30%) had moderate and 72 (20%) had severe AD at the time of enrollment in AD-1434. The safety profile of DUPIXENT ± TCS in subjects followed through Week 52 was similar to the safety profile observed through Week 16 in AD-1652. The long-term safety profile of DUPIXENT ± TCS observed in pediatric subjects 6 to 11 years of age was consistent with that seen in adult and pediatric subjects 12 years of age and older with AD.

Pediatric Subjects 6 Months to 5 Years of Age with Atopic Dermatitis

The safety of DUPIXENT with concomitant TCS was assessed in a trial of 161 pediatric subjects 6 months to 5 years of age with moderate-to-severe AD (AD-1539). The safety profile of DUPIXENT + TCS in these subjects through Week 16 was similar to the safety profile from trials in adults and pediatric subjects 6 years of age and older with AD.

The long-term safety of DUPIXENT ± TCS was assessed in an open-label extension study of 180 pediatric subjects 6 months to 5 years of age with AD (AD-1434). The majority of subjects were treated with DUPIXENT 300 mg every 4 weeks. The safety profile of DUPIXENT ± TCS in subjects followed through Week 52 was similar to the safety profile observed through Week 16 in AD-1539. The long-term safety profile of DUPIXENT ± TCS observed in pediatric subjects 6 months to 5 years of age was consistent with that seen in adults and pediatric subjects 6 years of age and older with AD. In addition, hand-foot-and-mouth disease was reported in 9 (5%) pediatric subjects and skin papilloma was reported in 4 (2%) pediatric subjects treated with DUPIXENT ± TCS. These cases did not lead to study drug discontinuation.

Atopic Dermatitis with Hand and/or Foot Involvement

The safety of DUPIXENT was assessed in a 16-week, multicenter, randomized, double-blind, parallel-group, placebo-controlled trial (Liberty-AD-HAFT) in 133 adult and pediatric subjects 12 to 17 years of age with atopic dermatitis with moderate-to-severe hand and/or foot involvement [see Clinical Studies (14)]. In this trial 67 subjects received DUPIXENT, and 66 subjects received placebo. DUPIXENT-treated subjects received the recommended dosage based on their age and body weight [see Dosage and Administration (2.3)]. The safety profile of DUPIXENT in these subjects through Week 16 was consistent with the safety profile from studies in adult and pediatric subjects 6 months of age and older with moderate-to-severe AD.

Asthma

Adults and Pediatric Subjects 12 Years of Age and Older with Asthma

A total of 2888 adult and pediatric subjects 12 to 17 years of age with moderate-to-severe asthma (AS) were evaluated in 3 randomized, placebo-controlled, multicenter trials of 24 to 52 weeks duration (DRI12544, QUEST, and VENTURE). Of these, 2678 had a history of 1 or more severe exacerbations in the year prior to enrollment despite regular use of medium to high-dose inhaled corticosteroids plus an additional controller(s) (DRI12544 and QUEST). A total of 210 subjects with oral corticosteroid-dependent asthma receiving high-dose inhaled corticosteroids plus up to two additional controllers were enrolled (VENTURE). The safety population (DRI12544 and QUEST) was 12-87 years of age, of which 63% were female, and 82% were White. DUPIXENT 200 mg or 300 mg was administered subcutaneously Q2W, following an initial dose of 400 mg or 600 mg, respectively.

In DRI12544 and QUEST, the proportion of subjects who discontinued treatment due to adverse events was 4% of the placebo group, 3% of the DUPIXENT 200 mg Q2W group, and 6% of the DUPIXENT 300 mg Q2W group.

Table 8 summarizes the adverse reactions that occurred at a rate of at least 1% in subjects treated with DUPIXENT and at a higher rate than in their respective comparator groups in DRI12544 and QUEST.

Table 8: Adverse Reactions Occurring in ≥1% of Adult and Pediatric Subjects 12 Years of Age and Older with Asthma in the DUPIXENT Groups in DRI12544 and QUEST and Greater than Placebo (6 Month Safety Pool)
Adverse Reaction | DRI12544 and QUEST
Adverse Reaction | DUPIXENT 200 mg Q2W | DUPIXENT 300 mg Q2W | Placebo
Adverse Reaction | N=779 n (%) | N=788 n (%) | N=792 n (%)
Injection site reactions [Injection site reactions cluster includes erythema, edema, pruritus, pain, and inflammation.] | 111 (14%) | 144 (18%) | 50 (6%)
Oropharyngeal pain | 13 (2%) | 19 (2%) | 7 (1%)
Eosinophilia [Eosinophilia = blood eosinophils ≥3,000 cells/mcL or deemed by the investigator to be an adverse event. None met the criteria for serious eosinophilic conditions [see Warnings and Precautions (5.3)].] | 17 (2%) | 16 (2%) | 2 (<1%)

Injection site reactions were most common with the loading (initial) dose.

The safety profile of DUPIXENT through Week 52 was generally consistent with the safety profile observed at Week 24.

Pediatric Subjects 6 to 11 Years of Age with Asthma

The safety of DUPIXENT was assessed in 405 pediatric subjects 6 to 11 years of age with moderate-to-severe asthma (VOYAGE). The safety profile of DUPIXENT in these subjects through Week 52 was similar to the safety profile from studies in adult and pediatric subjects 12 years of age and older with moderate-to-severe asthma with the addition of helminth infections. Helminth infections were reported in 2.2% (6 subjects) in the DUPIXENT group and 0.7% (1 subject) in the placebo group. The majority of cases were enterobiasis, reported in 1.8% (5 subjects) in the DUPIXENT group and none in the placebo group. There was one case of ascariasis in the DUPIXENT group. All helminth infection cases were mild to moderate and subjects recovered with anti-helminth treatment without DUPIXENT treatment discontinuation.

Chronic Rhinosinusitis with Nasal Polyps

A total of 722 adult subjects with chronic rhinosinusitis with nasal polyps (CRSwNP) were evaluated in 2 randomized, placebo-controlled, multicenter trials of 24 to 52 weeks duration (SINUS-24 and SINUS-52). The safety pool consisted of data from the first 24 weeks of treatment from both studies.

In the safety pool, the proportion of adult subjects who discontinued treatment due to adverse events was 5% of the placebo group and 2% of the DUPIXENT 300 mg Q2W group.

Table 9 summarizes the adverse reactions that occurred at a rate of at least 1% in adult subjects treated with DUPIXENT and at a higher rate than in their respective comparator group in SINUS-24 and SINUS-52.

Table 9: Adverse Reactions Occurring in ≥1% of Adult Subjects with CRSwNP in the DUPIXENT Group in SINUS-24 and SINUS-52 and Greater than Placebo (24-Week Safety Pool)
Adverse Reaction | SINUS-24 and SINUS-52
Adverse Reaction | DUPIXENT 300 mg Q2W | Placebo
Adverse Reaction | N=440 n (%) | N=282 n (%)
Injection site reactions [Injection site reactions cluster includes injection site reaction, pain, bruising and swelling.] | 28 (6%) | 12 (4%)
Conjunctivitis [Conjunctivitis cluster includes conjunctivitis, allergic conjunctivitis, bacterial conjunctivitis, viral conjunctivitis, giant papillary conjunctivitis, eye irritation, and eye inflammation.] | 7 (2%) | 2 (1%)
Arthralgia | 14 (3%) | 5 (2%)
Gastritis | 7 (2%) | 2 (1%)
Insomnia | 6 (1%) | 0 (<1%)
Eosinophilia | 5 (1%) | 1 (<1%)
Toothache | 5 (1%) | 1 (<1%)

The safety profile of DUPIXENT through Week 52 was generally consistent with the safety profile observed at Week 24.

Eosinophilic Esophagitis

Adults and Pediatric Subjects 12 Years of Age and Older with EoE

A total of 239 adult and pediatric subjects 12 years of age and older, weighing at least 40 kg, with EoE were evaluated in a randomized, double-blind, parallel-group, multicenter, placebo-controlled trial, including two 24-week treatment periods (Study EoE-1 Parts A and B) and received either DUPIXENT 300 mg QW or placebo [see Clinical Studies (14.4)].

The proportion of subjects who discontinued treatment due to adverse events was 2% of the placebo group and 2% of the DUPIXENT 300 mg QW group.

Table 10 summarizes the adverse reactions that occurred at a rate of at least 2% in subjects treated with DUPIXENT and at a higher rate than in their respective comparator group in Parts A and B.

Table 10: Adverse Reactions Occurring in ≥2% of Adult and Pediatric Subjects 12 Years of Age and Older with EoE Treated with DUPIXENT in a Placebo-Controlled Trial (Study EoE-1 Parts A and B; 24-Week Safety Pool)
 | Study EoE-1 Parts A and B
Adverse Reaction | DUPIXENT 300 mg QW N=122 n (%) | Placebo N=117 n (%)
Injection site reactions [Injection site reactions are composed of several terms including, but not limited to, injection site swelling, pain, and bruising.] | 46 (38%) | 39 (33%)
Upper respiratory tract infections [Upper respiratory tract infections are composed of several terms including, but not limited to, COVID-19, sinusitis, and upper respiratory tract infection.] | 22 (18%) | 12 (10%)
Arthralgia | 3 (2%) | 1 (1%)
Herpes viral infections [Herpes viral infections are composed of oral herpes and herpes simplex.] | 3 (2%) | 1 (1%)

The safety profile of DUPIXENT in 72 pediatric subjects 12 to 17 years of age, weighing at least 40 kg, and adults in Parts A and B was similar.

Pediatric Subjects 1 to 11 Years of Age, Weighing at least 15 kg, with EoE

A total of 61 pediatric subjects 1 to 11 years of age, weighing at least 15 kg, with EoE were evaluated in a randomized, blinded, parallel-group, multicenter trial, including an initial 16-week placebo-controlled treatment period (Study EoE-2 Part A) and a 36-week extended active treatment period (Study EoE-2 Part B). Subjects in Part A received a weight-based dosing regimen of DUPIXENT or placebo [see Clinical Studies (14.4)]. All subjects in Part B completed Part A and received active treatment with weight-based dosing regimens of DUPIXENT in Part B (N=47).

The safety profile of DUPIXENT through Week 16 of Study EoE-2 Part A was generally similar to the safety profile in adult and pediatric subjects 12 years of age and older with EoE. In Part B, a helminth infection was reported in one DUPIXENT-treated subject.

Prurigo Nodularis

A total of 309 adult subjects with prurigo nodularis (PN) were evaluated in two 24-week randomized, double-blind, placebo-controlled, multicenter trials (PRIME and PRIME2) [see Clinical Studies (14.5)]. The safety pool included data from the 24-week treatment and 12-week follow-up periods from both trials.

The proportion of subjects who discontinued treatment due to adverse events was 3% of the placebo group and 0% of the DUPIXENT 300 mg Q2W group.

Subjects with co-morbid conditions included 43% of subjects with a history of atopy (defined as having a medical history of AD, allergic rhinitis/rhino conjunctivitis, asthma, or food allergy), 8% of subjects with a history of hypothyroidism and 9% of subjects with a history of diabetes mellitus type 2.

Table 11 summarizes the adverse reactions that occurred at a rate of at least 2% in subjects treated with DUPIXENT and at a higher rate than in their respective comparator group in PRIME and PRIME2.

Table 11: Adverse Reactions Occurring in ≥2% of Adult Subjects with PN in the DUPIXENT Group in PRIME and PRIME2 and Greater than Placebo
Adverse Reaction | PRIME and PRIME2
Adverse Reaction | DUPIXENT 300 mg Q2W | Placebo
Adverse Reaction | N=152 n (%) | N=157 n (%)
Nasopharyngitis [Nasopharyngitis includes pharyngitis] | 8 (5%) | 3 (2%)
Conjunctivitis [Conjunctivitis includes conjunctivitis and allergic conjunctivitis.] | 6 (4%) | 2 (1%)
Herpes Infection [Herpes infection includes oral herpes, genital herpes simplex, herpes zoster and ophthalmic herpes zoster] | 5 (3%) | 0%
Dizziness [Dizziness includes dizziness postural, vertigo and vertigo positional] | 5 (3%) | 2 (1%)
Myalgia [Myalgia includes musculoskeletal pain and musculoskeletal chest pain] | 5 (3%) | 2 (1%)
Diarrhea | 4 (3%) | 1 (1%)

Chronic Obstructive Pulmonary Disease

A total of 1874 adult subjects with inadequately controlled chronic obstructive pulmonary disease (COPD) and an eosinophilic phenotype were evaluated in two randomized, double-blind, multicenter, parallel-group, placebo-controlled trials with a 52-week treatment period (BOREAS and NOTUS) [see Clinical Studies (14.6)]. Of those randomized, 1872 subjects received at least one dose of DUPIXENT 300 mg or placebo subcutaneously every 2 weeks (Q2W). The safety of DUPIXENT was assessed in the pooled safety population from BOREAS and NOTUS, which consisted of 938 adult subjects treated with DUPIXENT. Of the subjects treated with DUPIXENT, 98% utilized inhaled triple therapy at baseline (comprising of an inhaled corticosteroid, long-acting beta-agonist, and long-acting muscarinic antagonist), and 97% had chronic bronchitis.

Table 12 summarizes the adverse reactions that occurred in at least 2% of subjects treated with DUPIXENT and at a higher rate than placebo in BOREAS and NOTUS trials.

Table 12: Adverse Reactions That Occurred in ≥2% of Adult Subjects with COPD Treated with DUPIXENT in BOREAS and NOTUS Trials (Pooled Safety Population) and Greater than Placebo
Adverse Reaction | BOREAS and NOTUS
Adverse Reaction | DUPIXENT 300 mg Q2W | Placebo
Adverse Reaction | N=938 n (%) | N=934 n (%)
Viral Infection [Consists of multiple similar terms.] | 133 (14.2) | 115 (12.3)
Headache | 73 (7.8) | 62 (6.6)
Nasopharyngitis | 73 (7.8) | 69 (7.4)
Back Pain | 42 (4.5) | 29 (3.1)
Diarrhea | 35 (3.7) | 30 (3.2)
Arthralgia | 29 (3.1) | 25 (2.7)
Urinary Tract Infection | 28 (3.0) | 18 (1.9)
Local Administration Reaction | 26 (2.8) | 6 (0.6)
Injection Site Reaction | 11 (1.2) | 2 (0.2)
Rhinitis | 24 (2.6) | 17 (1.8)
Eosinophilia [Eosinophilia was defined as blood eosinophils ≥3,000 cells/mcL or deemed by the investigator to be an adverse event. None met the criteria for serious eosinophilic conditions.] | 22 (2.3) | 7 (0.7)
Toothache | 20 (2.1) | 11 (1.2)
Gastritis | 19 (2) | 7 (0.7)

Less Common Adverse Reaction in Subjects with COPD: Cholecystitis

In adult subjects with COPD, cholecystitis was reported in 6 subjects (0.6%) in the DUPIXENT group compared to 1 subject (0.1%) in the placebo group. Among these subjects, serious cholecystitis was reported in 4 (0.4%) of the DUPIXENT group compared with 0% of the placebo group.

Chronic Spontaneous Urticaria

The pooled safety data below reflects the safety of DUPIXENT in adult and pediatric subjects 12 years of age and older with chronic spontaneous urticaria (CSU) who remain symptomatic despite H1 antihistamine treatment. A total of 392 adult and pediatric subjects 12 years of age and older with CSU were evaluated for safety in three randomized, double-blind, parallel-group, multicenter, placebo-controlled, studies, Study A, B, and C, conducted under a master protocol (CUPID) for 36 weeks [see Clinical Studies (14.7)]. The pooled safety population received an initial dose of DUPIXENT 600 mg or 400 mg, followed by DUPIXENT 300 mg or 200 mg, respectively, or matching placebo, administered subcutaneously every 2 weeks (Q2W) [see Dosage and Administration (2.9)].

Table 13 summarizes the adverse reactions that occurred in at least 2% in subjects treated with DUPIXENT and at a higher rate than placebo in CUPID Study A, B and C (pooled safety population).

Table 13: Adverse Reactions That Occurred in ≥2% of Adult and Pediatric Subjects 12 Years of Age and Older with CSU Treated with DUPIXENT in CUPID Study A, B, and C (Pooled Safety Population) and Greater than Placebo
Adverse Reaction | CUPID Study A, B, and C
Adverse Reaction | DUPIXENT 200 mg Q2W or 300 mg Q2W | Placebo
Adverse Reaction | N=195 n (%) | N=197 n (%)
Injection site reactions [Injection site reactions cluster includes injection site dermatitis, injection site erythema, injection site hematoma, injection site induration, injection site pain, injection site pruritus, injection site reaction, injection site swelling] | 20 (10.3) | 16 (8.1)

Bullous Pemphigoid

The safety of DUPIXENT was evaluated in a 52-week, randomized, double-blind, parallel-group, multicenter, placebo-controlled trial (ADEPT) in a total of 106 adult subjects with moderate-to-severe bullous pemphigoid (BP) [see Clinical Studies (14.8)]. Of the 106 randomized subjects, all received at least one dose of DUPIXENT or placebo with a course of oral corticosteroids (OCS) with a prespecified taper. At the time of analysis, 87 subjects had completed Week 36 and 65 subjects had completed Week 52.

Table 14 summarizes the adverse reactions that occurred in at least 2% of subjects treated with DUPIXENT and at a higher rate than placebo in the ADEPT trial.

Table 14: Adverse Reactions Occurring in ≥2% of Adult Subjects with BP Treated with DUPIXENT in ADEPT and Greater than Placebo [In combination with a tapering course of oral corticosteroids]
Adverse Reaction | ADEPT
Adverse Reaction | DUPIXENT 300 mg Q2W + OCS | Placebo + OCS
Adverse Reaction | N=53 n (%) | N=53 n (%)
Arthralgia | 5 (9%) | 3 (6%)
Conjunctivitis | 4 (8%) | 0%
Vision blurred | 4 (8%) | 0%
Herpes viral infections [Herpes viral infections include herpes simplex and herpes zoster] | 3 (6%) | 0%
Keratitis | 2 (4%) | 0%

A case of AGEP was reported in 1 subject with BP treated with DUPIXENT compared with 0 subjects in the placebo group.

Specific Adverse Reactions for AD, Asthma, CRSwNP, EoE, PN, COPD, CSU and BP

Conjunctivitis and Keratitis

In adult subjects with AD, conjunctivitis was reported in 10% (34 per 100 patient-years) in the 300 mg Q2W dose group and in 2% of the placebo group (8 per 100 patient-years) during the 16-week treatment period of the monotherapy trials (SOLO 1, SOLO 2, and AD-1021). During the 52-week treatment period of concomitant therapy AD trial (CHRONOS), conjunctivitis was reported in 16% of the DUPIXENT 300 mg Q2W + TCS group (20 per 100 patient-years) and in 9% of the placebo + TCS group (10 per 100 patient-years). During the long-term OLE trial with data through 260 weeks (AD-1225), conjunctivitis was reported in 21% of the DUPIXENT group (12 per 100 patient-years).

In DUPIXENT AD monotherapy trials (SOLO 1, SOLO 2, and AD-1021) through Week 16, keratitis was reported in <1% of the DUPIXENT group (1 per 100 patient-years) and in 0% of the placebo group (0 per 100 patient-years). In the 52-week DUPIXENT + topical corticosteroids (TCS) AD trial (CHRONOS), keratitis was reported in 4% of the DUPIXENT + TCS group (4 per 100 patient-years) and in 2% of the placebo + TCS group (2 per 100 patient-years). Conjunctivitis and keratitis occurred more frequently in AD subjects who received DUPIXENT. Conjunctivitis was the most frequently reported eye disorder. During the long-term OLE trial with data through 260 weeks (AD-1225), keratitis was reported in 3% of the DUPIXENT group (1 per 100 patient-years). Most subjects with conjunctivitis or keratitis recovered or were recovering during the treatment period.

Among subjects with asthma, the frequency of conjunctivitis and keratitis was similar between DUPIXENT and placebo.

In adult subjects with CRSwNP, the frequency of conjunctivitis was 2% in the DUPIXENT group compared to 1% in the placebo group in the 24-week safety pool; these subjects recovered.

In the 52-week CRSwNP study (SINUS-52), the frequency of conjunctivitis was 3% in the DUPIXENT adult subjects and 1% in the placebo subjects; all of these subjects recovered. There were no cases of keratitis reported in the CRSwNP development program.

Among subjects with EoE, there were no reports of conjunctivitis and keratitis in the DUPIXENT group in placebo-controlled trials. In the 36-week active treatment extension period of Study EoE-2 Part B, conjunctivitis was reported in 4% of DUPIXENT-treated pediatric subjects with EoE.

Among subjects with PN, the frequency of conjunctivitis was 4% in the DUPIXENT group compared to 1% in the placebo group; all of these subjects recovered or were recovering during the treatment period. There were no cases of keratitis reported in the PN development program.

Among subjects with COPD, the frequency of conjunctivitis and keratitis was 1.4% and 0.1% in the DUPIXENT group and 1% and 0% in the placebo group, respectively.

Among subjects with CSU in the pooled safety population, the frequency of conjunctivitis was similar between DUPIXENT and placebo. There were no cases of keratitis reported in the CSU development program.

Among subjects with BP, the frequency of conjunctivitis and keratitis was 8% and 4% in the DUPIXENT group and 0% and 0% in the placebo group, respectively.

Eczema Herpeticum and Herpes Zoster

The rate of eczema herpeticum was similar in the placebo and DUPIXENT groups in the AD trials. The rates remained stable through 260 weeks in the long-term OLE trial (AD-1225).

Herpes zoster was reported in <1% of the DUPIXENT groups (1 per 100 patient-years) and in <1% of the placebo group (1 per 100 patient-years) in the 16-week AD monotherapy trials. In the 52-week DUPIXENT + TCS AD trial, herpes zoster was reported in 1% of the DUPIXENT + TCS group (1 per 100 patient-years) and 2% of the placebo + TCS group (2 per 100 patient-years). During the long-term OLE trial with data through 260 weeks (AD-1225), 2.0% of DUPIXENT-treated subjects reported herpes zoster (0.94 per 100 patient-years of follow up). Among asthma subjects the frequency of herpes zoster was similar between DUPIXENT and placebo. Among subjects with CRSwNP or EoE there were no reported cases of herpes zoster or eczema herpeticum.

Among subjects with PN, herpes zoster and ophthalmic herpes zoster were each reported in <1% of the DUPIXENT group (1 per 100 patient-years) and 0% of the placebo group.

Among subjects with COPD, herpes zoster was reported in 0.9% of the DUPIXENT group and 0.2% of the placebo group. Ophthalmic herpes zoster was reported in 0.1% of the DUPIXENT group and 0.2% of the placebo group.

Among subjects with CSU in the pooled safety population, herpes zoster was reported in <1% of the DUPIXENT and placebo groups (1 per 100 patient-years). There were no cases of eczema herpeticum reported in the CSU development program.

Among subjects with BP, herpes zoster was reported in 4% of the DUPIXENT group and 0% of the placebo group.

Hypersensitivity Reactions

Hypersensitivity reactions were reported in <1% of DUPIXENT-treated subjects. These included anaphylaxis, AGEP, serum sickness or serum sickness-like reactions, generalized urticaria, rash, erythema nodosum, and erythema multiforme [see Contraindications (4), and Clinical Pharmacology (12.6)].

Eosinophils

DUPIXENT-treated subjects with AD, asthma, CRSwNP, and COPD had a greater initial increase from baseline in blood eosinophil count compared to subjects receiving placebo. In adult subjects with AD (SOLO 1, SOLO 2, and AD-1021), the mean and median increases in blood eosinophils from baseline to Week 4 were 100 and 0 cells/mcL, respectively. In pediatric subjects less than 6 years old with AD, the mean and median increases from baseline to week 4 were 478 and 90 cells/mcL, respectively.

In adult and pediatric subjects 12 years of age and older with asthma (DRI12544 and QUEST), the mean and median increases in blood eosinophils from baseline to Week 4 were 130 and 10 cells/mcL, respectively. In subjects 6 to 11 years of age with asthma (VOYAGE), the mean and median increases in blood eosinophils from baseline to Week 12 were 124 and 0 cells/mcL, respectively.

In adult subjects with CRSwNP (SINUS-24 and SINUS-52), the mean and median increases in blood eosinophils from baseline to Week 16 were 150 and 50 cells/mcL, respectively.

In subjects with COPD (BOREAS and NOTUS), the mean and median increases in blood eosinophils from baseline to Week 8 were 60 and 0 cells/mcL, respectively.

An increase from baseline in blood eosinophil count was not observed in adult and pediatric subjects 12 years of age and older with EoE treated with DUPIXENT as compared to placebo (Study EoE-1). In pediatric subjects 1 to 11 years of age with EoE (Study EoE-2 Part A), blood eosinophil counts were generally consistent with those observed in Study EoE-1.

In adult and pediatric subjects with CSU (CUPID Study A, Study B, and Study C) treated with DUPIXENT, an increase from baseline in blood eosinophil count was not observed compared to placebo at Week 12.

In subjects with PN (PRIME and PRIME2), the mean and median decrease in blood eosinophils from baseline to Week 4 were 9 and 10 cells/mcL, respectively.

In DUPIXENT-treated subjects with BP in ADEPT, all of whom received background oral corticosteroid (OCS) treatment, the mean and median decrease in blood eosinophils from baseline to Week 4 were 1022 and 485 cells/mcL, respectively.

In the trials for the COPD indication, treatment-emergent eosinophilia (≥500 cells/mcL) was higher in DUPIXENT (41.7%) than in the placebo group (39.4%); none of the cases were associated with clinical symptoms, and treatment-emergent eosinophilia (≥1000 cells/mcL) was higher in DUPIXENT (13.6%) than in the placebo group (8.1%).

Across the trials for AD, asthma, CRSwNP, and CSU indications, the incidence of treatment-emergent eosinophilia (≥500 cells/mcL) was similar in DUPIXENT and placebo groups.

In the trials for the PN indication, the incidence of treatment-emergent eosinophilia (≥500 cells/mcL) was lower in DUPIXENT than in the placebo group.

In the trial for the BP indication, the incidence of treatment-emergent eosinophilia (≥500 cells/mcL) was higher in DUPIXENT (21%) than in the placebo group (11%).

Treatment-emergent eosinophilia (≥5,000 cells/mcL) was observed in <3% of DUPIXENT-treated subjects and <0.5% in subjects receiving placebo (SOLO 1, SOLO 2, and AD-1021; DRI12544, QUEST, and VOYAGE; SINUS-24 and SINUS-52; PRIME and PRIME2; BOREAS and NOTUS; CUPID Study A, B, and C). Blood eosinophil counts declined to near baseline or remained below baseline levels (PRIME and PRIME2; BOREAS and NOTUS; ADEPT) during treatment. In trial AD-1539, treatment-emergent eosinophilia (≥5,000 cells/mcL) was reported in 8% of DUPIXENT-treated subjects and 0% in subjects receiving placebo [see Warnings and Precautions (5.3)].

Cardiovascular Thromboembolic Events

In the 1-year placebo-controlled trial in adult and pediatric subjects 12 years of age and older with asthma (QUEST), cardiovascular thromboembolic events (cardiovascular deaths, non-fatal myocardial infarctions, and non-fatal strokes) were reported in 1 (0.2%) of the DUPIXENT 200 mg Q2W group, 4 (0.6%) of the DUPIXENT 300 mg Q2W group, and 2 (0.3%) of the placebo group.

In the 1-year placebo-controlled trial in subjects with AD (CHRONOS), cardiovascular thromboembolic events (cardiovascular deaths, non-fatal myocardial infarctions, and non-fatal strokes) were reported in 1 (0.9%) of the DUPIXENT + TCS 300 mg Q2W group, 0 (0.0%) of the DUPIXENT + TCS 300 mg QW group, and 1 (0.3%) of the placebo + TCS group.

In the 24-week placebo-controlled trial in adult subjects with CRSwNP (SINUS-24), cardiovascular thromboembolic events (cardiovascular deaths, non-fatal myocardial infarctions, and non-fatal strokes) were reported in 1 (0.7%) of the DUPIXENT group and 0 (0.0%) of the placebo group.

In the 1-year placebo-controlled trial in adult subjects with CRSwNP (SINUS-52), there were no cases of cardiovascular thromboembolic events (cardiovascular deaths, non-fatal myocardial infarctions, and non-fatal strokes) reported in any treatment arm.

In the 24-week placebo-controlled trial in subjects with EoE (Study EoE-1 Parts A and B), there were no cases of cardiovascular thromboembolic events (cardiovascular deaths, non-fatal myocardial infarctions, and non-fatal strokes) reported in any treatment arm.

In the 24-week placebo-controlled trial in subjects with CSU (CUPID Study A, B, and C), there were no cases of cardiovascular thromboembolic events (cardiovascular deaths, non-fatal myocardial infarctions, and non-fatal strokes) reported in any treatment arm.

6.2 Postmarketing Experience

The following adverse reactions have been identified during post-approval use of DUPIXENT. Because these reactions are reported voluntarily from a population of uncertain size, it is not always possible to reliably estimate their frequency or establish a causal relationship to drug exposure.

- Immune system disorders: angioedema
- Musculoskeletal system disorders: psoriatic arthritis
- Skin and subcutaneous tissue disorders: Facial skin reactions, including erythema, rash, scaling, edema, papules, pruritus, burning, and pain; new-onset psoriasis, vasculitis

8 USE IN SPECIFIC POPULATIONS

8.1 Pregnancy

Pregnancy Exposure Registry

There is a pregnancy exposure registry that monitors pregnancy outcomes in women exposed to DUPIXENT during pregnancy.

Healthcare providers and patients may call 1-877-311-8972 or go to https://mothertobaby.org/ongoing-study/dupixent/ to enroll in or to obtain information about the registry.

Risk Summary

Available data from case reports and case series with DUPIXENT use in pregnant women have not identified a drug-associated risk of major birth defects, miscarriage, or adverse maternal or fetal outcomes. Human IgG antibodies are known to cross the placental barrier; therefore, DUPIXENT may be transmitted from the mother to the developing fetus. There are adverse effects on maternal and fetal outcomes associated with asthma in pregnancy (see Clinical Considerations). In an enhanced pre- and post-natal developmental study, no adverse developmental effects were observed in offspring born to pregnant monkeys after subcutaneous administration of a homologous antibody against interleukin-4-receptor alpha (IL-4Rα) during organogenesis through parturition at doses up to 10-times the maximum recommended human dose (MRHD) (see Data).

The background risk of major birth defects and miscarriage for the indicated populations are unknown. All pregnancies have a background risk of birth defect, loss or other adverse outcomes. In the U.S. general population, the estimated background risk of major birth defects and miscarriage in clinically recognized pregnancies is 2% to 4% and 15% to 20%, respectively.

Clinical Considerations

Disease-Associated Maternal and/or Embryo-fetal Risk

In women with poorly or moderately controlled asthma, evidence demonstrates that there is an increased risk of preeclampsia in the mother and prematurity, low birth weight, and small for gestational age in the neonate. The level of asthma control should be closely monitored in pregnant women and treatment adjusted as necessary to maintain optimal control.

Fetal/Neonatal Adverse Reactions

Transport of endogenous IgG antibodies across the placenta increases as pregnancy progresses, and peaks during the third trimester. Therefore, DUPIXENT may be present in infants exposed in utero. The potential clinical impact of dupilumab exposure in infants exposed in utero should be considered.

Data

Animal Data

In an enhanced pre- and post-natal development toxicity study, pregnant cynomolgus monkeys were administered weekly subcutaneous doses of homologous antibody against IL-4Rα up to 10 times the MRHD (on a mg/kg basis of 100 mg/kg/week) from the beginning of organogenesis to parturition. No treatment-related adverse effects on embryo-fetal toxicity or malformations, or on morphological, functional, or immunological development were observed in the infants from birth through 6 months of age.

8.2 Lactation

Risk Summary

There are no data on the presence of dupilumab in human milk, the effects on the breastfed infant, or the effects on milk production. Maternal IgG is known to be present in human milk. The effects of local gastrointestinal exposure and limited systemic exposure to dupilumab on the breastfed infant are unknown. The developmental and health benefits of breastfeeding should be considered along with the mother's clinical need for DUPIXENT and any potential adverse effects on the breastfed child from DUPIXENT or from the underlying maternal condition.

8.4 Pediatric Use

Atopic Dermatitis

The safety and effectiveness of DUPIXENT have been established in pediatric patients 6 months of age and older with moderate-to-severe AD, whose disease is not adequately controlled with topical prescription therapies or when those therapies are not advisable.

Use of DUPIXENT in this age group is supported by data from the following clinical trials:

- AD-1526 which included 251 pediatric subjects 12 years of age and older with moderate-to-severe AD. Of the 251 subjects, 82 were treated with DUPIXENT 200 mg Q2W (<60 kg) or 300 mg Q2W (≥60 kg) and 85 were treated with matching placebo
- AD-1652 which included 367 pediatric subjects 6 to 11 years of age with severe AD. Of the 367 subjects, 120 were treated with DUPIXENT 300 mg Q4W + TCS (15 to <30 kg) or 200 mg Q2W + TCS (≥30 kg) and 123 were treated with matching placebo + TCS
- AD-1539 which included 162 pediatric subjects 6 months to 5 years of age with moderate-to-severe AD. Of the 162 subjects, 83 were treated with DUPIXENT 200 mg Q4W + TCS (5 to <15 kg) or 300 mg Q4W + TCS (15 to <30 kg) and 79 subjects were assigned to be treated with matching placebo + TCS
- AD-1434, an open-label extension study that enrolled 275 pediatric subjects 12 years of age and older treated with DUPIXENT ± TCS, 368 pediatric subjects 6 to 11 years of age treated with DUPIXENT ± TCS, and 180 pediatric subjects 6 months to 5 years of age treated with DUPIXENT ± TCS
- Liberty-AD-HAFT which included 27 pediatric subjects 12 years of age and older with atopic dermatitis with moderate-to-severe hand and/or foot involvement treated with DUPIXENT (N=14) or matching placebo (N=13)

The safety and effectiveness were generally consistent between pediatric and adult patients. In addition, hand-foot-and-mouth disease was reported in 9 (5%) pediatric subjects and skin papilloma was reported in 4 (2%) pediatric subjects 6 months to 5 years of age treated with DUPIXENT ± TCS in AD-1434. These cases did not lead to study drug discontinuation [see Adverse Reactions (6.1) and Clinical Studies (14.1)].

Safety and effectiveness of DUPIXENT have not been established in pediatric patients younger than 6 months of age with AD.

Asthma

The safety and effectiveness of DUPIXENT for an add-on maintenance treatment in patients with moderate-to-severe asthma characterized by an eosinophilic phenotype or with oral corticosteroid dependent asthma have been established in pediatric patients 6 years of age and older. Use of DUPIXENT for this indication is supported by evidence from adequate and well-controlled studies in adult and pediatric patients 6 years and older [see Clinical Studies (14.2)].

Pediatric Subjects 12 to 17 Years of Age:

A total of 107 pediatric subjects 12 to 17 years of age with moderate-to-severe asthma were enrolled in QUEST and received either 200 mg (N=21) or 300 mg (N=18) DUPIXENT (or matching placebo either 200 mg [N=34] or 300 mg [N=34]) Q2W. Asthma exacerbations and lung function were assessed in both pediatric subjects 12 to 17 years of age and adults. For both the 200 mg and 300 mg Q2W doses, improvements in FEV1 (LS mean change from baseline at Week 12) were observed (0.36 L and 0.27 L, respectively). For the 200 mg Q2W dose, subjects had a reduction in the rate of severe exacerbations that was consistent with adults. Dupilumab exposure was higher in pediatric subjects 12 to 17 years of age than that in adults at the respective dose level which was mainly accounted for by difference in body weight [see Clinical Pharmacology (12.3)].

The adverse event profile in pediatric subjects 12 to 17 years of age was generally similar to the adults [see Adverse Reactions (6.1)].

Pediatric Subjects 6 to 11 Years of Age:

A total of 408 pediatric subjects 6 to 11 years of age with moderate-to-severe asthma were enrolled in VOYAGE, which evaluated doses of 100 mg Q2W or 200 mg Q2W. Improvement in asthma exacerbations and lung function were demonstrated [see Clinical Studies (14.2)]. The effectiveness of DUPIXENT 300 mg Q4W in subjects 6 to 11 years of age with body weight 15 to <30 kg was extrapolated from efficacy of 100 mg Q2W in VOYAGE with support from population pharmacokinetic analyses showing higher drug exposure levels with 300 mg Q4W [see Clinical Pharmacology (12.3)]. Subjects who completed the treatment period of the VOYAGE study could participate in the open-label extension study (LTS14424). Eighteen subjects (≥15 to <30 kg) out of 365 subjects were exposed to 300 mg Q4W in this study, and the safety profile in these eighteen subjects was consistent with that seen in VOYAGE. Additional safety for DUPIXENT 300 mg Q4W is based upon available safety information from the pediatric AD indication [see Adverse Reactions (6.1) and Clinical Pharmacology (12.3)].

Safety and effectiveness of DUPIXENT have not been established in pediatric patients younger than 6 years of age with asthma.

CRSwNP

The safety and effectiveness of DUPIXENT for add-on maintenance treatment in patients with inadequately controlled chronic rhinosinusitis with nasal polyps (CRSwNP) have been established in pediatric patients aged 12 years and older. Use of DUPIXENT for this indication is supported by evidence from adequate and well-controlled studies of DUPIXENT as add-on maintenance treatment in adults with inadequately controlled CRSwNP (SINUS-24 and SINUS-52) with the following additional data:

- Pharmacokinetic (PK) data from adult and pediatric patients aged 12 years and older with moderate-to-severe asthma and adult patients with inadequately controlled CRSwNP
- Safety data in pediatric patients aged 12 years and older with moderate-to-severe asthma [see Adverse Reactions (6.1), Clinical Pharmacology (12.3), and Clinical Studies (14.3)]

Safety and effectiveness of DUPIXENT have not been established in pediatric patients younger than 12 years of age with CRSwNP.

EoE

The safety and effectiveness of DUPIXENT for the treatment of EoE have been established in pediatric subjects 1 year of age and older, weighing at least 15 kg. Use of DUPIXENT in this population is supported by an adequate well-controlled study in adults and 72 pediatric subjects 12 to 17 years of age (Study EoE-1), a clinical study in 61 pediatric subjects 1 to 11 years of age (Study EoE-2), and pharmacokinetic data in adult and pediatric subjects 1 to 17 years of age. The safety of DUPIXENT in pediatric subjects 1 to 17 years of age was similar to adults [see Adverse Reactions (6.1), Clinical Pharmacology (12.3), and Clinical Studies (14.4)].

Safety and effectiveness of DUPIXENT have not been established in pediatric patients younger than 1 year of age, or weighing less than 15 kg, with EoE.

Prurigo Nodularis

Safety and effectiveness of DUPIXENT have not been established in pediatric patients with PN.

Chronic Obstructive Pulmonary Disease

The safety and effectiveness of DUPIXENT have not been established in pediatric patients with COPD. COPD is largely a disease of adult patients.

Chronic Spontaneous Urticaria

The safety and effectiveness of DUPIXENT for the treatment of CSU in patients who remain symptomatic despite H1 antihistamine treatment have been established in pediatric patients 12 years of age and older. The use of DUPIXENT in this indication is supported by evidence from two adequate and well-controlled studies in adults with additional pharmacokinetic data in 6 pediatric patients 12 years of age and older, and safety data in pediatric patients in other indications [see Dosage and Administration (2.9), Clinical Pharmacology (12.3), and Clinical Studies (14.7)].

Safety and effectiveness of DUPIXENT have not been established in pediatric patients younger than 12 years of age, and/or weighing less than 30 kg, with CSU.

Bullous Pemphigoid

The safety and effectiveness of DUPIXENT have not been established in pediatric patients with BP. BP is largely a disease of adult patients.

8.5 Geriatric Use

Of the 1539 subjects with AD exposed to DUPIXENT in a dose-ranging study and placebo-controlled trials, 70 subjects were 65 years or older. Clinical trials of DUPIXENT in AD did not include sufficient numbers of subjects aged 65 years and older to determine whether they respond differently from younger subjects.

Of the 1977 subjects with asthma exposed to DUPIXENT, a total of 240 subjects were 65 years or older. Efficacy and safety in this age group was similar to the overall study population.

Of the 440 subjects with CRSwNP exposed to DUPIXENT, a total of 79 subjects were 65 years or older. Efficacy and safety in this age group were similar to the overall study population.

Clinical studies of DUPIXENT in EoE did not include sufficient numbers of subjects aged 65 years and older to determine whether they respond differently from younger adult subjects.

Of the 152 subjects with PN exposed to DUPIXENT, a total of 37 were 65 years or older including 8 subjects 75 years or older. Clinical trials did not include a sufficient number of subjects 65 years of age and older to determine whether they respond differently from younger adult subjects.

Of the 1874 subjects with COPD randomized in clinical trials of DUPIXENT, a total of 1072 were 65 years or older, while 244 subjects were 75 years or older. No overall differences in safety or effectiveness of DUPIXENT have been observed between subjects 65 years of age and older and younger adult subjects.

Of the 198 subjects with CSU exposed to DUPIXENT, a total of 30 subjects were 65 years or older, including 7 subjects 75 years or older. Efficacy and safety in subjects 65 years or older were similar to the overall study population.

Of the 53 subjects with BP exposed to DUPIXENT, a total of 40 were 65 years or older, including 22 subjects 75 years or older. Ten percent of subjects aged 65 years and older treated with DUPIXENT had an adverse reaction of vision blurred compared to zero in younger adult subjects.

10 OVERDOSAGE

There is no specific treatment for DUPIXENT overdose. In the event of overdosage, contact Poison Control (1-800-222-1222) for the latest recommendations and monitor the patient for any signs or symptoms of adverse reactions and institute appropriate symptomatic treatment immediately.

11 DESCRIPTION

Dupilumab, an interleukin-4 receptor alpha antagonist, is a human monoclonal antibody of the IgG4 subclass that binds to the IL-4Rα subunit and inhibits IL-4 and IL-13 signaling. Dupilumab has an approximate molecular weight of 147 kDa.

Dupilumab is produced by recombinant DNA technology in Chinese Hamster Ovary cell suspension culture.

DUPIXENT (dupilumab) Injection is supplied as a sterile, preservative-free, clear to slightly opalescent, colorless to pale yellow solution for subcutaneous injection. DUPIXENT is provided as either a single-dose pre-filled syringe with needle shield or a single-dose pre-filled pen in a siliconized Type-1 clear glass syringe. The needle cap is not made with natural rubber latex.

Each 300 mg pre-filled syringe or pre-filled pen delivers 300 mg dupilumab in 2 mL which also contains L-arginine hydrochloride (10.5 mg), L-histidine (6.2 mg), polysorbate 80 (4 mg), sodium acetate (2 mg), sucrose (100 mg), and water for injection, pH 5.9.

Each 200 mg pre-filled syringe or pre-filled pen delivers 200 mg dupilumab in 1.14 mL which also contains L-arginine hydrochloride (12 mg), L-histidine (3.5 mg), polysorbate 80 (2.3 mg), sodium acetate (1.2 mg), sucrose (57 mg), and water for injection, pH 5.9.

12 CLINICAL PHARMACOLOGY

12.1 Mechanism of Action

Dupilumab is a human monoclonal IgG4 antibody that inhibits interleukin-4 (IL-4) and interleukin-13 (IL-13) signaling by specifically binding to the IL-4Rα subunit shared by the IL-4 and IL-13 receptor complexes. Dupilumab inhibits IL-4 signaling via the Type I receptor and both IL-4 and IL-13 signaling through the Type II receptor.

Inflammation driven by IL-4 and IL-13 is an important component in the pathogenesis of asthma, AD, CRSwNP, EoE, PN, COPD, CSU, and BP. Multiple cell types that express IL-4Rα (e.g., mast cells, basophils, eosinophils, macrophages, lymphocytes, epithelial cells, goblet cells) and inflammatory mediators (e.g., histamine, eicosanoids, leukotrienes, cytokines, chemokines) are involved in inflammation. Blocking IL-4Rα with dupilumab inhibits IL-4 and IL-13 cytokine-induced inflammatory responses, including the release of proinflammatory cytokines, chemokines, nitric oxide, and IgE. The mechanism of dupilumab action has not been definitively established.

12.2 Pharmacodynamics

Consistent with inhibition of IL-4 and IL-13 signaling, dupilumab treatment decreased certain biomarkers of inflammation. In asthma subjects, fractional exhaled nitric oxide (FeNO) and circulating concentrations of eotaxin-3, total IgE, allergen specific IgE, TARC, and periostin were decreased relative to placebo. Reductions in these biomarkers were comparable for the 300 mg Q2W and 200 mg Q2W regimens. These markers were near maximal suppression after 2 weeks of treatment, except for IgE which declined more slowly. These effects were sustained throughout treatment. The median percent reduction from baseline in total IgE concentrations with dupilumab treatments was 52% at Week 24 (DRI12544) and 70% at Week 52 (QUEST). For FeNO, the mean percent reduction from baseline at Week 2 was 35% and 24% in DRI12544 and QUEST, respectively, and in the overall safety population, the mean FeNO level decreased to 20 ppb.

A continuous decline in total IgE in serum was observed in CSU trials.

Antibody Response to Non-Live Vaccines During DUPIXENT Treatment

In a clinical study, adult subjects with AD were treated once weekly for 16 weeks with 300 mg of DUPIXENT (twice the recommended dosing frequency). After 12 weeks of administration, subjects received a Tdap vaccine and a meningococcal polysaccharide vaccine. Antibody responses to tetanus toxoid and serogroup C meningococcal polysaccharide were assessed 4 weeks later. Antibody responses to both tetanus toxoid and serogroup C meningococcal polysaccharide were similar in DUPIXENT-treated and placebo-treated subjects. Antibody responses to the other active components of both vaccines were not assessed. Antibody responses to other non-live vaccines were also not assessed.

12.3 Pharmacokinetics

The pharmacokinetics of dupilumab is similar in subjects with AD, asthma, CRSwNP, EoE, PN, COPD, CSU, and BP.

Absorption

Following an initial subcutaneous (SC) dose of 600 mg, 400 mg, or 300 mg, dupilumab reached peak mean ± SD concentrations (Cmax) of 70.1±24.1 mcg/mL, 41.8±12.4 mcg/mL, or 30.5±9.39 mcg/mL, respectively, by approximately 1 week post dose. Steady-state concentrations were achieved by Week 16 following the administration of 600 mg starting dose and 300 mg dose either weekly or Q2W, or 400 mg starting dose and 200 mg dose Q2W, or 300 mg Q2W without a loading dose. Across clinical trials, the mean ± SD steady-state trough concentrations ranged from 55.3±34.3 mcg/mL to 80.2±35.3 mcg/mL for 300 mg administered Q2W, from 173±75.9 mcg/mL to 195±71.7 mcg/mL for 300 mg administered weekly, and from 29.2±18.7 to 36.5±22.2 mcg/mL for 200 mg administered Q2W.

The bioavailability of dupilumab following a SC dose is similar between AD, asthma, CRSwNP, EoE, PN, COPD, CSU, and BP subjects, ranging between 61% and 66%.

Distribution

The estimated total volume of distribution was approximately 4.8±1.3 L.

Elimination

The metabolic pathway of dupilumab has not been characterized. As a human monoclonal IgG4 antibody, dupilumab is expected to be degraded into small peptides and amino acids via catabolic pathways in the same manner as endogenous IgG. After the last steady-state dose of 300 mg QW, 300 mg Q2W, 200 mg Q2W, 300 mg Q4W, or 200 mg Q4W dupilumab, the median times to non-detectable concentration (<78 ng/mL) ranged from 9 to 13 weeks in adults and pediatric subjects 12 years of age and older. Population pharmacokinetic analyses indicate the median times to non-detectable concentration are approximately 1.5 times (up to 19 weeks) and 2.5 times (up to 32 weeks) longer in pediatric subjects 6 to 11 years of age and pediatric subjects 6 months to 5 years of age, respectively.

Dose Linearity

Dupilumab exhibited nonlinear target-mediated pharmacokinetics with exposures increasing in a greater than dose-proportional manner. The systemic exposure increased by 30-fold when the dose increased 8-fold following a single dose of dupilumab from 75 mg to 600 mg (i.e., 0.25-times to 2-times the recommended dose).

Weight

Dupilumab trough concentrations were lower in subjects with higher body weight.

Immunogenicity

Development of antibodies to dupilumab was associated with lower serum dupilumab concentrations. A few subjects who had high antibody titers also had no detectable serum dupilumab concentrations.

Specific Populations

Age

Based on population pharmacokinetic analysis, age did not affect dupilumab clearance in adults and in pediatric subjects 6 to 17 years of age. In pediatric subjects 6 months to 5 years of age, clearance increased with age.

Geriatric Patients

No overall differences in the pharmacokinetics of dupilumab were observed between elderly and younger adult subjects.

Pediatric Patients

Atopic Dermatitis

For pediatric subjects 12 years of age and older with AD receiving every 2 week dosing (Q2W) with either 200 mg (<60 kg) or 300 mg (≥60 kg), the mean ± SD steady-state trough concentration of dupilumab was 54.5±27.0 mcg/mL.

For pediatric subjects 6 to 11 years of age with AD receiving every 2 week dosing (Q2W) with 200 mg (≥30 kg) or every 4 week dosing (Q4W) with 300 mg (<30 kg), mean ± SD steady-state trough concentration was 86.0±34.6 mcg/mL and 98.7±33.2 mcg/mL, respectively.

For pediatric subjects 6 months to 5 years of age with AD receiving every 4 week dosing (Q4W) with 300 mg (≥15 to <30 kg) or 200 mg (≥5 to <15 kg), the mean ± SD steady-state trough concentration was 110±42.8 mcg/mL and 109±50.8 mcg/mL, respectively.

Asthma

A total of 107 pediatric subjects 12 to 17 years of age with asthma were enrolled in QUEST. The mean ± SD steady-state trough concentrations of dupilumab were 107±51.6 mcg/mL and 46.7±26.9 mcg/mL, respectively, for 300 mg or 200 mg administered Q2W.

In VOYAGE, dupilumab pharmacokinetics was investigated in 270 subjects with moderate-to-severe asthma following subcutaneous administration of either 100 mg Q2W (for 91 pediatric subjects weighing <30 kg) or 200 mg Q2W (for 179 pediatric subjects weighing ≥30 kg). The mean ± SD steady-state trough concentration was 58.4±28.0 mcg/mL and 85.1±44.9 mcg/mL, respectively. Simulation of a 300 mg Q4W subcutaneous dose in pediatric subjects 6 to 11 years of age with body weight of ≥15 to <30 kg resulted in predicted steady-state trough concentrations (98.7±41.0 mcg/mL) and average concentrations higher than the observed trough concentrations and average concentrations of 100 mg Q2W (<30 kg).

CRSwNP

Clinical studies have not been conducted in pediatric patients aged 12 years and older with CRSwNP. Dupilumab exposures are expected to be comparable between adults and pediatric patients aged 12 years and older at the recommended dosage for CRSwNP (300 mg every 2 weeks).

Eosinophilic Esophagitis

In Study EoE-1, dupilumab pharmacokinetics were investigated in 35 pediatric subjects 12 to 17 years of age, weighing at least 40 kg, with EoE, receiving 300 mg QW. The mean ± SD steady-state trough concentration of dupilumab was 227±95.3 mcg/mL.

In Study EoE-2 Part A, dupilumab pharmacokinetics were investigated in 20 pediatric subjects 1 to 11 years of age with EoE receiving the following weight-based dosing regimens: ≥15 to <30 kg (200 mg Q2W) and ≥30 to <40 kg (300 mg Q2W). At Week 16, the mean ± SD steady-state trough concentration of dupilumab was 174±66.2 mcg/mL.

The systemic exposure in pediatric subjects 1 to 11 years of age with a body weight ≥40 kg receiving 300 mg QW is expected to be comparable to adult and pediatric subjects 12 years and older with a body weight ≥40 kg. The systemic exposure in pediatric subjects 12 to 17 years of age with a body weight <40 kg receiving 300 mg Q2W is expected to be comparable to pediatric subjects 6 to 11 years of age.

Chronic Spontaneous Urticaria

A total of 12 pediatric subjects 12 to 17 years of age with CSU were enrolled in CUPID. The observed steady-state trough concentrations of 6 pediatric subjects 12 to 17 years of age with CSU who received DUPIXENT 300 mg Q2W or 200 mg Q2W were within the range of steady-state trough concentrations in adult subjects with CSU who received DUPIXENT 300 mg Q2W.

Drug Interaction Studies

An effect of dupilumab on the PK of co-administered medications is not expected. Based on the population analysis, commonly co-administered medications had no effect on DUPIXENT pharmacokinetics in subjects with moderate-to-severe asthma.

Cytochrome P450 Substrates

The effects of dupilumab on the pharmacokinetics of midazolam (metabolized by CYP3A4), warfarin (metabolized by CYP2C9), omeprazole (metabolized by CYP2C19), metoprolol (metabolized by CYP2D6), and caffeine (metabolized by CYP1A2) were evaluated in a study with 12-13 evaluable subjects with AD (a SC loading dose of 600 mg followed by 300 mg SC weekly for six weeks). No clinically significant changes in AUC were observed. The largest effect was observed for metoprolol (CYP2D6) with an increase in AUC of 29%.

12.6 Immunogenicity

The observed incidence of anti-drug antibodies is highly dependent on the sensitivity and specificity of the assay. Differences in assay methods preclude meaningful comparisons of the incidence of anti-drug antibodies in the trials described below with the incidence of anti-drug antibodies in other trials, including those of DUPIXENT or of other dupilumab products.

The anti-drug antibody (ADA) and neutralizing antibody (NAb) incidence rates in subjects treated with DUPIXENT are presented in Table 15.

Table 15: Anti-drug Antibody and Neutralizing Antibody Incidence in Subjects Treated with DUPIXENT
Indication and Population | Dose and Duration of Treatment | Anti-drug Antibody (ADA) |  | Neutralizing Antibody NAb [Neutralizing potential is assessed only for ADA-positive samples. The NAb incidence is reported as a percentage of subjects with treatment emergent ADA.]
Indication and Population | Dose and Duration of Treatment | Treatment-Emergent ADA [Treatment-emergent ADA: A negative result or missing result at baseline with at least 1 positive post-baseline result in the ADA assay.] | Persistent ADA [Persistent ADA: A treatment-emergent ADA positive response with 2 or more consecutive ADA positive samples separated by a greater than 12-week period (>84 days), with no ADA negative result in between.] | Neutralizing Antibody NAb [Neutralizing potential is assessed only for ADA-positive samples. The NAb incidence is reported as a percentage of subjects with treatment emergent ADA.]
Atopic Dermatitis
Adult | 300 mg Q2W for 52 weeks | 6/105 (6%) | 2/105 (2%) | 1/6 (17%)
12 to 17 years of age | 300 mg or 200 mg Q2W for 16 weeks | 13/81 (16%) | 2/81 (3%) | 4/13 (31%)
6 to 11 years of age | 200 mg Q2W or 300 mg Q4W for 16 weeks | 3/171 (2%) | 0/171 (0%) | 1/3 (33%)
6 months to 5 years of age | 200 mg Q4W, or 300 mg Q4W for 16 weeks | 1/74 (1%) | 0/74 (0%) | 0/1 (0%)
Asthma
Adult and 12 years of age or older | 300 mg Q2W for 52 weeks | 32/626 (5%) | 13/626 (2%) | 14/32 (44%)
Adult and 12 years of age or older | 200 mg Q2W for 52 weeks | 58/625 (9%) | 26/625 (4%) | 27/58 (47%)
6 to 11 years of age | 100 mg Q2W or 200 mg Q2W up to 52 weeks | 17/269 (6%) | 9/269 (3%) | 6/17 (35%)
Chronic Rhinosinusitis with Nasal Polyps
Adult | 300 mg Q2W for 52 weeks | 8/148 (5%) | 3/148 (2%) | 5/8 (63%)
Eosinophilic Esophagitis
Adult and 12 years of age or older | 300 mg QW for 52 weeks | 1/108 (1%) | 0/108 (0%) | 0/1 (0%)
1 to 11 years of age | 200 mg Q2W or 300 mg Q2W for 52 weeks [Immunogenicity was reported on pooled data for pediatric subjects 1 to 11 years of age with EoE receiving SC dupilumab 100 mg Q2W (in subjects weighing ≥5 kg to <15kg), 200 mg Q2W (in subjects weighing ≥15 kg to <30 kg), 300 mg Q2W (in subjects weighing ≥30 kg to <60 kg), and 300 mg QW (in subjects weighing ≥60 kg).] | 1/37 (3%) | 0/37 (0%) | 0/1 (0%) [One subject 1 to 11 years of age with EoE with pre-existing immunoreactivity that was positive for neutralizing antibodies was excluded from the NAb positive subjects.]
Prurigo Nodularis
Adult | 300 mg Q2W for 24 weeks | 11/143 (8%) | 2/143 (1%) | 4/11 (36%)
Chronic Obstructive Pulmonary Disease
Adult | 300 mg Q2W for 52 weeks | 77/922 (8%) | 24/922 (3%) | 28/77 (36%)
Chronic Spontaneous Urticaria
Adult and 12 years of age or older | 200 mg Q2W or 300 mg Q2W through 24 weeks | 9/193 (5%) | 1/193 (1%) | 2/9 (22%)
Bullous Pemphigoid
Adult | 300 mg Q2W up to 52 weeks | 2/52 (4%) | 0/52 (0%) | 2/2 (100%)

Two adult subjects with AD who experienced high titer antibody responses developed serum sickness or serum sickness-like reactions during DUPIXENT therapy [see Warnings and Precautions (5.1)].

The antibody titers detected in subjects who received DUPIXENT were mostly low. In subjects who received DUPIXENT, development of high titer antibodies to DUPIXENT was associated with lower serum dupilumab concentrations [see Clinical Pharmacology (12.3)].

13 NONCLINICAL TOXICOLOGY

13.1 Carcinogenesis, Mutagenesis, Impairment of Fertility

Animal studies have not been conducted to evaluate the carcinogenic or mutagenic potential of dupilumab.

No effects on fertility parameters such as reproductive organs, menstrual cycle length, or sperm analysis were observed in sexually mature mice that were subcutaneously administered a homologous antibody against IL-4Rα at doses up to 200 mg/kg/week.

14 CLINICAL STUDIES

14.1 Atopic Dermatitis

Adults with Atopic Dermatitis

Three randomized, double-blind, placebo-controlled trials (SOLO 1 (NCT02277743), SOLO 2 (NCT02277769), and CHRONOS (NCT02260986)) enrolled a total of 2119 adult subjects with moderate-to-severe AD not adequately controlled by topical medication(s). Disease severity was defined by an Investigator's Global Assessment (IGA) score ≥3 in the overall assessment of AD lesions on a severity scale of 0 to 4, an Eczema Area and Severity Index (EASI) score ≥16 on a scale of 0 to 72, and a minimum body surface area involvement of ≥10%. At baseline, the mean age of subjects was 38 years; 59% of subjects were male, 67% were White, 24% were Asian, and 6% were Black; 52% of subjects had a baseline IGA score of 3 (moderate AD), and 48% of subjects had a baseline IGA of 4 (severe AD). The baseline mean EASI score was 33 and the baseline weekly averaged Peak Pruritus Numeric Rating Scale (NRS) was 7 on a scale of 0-10.

In all three trials, subjects in the DUPIXENT group received subcutaneous injections of DUPIXENT 600 mg at Week 0, followed by 300 mg every 2 weeks (Q2W). In the monotherapy trials (SOLO 1 and SOLO 2), subjects received DUPIXENT or placebo for 16 weeks.

In the concomitant therapy trial (CHRONOS), subjects received DUPIXENT or placebo with concomitant topical corticosteroids (TCS) and as needed topical calcineurin inhibitors for problem areas only, such as the face, neck, intertriginous and genital areas for 52 weeks.

All three trials assessed the primary endpoint, the change from baseline to Week 16 in the proportion of subjects with an IGA 0 (clear) or 1 (almost clear) and at least a 2-point improvement. Other endpoints included the proportion of subjects with EASI-75 (improvement of at least 75% in EASI score from baseline), and reduction in itch as defined by at least a 4-point improvement in the Peak Pruritus NRS from baseline to Week 16.

Clinical Response at Week 16 (SOLO 1, SOLO 2, and CHRONOS)

The results of the DUPIXENT monotherapy trials (SOLO 1 and SOLO 2) and the DUPIXENT with concomitant TCS trial (CHRONOS) are presented in Table 16.

Table 16: Efficacy Results of DUPIXENT with or without Concomitant TCS at Week 16 (FAS) in Adult Subjects with Moderate-to-Severe AD
 | SOLO 1 |  | SOLO 2 |  | CHRONOS
 | DUPIXENT 300 mg Q2W | Placebo | DUPIXENT 300 mg Q2W | Placebo | DUPIXENT 300 mg Q2W + TCS | Placebo + TCS
Number of subjects randomized (FAS) [Full Analysis Set (FAS) includes all subjects randomized.] | 224 | 224 | 233 | 236 | 106 | 315
IGA 0 or 1 [Responder was defined as a subject with an IGA 0 or 1 ("clear" or "almost clear") and a reduction of ≥2 points on a 0-4 IGA scale.] , [Subjects who received rescue treatment or with missing data were considered as non-responders.] | 38% | 10% | 36% | 9% | 39% | 12%
EASI-75 | 51% | 15% | 44% | 12% | 69% | 23%
EASI-90 | 36% | 8% | 30% | 7% | 40% | 11%
Number of subjects with baseline Peak Pruritus NRS score ≥4 | 213 | 212 | 225 | 221 | 102 | 299
Peak Pruritus NRS (≥4-point improvement) | 41% | 12% | 36% | 10% | 59% | 20%

Figure 1: Proportion of Adult Subjects with Moderate-to-Severe AD with ≥4-point Improvement on the Peak Pruritus NRS in SOLO 1 [In the primary analyses of the efficacy endpoints, subjects who received rescue treatment or with missing data were considered non-responders.] and SOLO 2 Studies (FAS) [Full Analysis Set (FAS) includes all subjects randomized.]

SOLO 1

SOLO 2

In CHRONOS, of the 421 subjects, 353 had been on study for 52 weeks at the time of data analysis. Of these 353 subjects, responders at Week 52 represent a mixture of subjects who maintained their efficacy from Week 16 (e.g., 53% of DUPIXENT IGA 0 or 1 responders at Week 16 remained responders at Week 52) and subjects who were non-responders at Week 16 who later responded to treatment (e.g., 24% of DUPIXENT IGA 0 or 1 non-responders at Week 16 became responders at Week 52). Results of supportive analyses of the 353 subjects in the DUPIXENT with concomitant TCS trial (CHRONOS) are presented in Table 17.

Table 17: Efficacy Results (IGA 0 or 1) of DUPIXENT with Concomitant TCS at Week 16 and 52 in Adult Subjects with Moderate-to-Severe AD
 | DUPIXENT 300 mg Q2W + TCS | Placebo + TCS
Number of Subjects [In CHRONOS, of the 421 randomized and treated subjects, 68 subjects (16%) had not been on study for 52 weeks at the time of data analysis.] | 89 | 264
Responder [Responder was defined as a subject with an IGA 0 or 1 ("clear" or "almost clear") and a reduction of ≥2 points on a 0-4 IGA scale.] , [Subjects who received rescue treatment or with missing data were considered as non-responders.] at Week 16 and 52 | 22% | 7%
Responder at Week 16 but Non-responder at Week 52 | 20% | 7%
Non-responder at Week 16 and Responder at Week 52 | 13% | 6%
Non-responder at Week 16 and 52 | 44% | 80%
Overall Responder, Rate at Week 52 | 36% | 13%

Treatment effects in subgroups (weight, age, gender, race, and prior treatment, including immunosuppressants) in SOLO 1, SOLO 2, and CHRONOS were generally consistent with the results in the overall study population.

In SOLO 1, SOLO 2, and CHRONOS, a third randomized treatment arm of DUPIXENT 300 mg QW did not demonstrate additional treatment benefit over DUPIXENT 300 mg Q2W.

Subjects in SOLO 1 and SOLO 2 who had an IGA 0 or 1 with a reduction of ≥2 points were re-randomized into SOLO CONTINUE (NCT02395133). SOLO CONTINUE evaluated multiple DUPIXENT monotherapy dose regimens for maintaining treatment response. The study included subjects randomized to continue with DUPIXENT 300 mg Q2W (62 subjects) or switch to placebo (31 subjects) for 36 weeks. IGA 0 or 1 responses at Week 36 were as follows: 33 (53%) in the Q2W group and 3 (10%) in the placebo group.

Pediatric Subjects 12 Years of Age and Older with Atopic Dermatitis

The efficacy of DUPIXENT monotherapy in pediatric subjects 12 years of age and older was evaluated in a multicenter, randomized, double-blind, placebo-controlled trial (AD-1526; NCT03054428) in 251 pediatric subjects 12 to 17 years of age, with moderate-to-severe AD defined by an IGA score ≥3 (scale of 0 to 4), an EASI score ≥16 (scale of 0 to 72), and a minimum BSA involvement of ≥10%. Eligible subjects enrolled into this trial had previous inadequate response to topical medication.

Subjects in the DUPIXENT group with baseline weight of <60 kg received an initial dose of 400 mg at Week 0, followed by 200 mg Q2W for 16 weeks. Subjects with baseline weight of ≥60 kg received an initial dose of 600 mg at Week 0, followed by 300 mg Q2W for 16 weeks. Subjects were permitted to receive rescue treatment at the discretion of the investigator. Subjects who received rescue treatment were considered non-responders.

In AD-1526, the mean age was 14.5 years, the median weight was 59.4 kg, 41% of subjects were female, 63% were White, 15% were Asian, and 12% were Black. At baseline, 46% of subjects had an IGA score of 3 (moderate AD), 54% had an IGA score of 4 (severe AD), the mean BSA involvement was 57%, and 42% had received prior systemic immunosuppressants. Also, at baseline, the mean EASI score was 36, and the weekly averaged Peak Pruritus NRS was 8 on a scale of 0-10. Overall, 92% of subjects had at least one co-morbid allergic condition; 66% had allergic rhinitis, 54% had asthma, and 61% had food allergies.

The primary endpoint was the proportion of subjects with an IGA 0 (clear) or 1 (almost clear) and at least a 2-point improvement from baseline to Week 16. Other evaluated outcomes included the proportion of subjects with EASI-75 or EASI-90 (improvement of at least 75% or 90% in EASI from baseline, respectively), and reduction in itch as measured by the Peak Pruritus NRS (≥4-point improvement).

The efficacy results at Week 16 for AD-1526 are presented in Table 18.

Table 18: Efficacy Results of DUPIXENT in AD-1526 at Week 16 (FAS) [Full Analysis Set (FAS) includes all subjects randomized.] in Pediatric Subjects 12 Years of Age and Older with Moderate-to-Severe AD
 | DUPIXENT [At Week 0, subjects received 400 mg (baseline weight <60 kg) or 600 mg (baseline weight ≥60 kg) of DUPIXENT.] 200 mg (<60 kg) or 300 mg (≥60 kg) Q2W N=82 | Placebo N=85
IGA 0 or 1 [Responder was defined as a subject with an IGA 0 or 1 ("clear" or "almost clear") and a reduction of ≥2 points on a 0-4 IGA scale.] , [Subjects who received rescue treatment or with missing data were considered as non-responders (59% and 21% in the placebo and DUPIXENT arms, respectively).] | 24% | 2%
EASI-75 | 42% | 8%
EASI-90 | 23% | 2%
Peak Pruritus NRS (≥4-point improvement) | 37% | 5%

A greater proportion of subjects randomized to DUPIXENT achieved an improvement in the Peak Pruritus NRS compared to placebo (defined as ≥4-point improvement at Week 4). See Figure 2.

Figure 2: Proportion of Pediatric Subjects 12 Years of Age and Older with Moderate-to-Severe AD with ≥4-point Improvement on the Peak Pruritus NRS in AD-1526 [In the primary analyses of the efficacy endpoints, subjects who received rescue treatment or with missing data were considered non-responders.] (FAS) [Full Analysis Set (FAS) includes all subjects randomized.]

Pediatric Subjects 6 to 11 Years of Age with Atopic Dermatitis

The efficacy and safety of DUPIXENT use concomitantly with TCS in pediatric subjects was evaluated in a multicenter, randomized, double-blind, placebo-controlled trial (AD-1652; NCT03345914) in 367 subjects 6 to 11 years of age, with AD defined by an IGA score of 4 (scale of 0 to 4), an EASI score ≥21 (scale of 0 to 72), and a minimum BSA involvement of ≥15%. Eligible subjects enrolled into this trial had previous inadequate response to topical medication. Enrollment was stratified by baseline weight (<30 kg; ≥30 kg).

Subjects in the DUPIXENT Q4W + TCS group received an initial dose of 600 mg on Day 1, followed by 300 mg Q4W from Week 4 to Week 12, regardless of weight. Subjects in the DUPIXENT Q2W + TCS group with baseline weight of <30 kg received an initial dose of 200 mg on Day 1, followed by 100 mg Q2W from Week 2 to Week 14, and subjects with baseline weight of ≥30 kg received an initial dose of 400 mg on Day 1, followed by 200 mg Q2W from Week 2 to Week 14. Subjects were permitted to receive rescue treatment at the discretion of the investigator. Subjects who received rescue treatment were considered non-responders.

In AD-1652, the mean age was 8.5 years, the median weight was 29.8 kg, 50% of subjects were female, 69% were White, 17% were Black, and 8% were Asian. At baseline, the mean BSA involvement was 58%, and 17% had received prior systemic non-steroidal immunosuppressants. Also, at baseline the mean EASI score was 37.9, and the weekly average of daily worst itch score was 7.8 on a scale of 0-10. Overall, 92% of subjects had at least one co-morbid allergic condition; 64% had food allergies, 63% had other allergies, 60% had allergic rhinitis, and 47% had asthma.

The primary endpoint was the proportion of subjects with an IGA 0 (clear) or 1 (almost clear) at Week 16. Other evaluated outcomes included the proportion of subjects with EASI-75 or EASI-90 (improvement of at least 75% or 90% in EASI from baseline, respectively), and reduction in itch as measured by the Peak Pruritus NRS (≥4-point improvement).

Table 19 presents the results by baseline weight strata for the approved dose regimens.

Table 19: Efficacy Results of DUPIXENT with Concomitant TCS in AD-1652 at Week 16 (FAS) [Full Analysis Set (FAS) includes all subjects randomized.] in Pediatric Subjects 6 to 11 Years of Age with AD
 | DUPIXENT 300 mg Q4W [At Day 1, subjects received 600 mg of DUPIXENT.] + TCS | Placebo + TCS | DUPIXENT 200 mg Q2W [At Day 1, subjects received 200 mg (baseline weight <30 kg) or 400 mg (baseline weight ≥30 kg) of DUPIXENT.] + TCS | Placebo + TCS
 | (N=61) | (N=61) | (N=59) | (N=62)
 | <30 kg | <30 kg | ≥30 kg | ≥30 kg
IGA 0 or 1 [Responder was defined as a subject with an IGA 0 or 1 ("clear" or "almost clear").] , [Subjects who received rescue treatment or with missing data were considered as non-responders.] | 30% | 13% | 39% | 10%
EASI-75 | 75% | 28% | 75% | 26%
EASI-90 | 46% | 7% | 36% | 8%
Peak Pruritus NRS (≥4-point improvement) | 54% | 12% | 61% | 13%

A greater proportion of subjects randomized to DUPIXENT + TCS achieved an improvement in the Peak Pruritus NRS compared to placebo + TCS (defined as ≥4-point improvement at Week 16). See Figure 3.

Figure 3: Proportion of Pediatric Subjects 6 to 11 Years of Age with AD with ≥4-point Improvement on the Peak Pruritus NRS at Week 16 in AD-1652 [In the primary analyses of the efficacy endpoints, subjects who received rescue treatment or with missing data were considered non-responders.] (FAS) [Full Analysis Set (FAS) includes all subjects randomized.]

Pediatric Subjects 6 Months to 5 Years of Age with Atopic Dermatitis

The efficacy and safety of DUPIXENT use concomitantly with TCS in pediatric subjects was evaluated in a multicenter, randomized, double-blind, placebo-controlled trial (AD-1539; NCT03346434) in 162 subjects 6 months to 5 years of age, with moderate-to-severe AD defined by an IGA score ≥3 (scale of 0 to 4), an EASI score ≥16 (scale of 0 to 72), and a minimum BSA involvement of ≥10%. Eligible subjects enrolled into this trial had previous inadequate response to topical medication. Enrollment was stratified by baseline weight (≥5 to <15 kg and ≥15 to <30 kg).

Subjects in the DUPIXENT Q4W + TCS group with baseline weight of ≥5 to <15 kg received an initial dose of 200 mg on Day 1, followed by 200 mg Q4W from Week 4 to Week 12, and subjects with baseline weight of ≥15 to <30 kg received an initial dose of 300 mg on Day 1, followed by 300 mg Q4W from Week 4 to Week 12. Subjects were permitted to receive rescue treatment at the discretion of the investigator. Subjects who received rescue treatment were considered non-responders.

In AD-1539, the mean age was 3.8 years, the median weight was 16.5 kg, 39% of subjects were female, 69% were White, 19% were Black, and 6% were Asian. At baseline, the mean BSA involvement was 58%, and 29% of subjects had received prior systemic immunosuppressants. Also, at baseline the mean EASI score was 34.1, and the weekly average of daily worst scratch/itch score was 7.6 on a scale of 0-10. Overall, 81.4% of subjects had at least one co-morbid allergic condition; 68.3% had food allergies, 52.8% had other allergies, 44.1% had allergic rhinitis, and 25.5% had asthma.

The primary endpoint was the proportion of subjects with an IGA 0 (clear) or 1 (almost clear) at Week 16. Other evaluated outcomes included the proportion of subjects with EASI-75 or EASI-90 (improvement of at least 75% or 90% in EASI from baseline, respectively), and reduction in itch as measured by the Worst Scratch/Itch NRS (≥4-point improvement).

The efficacy results at Week 16 for AD-1539 are presented in Table 20.

Table 20: Efficacy Results of DUPIXENT with Concomitant TCS in AD-1539 at Week 16 (FAS) [Full Analysis Set (FAS) includes all subjects randomized.] in Pediatric Subjects 6 Months to 5 Years of Age with Moderate-to-Severe AD
 | DUPIXENT + TCS 200 mg (5 to <15 kg) or 300 mg (15 to <30 kg) Q4W [At Day 1, subjects received 200 mg (5 to <15 kg) or 300 mg (15 to <30 kg) of DUPIXENT.] | Placebo + TCS | Difference vs. Placebo (95 % CI)
 | (N=83) | (N=79)
IGA 0 or 1 [Responder was defined as a subject with an IGA 0 or 1 ("clear" or "almost clear").] , [Subjects who received rescue treatment (63% and 19% in the placebo and DUPIXENT arms, respectively) or with missing data were considered as non-responders.] | 28% | 4% | 24% (13%, 34%)
EASI-75 | 53% | 11% | 42% (29%, 55%)
EASI-90 | 25% | 3% | 23% (12%, 33%)
Worst Scratch/Itch NRS (≥4-point improvement) | 48% | 9% | 39% (26%, 52%)
CI = confidence interval

Atopic Dermatitis with Hand and/or Foot Involvement

The efficacy and safety of DUPIXENT was evaluated in a 16-week, multicenter, randomized, double-blind, parallel-group, placebo-controlled trial (Liberty-AD-HAFT; NCT04417894) in 133 adult and pediatric subjects 12 to 17 years of age with atopic dermatitis with moderate-to-severe hand and/or foot involvement, defined by an established diagnosis of atopic dermatitis and screening to rule out irritant and allergic contact dermatitis through history and appropriate patch testing, and by an IGA (hand and foot) score ≥3 (scale of 0 to 4) and a hand and foot Peak Pruritus Numeric Rating Scale (NRS) score for maximum itch intensity ≥4 (scale of 0 to 10). Fifty-three (53) percent (N=70/133) of the subjects also had moderate-to-severe AD outside of the hands or feet (IGA global ≥3). Eligible subjects had previous inadequate response or intolerance to treatment of hand and/or foot dermatitis with topical AD medications. In this trial 67 subjects received DUPIXENT, and 66 subjects received placebo. DUPIXENT-treated subjects received the recommended dosage based on their age and body weight [see Dosage and Administration (2.3)]. Subjects were not allowed concomitant use of topical treatments for AD on the hands and feet during the trial, but were allowed the use of topical treatments for AD on other parts of the body with certain restrictions.

In Liberty-AD-HAFT, 38% of subjects were male, 80% were White, 13% were Asian, and 5% were Black or African American. For ethnicity, 4% were identified as Hispanic or Latino and 96% were identified as not Hispanic or Latino. Seventy-two (72) percent (N=96/133) of subjects had a baseline IGA (hand and foot) score of 3 (atopic dermatitis with moderate hand and/or foot involvement), and 28% (N=37/133) of subjects had a baseline IGA (hand and foot) score of 4 (atopic dermatitis with severe hand and/or foot involvement). The baseline weekly averaged hand and foot Peak Pruritus NRS score was 7.1.

The primary endpoint was the proportion of subjects with an IGA hand and foot score of 0 (clear) or 1 (almost clear) at Week 16. The key secondary endpoint was reduction of itch as measured by the hand and foot Peak Pruritus NRS (≥4-point improvement).

The efficacy results at Week 16 for Liberty-AD-HAFT are presented in Table 21.

Table 21: Efficacy Results of DUPIXENT in Liberty-AD-HAFT at Week 16 (FAS) [Full Analysis Set (FAS) includes all subjects randomized.] in Adult and Pediatric Subjects 12 Years of Age and Older with AD with Moderate-to-Severe Hand and/or Foot Involvement
 | DUPIXENT 200/300 mg Q2W [Adults received a loading dose of DUPIXENT 600 mg SC followed by 300 mg SC Q2W. Pediatric subjects 12 to 17 years of age received a loading dose of DUPIXENT 600 mg SC followed by 300 mg SC Q2W (for body weight ≥60 kg) or a loading dose of DUPIXENT 400 mg SC followed by 200 mg SC Q2W (for body weight <60 kg).] | Placebo | Difference vs. Placebo (95 % CI)
 | (N=67) | (N=66)
IGA (hand and foot) 0 or 1 [Responder was defined as a subject with an IGA 0 or 1 ("clear" or "almost clear").] , [Subjects who received rescue treatment (21% and 3% in the placebo and DUPIXENT arms, respectively) or with missing data were considered as non-responders.] | 40% | 17% | 24% (9%, 38%)
Improvement (reduction) of weekly averaged hand and foot Peak Pruritus NRS ≥4 | 52% | 14% | 39% (24%, 53%)
CI = confidence interval

14.2 Asthma

The asthma development program for patients aged 12 years and older included three randomized, double-blind, placebo-controlled, parallel-group, multicenter trials (DRI12544 (NCT01854047), QUEST (NCT02414854), and VENTURE (NCT02528214)) of 24 to 52 weeks in treatment duration which enrolled a total of 2888 subjects. Subjects enrolled in DRI12544 and QUEST were required to have a history of 1 or more asthma exacerbations that required treatment with systemic corticosteroids or emergency department visit or hospitalization for the treatment of asthma in the year prior to trial entry. Subjects enrolled in VENTURE required dependence on daily oral corticosteroids in addition to regular use of high-dose inhaled corticosteroids plus an additional controller(s). In all 3 trials, subjects were enrolled without requiring a minimum baseline blood eosinophil count. In QUEST and VENTURE, subjects with screening blood eosinophil level of >1500 cells/mcL (<1.3%) were excluded. DUPIXENT was administered as add-on to background asthma treatment. Subjects continued background asthma therapy throughout the duration of the studies, except in VENTURE in which OCS dose was tapered as described below.

DRI12544

DRI12544 was a 24-week dose-ranging study which included 776 adult subjects (18 years of age and older). DUPIXENT compared with placebo was evaluated in adult subjects with moderate-to-severe asthma on a medium or high-dose inhaled corticosteroid and a long acting beta agonist. Subjects were randomized to receive either 200 mg (N=150) or 300 mg (N=157) DUPIXENT every 2 weeks (Q2W) or 200 mg (N=154) or 300 mg (N=157) DUPIXENT every 4 weeks following an initial dose of 400 mg, 600 mg or placebo (N=158), respectively. The primary endpoint was mean change from baseline to Week 12 in FEV1 (L) in subjects with baseline blood eosinophils ≥300 cells/mcL. Other endpoints included percent change from baseline in FEV1 and annualized rate of severe asthma exacerbation events during the 24-week placebo-controlled treatment period. Results were evaluated in the overall population and subgroups based on baseline blood eosinophil count (≥300 cells/mcL and <300 cells/mcL). Additional secondary endpoints included responder rates in the patient reported Asthma Control Questionnaire (ACQ-5) and Asthma Quality of Life Questionnaire, Standardized Version (AQLQ(S)) scores.

QUEST

QUEST was a 52-week study which included 1902 adult and pediatric subjects (12 years of age and older). DUPIXENT compared with placebo was evaluated in 107 pediatric subjects 12 to 17 years of age and 1795 adult subjects with moderate-to-severe asthma on a medium or high-dose inhaled corticosteroid (ICS) and a minimum of one and up to two additional controller medications. Subjects were randomized to receive either 200 mg (N=631) or 300 mg (N=633) DUPIXENT Q2W (or matching placebo for either 200 mg [N=317] or 300 mg [N=321] Q2W) following an initial dose of 400 mg, 600 mg or placebo, respectively. The primary endpoints were the annualized rate of severe exacerbation events during the 52-week placebo-controlled period and change from baseline in pre-bronchodilator FEV1 at Week 12 in the overall population (unrestricted by minimum baseline blood eosinophils count). Additional secondary endpoints included annualized severe exacerbation rates and FEV1 in subjects with different baseline levels of blood eosinophils as well as responder rates in the ACQ-5 and AQLQ(S) scores.

VENTURE

VENTURE was a 24-week oral corticosteroid-reduction study in 210 adult and pediatric subjects 15 years of age and older with asthma who required daily oral corticosteroids in addition to regular use of high dose inhaled corticosteroids plus an additional controller. After optimizing the OCS dose during the screening period, subjects received 300 mg DUPIXENT (N=103) or placebo (N=107) once Q2W for 24 weeks following an initial dose of 600 mg or placebo. Subjects continued to receive their existing asthma medicine during the study; however, their OCS dose was reduced every 4 weeks during the OCS reduction phase (Week 4-20), as long as asthma control was maintained. The primary endpoint was the percent reduction of oral corticosteroid dose at Weeks 20 to 24 compared with the baseline dose, while maintaining asthma control in the overall population (unrestricted by minimum baseline blood eosinophils count). Additional secondary endpoints included the annualized rate of severe exacerbation events during treatment period and responder rate in the ACQ-5 and AQLQ(S) scores.

The demographics and baseline characteristics of these 3 trials are provided in Table 22 below.

Table 22: Demographics and Baseline Characteristics of Asthma Trials
Parameter | DRI12544 (N=776) | QUEST (N=1902) | VENTURE (N=210)
Mean age (years) (SD) | 49 (13) | 48 (15) | 51 (13)
% Female | 63 | 63 | 61
% White | 78 | 83 | 94
Duration of Asthma (years), mean (± SD) | 22 (15) | 21 (15) | 20 (14)
Never smoked (%) | 77 | 81 | 81
Mean exacerbations in previous year (± SD) | 2.2 (2.1) | 2.1 (2.2) | 2.1 (2.2)
High dose ICS use (%) | 50 | 52 | 89
Pre-dose FEV1 (L) at baseline (± SD) | 1.84 (0.54) | 1.78 (0.60) | 1.58 (0.57)
Mean percent predicted FEV1 at baseline (%) (± SD) | 61 (11) | 58 (14) | 52 (15)
% Reversibility (± SD) | 27 (15) | 26 (22) | 19 (23)
Atopic Medical History % Overall (AD %, NP %, AR %) | 73 (8, 11, 62) | 78 (10, 13, 69) | 72 (8, 21, 56)
Mean FeNO ppb (± SD) | 39 (35) | 35 (33) | 38 (31)
Mean total IgE IU/mL (± SD) | 435 (754) | 432 (747) | 431 (776)
Mean baseline blood Eosinophil count (± SD) cells/mcL | 350 (430) | 360 (370) | 350 (310)
ICS = inhaled corticosteroid; FEV1 = Forced expiratory volume in 1 second; AD = atopic dermatitis; NP = nasal polyps; AR = allergic rhinitis; FeNO = fraction of exhaled nitric oxide

Exacerbations in Subjects with Asthma

DRI12544 and QUEST evaluated the frequency of severe asthma exacerbations defined as deterioration of asthma requiring the use of systemic corticosteroids for at least 3 days or hospitalization or emergency room visit due to asthma that required systemic corticosteroids. In the primary analysis population (subjects with baseline blood eosinophil count of ≥300 cells/mcL in DRI12544 and the overall population in QUEST), subjects receiving either DUPIXENT 200 mg or 300 mg Q2W had significant reductions in the rate of asthma exacerbations compared to placebo. In the overall population in QUEST, the rate of severe exacerbations was 0.46 and 0.52 for DUPIXENT 200 mg Q2W and 300 mg Q2W, respectively, compared to matched placebo rates of 0.87 and 0.97. The rate ratio of severe exacerbations compared to placebo was 0.52 (95% CI: 0.41, 0.66) and 0.54 (95% CI: 0.43, 0.68) for DUPIXENT 200 mg Q2W and 300 mg Q2W, respectively. Results in subjects with baseline blood eosinophil counts ≥300 cells/mcL in DRI12544 and QUEST are shown in Table 23.

Response rates by baseline blood eosinophils and baseline FeNO for QUEST are shown for the overall population in Figure 4 and Figure 5, respectively. Elevation of FeNO can be a marker of the eosinophilic asthma phenotype when supported by clinical data. Pre-specified subgroup analyses of DRI12544 and QUEST demonstrated that there were greater reductions in severe exacerbations in subjects with higher baseline blood eosinophil levels (≥150 cells/mcL) or FeNO (≥25 ppb). In QUEST, reductions in exacerbations were significant in the subgroup of subjects with baseline blood eosinophils ≥150 cells/mcL. In subjects with baseline blood eosinophil count <150 cells/mcL and FeNO <25 ppb, similar severe exacerbation rates were observed between DUPIXENT and placebo.

In QUEST, the estimated rate ratio of exacerbations leading to hospitalizations and/or emergency room visits versus placebo was 0.53 (95% CI: 0.28, 1.03) and 0.74 (95% CI: 0.32, 1.70) with DUPIXENT 200 mg or 300 mg Q2W, respectively.

Table 23: Rate of Severe Exacerbations in Asthma Trials (DRI12544 and QUEST)
Trial | Treatment | Baseline Blood EOS ≥300 cells/mcL (primary analysis population, DRI12544)
Trial | Treatment | N | Rate (95% CI) | Rate Ratio (95% CI)
DRI12544 | DUPIXENT 200 mg Q2W | 65 | 0.30 (0.13, 0.68) | 0.29 (0.11, 0.76)
DRI12544 | DUPIXENT 300 mg Q2W | 64 | 0.20 (0.08, 0.52) | 0.19 (0.07, 0.56)
DRI12544 | Placebo | 68 | 1.04 (0.57, 1.90)
QUEST | DUPIXENT 200 mg Q2W | 264 | 0.37 (0.29, 0.48) | 0.34 (0.24, 0.48)
QUEST | Placebo | 148 | 1.08 (0.85, 1.38)
QUEST | DUPIXENT 300 mg Q2W | 277 | 0.40 (0.32, 0.51) | 0.33 (0.23, 0.45)
QUEST | Placebo | 142 | 1.24 (0.97, 1.57)

Figure 4: Relative Risk in Annualized Event Rate of Severe Exacerbations across Baseline Blood Eosinophil Count (cells/mcL) in Subjects with Moderate-to-Severe Asthma (QUEST)

Figure 5: Relative Risk in Annualized Event Rate of Severe Exacerbations across Baseline FeNO Group (ppb) in Subjects with Moderate-to-Severe Asthma (QUEST)

The time to first exacerbation was longer for the subjects receiving DUPIXENT compared to placebo in QUEST (Figure 6).

Figure 6: Kaplan Meier Incidence Curve for Time to First Severe Exacerbation in Subjects with Moderate-to-Severe Asthma with Baseline Blood Eosinophils ≥300 cells/mcL (QUEST) [At the time of the database lock, not all subjects had completed Week 52]

Lung Function in Subjects with Asthma

Significant increases in pre-bronchodilator FEV1 were observed at Week 12 for DRI12544 and QUEST in the primary analysis populations (subjects with baseline blood eosinophil count of ≥300 cells/mcL in DRI12544 and the overall population in QUEST). In the overall population in QUEST, the FEV1 LS mean change from baseline was 0.32 L (21%) and 0.34 L (23%) for DUPIXENT 200 mg Q2W and 300 mg Q2W, respectively, compared to matched placebo means of 0.18 L (12%) and 0.21 L (14%). The mean treatment difference versus placebo was 0.14 L (95% CI: 0.08, 0.19) and 0.13 L (95% CI: 0.08, 0.18) for DUPIXENT 200 mg Q2W and 300 mg Q2W, respectively. Results in subjects with baseline blood eosinophil counts ≥300 cells/mcL in DRI12544 and QUEST are shown in Table 24.

Improvements in FEV1 by baseline blood eosinophils and baseline FeNO for QUEST are shown in Figure 7 and 8, respectively. Subgroup analysis of DRI12544 and QUEST demonstrated greater improvement in subjects with higher baseline blood eosinophils (≥150 cells/mcL) or FeNO (≥25 ppb). In subjects with baseline blood eosinophil count <150 cells/mcL and FeNO <25 ppb, similar differences in FEV1 were observed between DUPIXENT and placebo.

Mean changes in FEV1 over time in QUEST are shown in Figure 9.

Table 24: Mean Change from Baseline and Difference vs Placebo in Pre-Bronchodilator FEV1 at Week 12 in Subjects with Moderate-to-Severe Asthma (DRI12544 and QUEST)
Trial | Treatment | Baseline Blood EOS ≥300 cells/mcL (primary analysis population, DRI12544)
Trial | Treatment | N | LS Mean Change from baseline L (%) | LS Mean Difference vs. placebo (95% CI)
DRI12544 | DUPIXENT 200 mg Q2W | 65 | 0.43 (25.9) | 0.26 (0.11, 0.40)
DRI12544 | DUPIXENT 300 mg Q2W | 64 | 0.39 (25.8) | 0.21 (0.06, 0.36)
DRI12544 | Placebo | 68 | 0.18 (10.2)
QUEST | DUPIXENT 200 mg Q2W | 264 | 0.43 (29.0) | 0.21 (0.13, 0.29)
QUEST | Placebo | 148 | 0.21 (15.6)
QUEST | DUPIXENT 300 mg Q2W | 277 | 0.47 (32.5) | 0.24 (0.16, 0.32)
QUEST | Placebo | 142 | 0.22 (14.4)

Figure 7: LS Mean Difference in Change from Baseline vs Placebo to Week 12 in Pre-Bronchodilator FEV1 across Baseline Blood Eosinophil Counts (cells/mcL) in Subjects with Moderate-to-Severe Asthma (QUEST)

Figure 8: LS Mean Difference in Change from Baseline vs Placebo to Week 12 in Pre-bronchodilator FEV1 across Baseline FeNO (ppb) in Subjects with Moderate-to-Severe Asthma (QUEST)

Figure 9: Mean Change from Baseline in Pre-Bronchodilator FEV1 (L) Over Time in Subjects with Moderate-to-Severe Asthma with Baseline Blood Eosinophils ≥300 cells/mcL (QUEST)

Additional Secondary Endpoints in Asthma Trial (QUEST)

ACQ-5 and AQLQ(S) were assessed in QUEST at 52 weeks. The responder rate was defined as an improvement in score of 0.5 or more (scale range 0-6 for ACQ-5 and 1-7 for AQLQ(S)).

- The ACQ-5 responder rate for DUPIXENT 200 mg and 300 mg Q2W in the overall population was 69% vs 62% placebo (odds ratio 1.37; 95% CI: 1.01, 1.86) and 69% vs 63% placebo (odds ratio 1.28; 95% CI: 0.94, 1.73), respectively; and the AQLQ(S) responder rates were 62% vs 54% placebo (odds ratio 1.61; 95% CI: 1.17, 2.21) and 62% vs 57% placebo (odds ratio 1.33; 95% CI: 0.98, 1.81), respectively.
- The ACQ-5 responder rate for DUPIXENT 200 mg and 300 mg Q2W in subjects with baseline blood eosinophils ≥300 cells/mcL was 75% vs 67% placebo (odds ratio: 1.46; 95% CI: 0.90, 2.35) and 71% vs 64% placebo (odds ratio: 1.39; 95% CI: 0.88, 2.19), respectively; and the AQLQ(S) responder rates were 71% vs 55% placebo (odds ratio: 2.02; 95% CI: 1.24, 3.32) and 65% vs 55% placebo (odds ratio: 1.79; 95% CI: 1.13, 2.85), respectively.

Oral Corticosteroid Reduction in Asthma Trial (VENTURE)

VENTURE evaluated the effect of DUPIXENT on reducing the use of maintenance oral corticosteroids. The baseline mean oral corticosteroid dose was 12 mg in the placebo group and 11 mg in the group receiving DUPIXENT. The primary endpoint was the percent reduction from baseline of the final oral corticosteroid dose at Week 24 while maintaining asthma control.

Compared with placebo, subjects receiving DUPIXENT achieved greater reductions in daily maintenance oral corticosteroid dose, while maintaining asthma control. The mean percent reduction in daily OCS dose from baseline was 70% (median 100%) in subjects receiving DUPIXENT (95% CI: 60%, 80%) compared to 42% (median 50%) in subjects receiving placebo (95% CI: 33%, 51%). Reductions of 50% or higher in the OCS dose were observed in 82 (80%) subjects receiving DUPIXENT compared to 57 (53%) in those receiving placebo. The proportion of subjects with a mean final dose less than 5 mg at Week 24 was 72% for DUPIXENT and 37% for placebo (odds ratio 4.48 95% CI: 2.39, 8.39). A total of 54 (52%) subjects receiving DUPIXENT versus 31 (29%) subjects in the placebo group had a 100% reduction in their OCS dose.

In this 24-week trial, asthma exacerbations (defined as a temporary increase in oral corticosteroid dose for at least 3 days) were lower in subjects receiving DUPIXENT compared with those receiving placebo (annualized rate 0.65 and 1.60 for the DUPIXENT and placebo group, respectively; rate ratio 0.41 [95% CI 0.26, 0.63]) and improvement in pre-bronchodilator FEV1 from baseline to Week 24 was greater in subjects receiving DUPIXENT compared with those receiving placebo (LS mean difference for DUPIXENT versus placebo of 0.22 L [95% CI: 0.09 to 0.34 L]). Effects on lung function and on oral steroid and exacerbation reduction were similar irrespective of baseline blood eosinophil levels. The ACQ-5 and AQLQ(S) were also assessed in VENTURE and showed improvements similar to those in QUEST.

Pediatric Subjects 6 to 11 Years of Age with Asthma

The efficacy and safety of DUPIXENT in pediatric subjects was evaluated in a 52-week multicenter, randomized, double-blind, placebo-controlled study (VOYAGE; NCT02948959) in 408 subjects 6 to 11 years of age, with moderate-to-severe asthma on a medium or high-dose ICS and a second controller medication or high-dose ICS alone. Subjects were required to have a history of 1 or more asthma exacerbation(s) that required treatment with systemic corticosteroids or emergency department visit or hospitalization for the treatment of asthma in the year prior to trial entry. Subjects were randomized to DUPIXENT (N=273) or matching placebo (N=135) every 2 weeks based on body weight <30 kg (100 mg Q2W) or ≥30 kg (200 mg Q2W). The effectiveness of DUPIXENT 300 mg Q4W was extrapolated from efficacy of 100 mg Q2W in VOYAGE with support from population pharmacokinetic analyses showing higher drug exposure levels with 300 mg Q4W [see Pediatric Use (8.4) and Pharmacokinetics (12.3)].

The primary endpoint was the annualized rate of severe asthma exacerbation events during the 52-week placebo-controlled period. Severe asthma exacerbations were defined as deterioration of asthma requiring the use of systemic corticosteroids for at least 3 days or hospitalization or emergency room visit due to asthma that required systemic corticosteroids. The key secondary endpoint was the change from baseline in pre-bronchodilator FEV1 percent predicted at Week 12. Additional secondary endpoints included mean change from baseline and responder rates in the ACQ-7-IA (Asthma Control Questionnaire-7-Interviewer Administered) and PAQLQ(S)-IA (Pediatric Asthma Quality of Life Questionnaire with Standardized Activities Interviewer Administered) scores.

The demographics and baseline characteristics for VOYAGE are provided in Table 25 below.

Table 25: Demographics and Baseline Characteristics of Pediatric Subjects 6 to 11 Years of Age with Asthma (VOYAGE)
Parameter | VOYAGE (N=408)
Mean age (years) (SD) | 9 (2)
% Female | 36
% White | 88
Mean body weight (kg) | 36
Mean exacerbations in previous year (± SD) | 2.4 (2.2)
High dose ICS use (%) | 44
Pre-dose FEV1 (L) at baseline (± SD) | 1.48 (0.41)
Mean percent predicted FEV1 (%) (±SD) | 78 (15)
Mean % Reversibility (± SD) | 20 (21)
Atopic Medical History % Overall (AD %, AR %) | 92 (36, 82)
Mean FeNO ppb (± SD) | 28 (24)
% subjects with FeNO ppb ≥20 | 50
Median total IgE IU/mL (±SD) | 792 (1093)
Mean baseline Eosinophil count (± SD) cells/mcL | 502 (395)
ICS = inhaled corticosteroid; FEV1 = Forced expiratory volume in 1 second; AD = atopic dermatitis; AR = allergic rhinitis; FeNO = fraction of exhaled nitric oxide

DUPIXENT significantly reduced the annualized rate of severe asthma exacerbation events during the 52-week treatment period compared to placebo in populations with an eosinophilic phenotype as indicated by elevated blood eosinophils and/or the population with elevated FeNO. Subgroup analyses for results of DUPIXENT treatment based upon either baseline eosinophil level or baseline FeNO level were similar to the pediatric (12 to 17 years of age) and adult trials and are described for the adult and pediatric (12 to 17 years of age) asthma population above. In subjects with baseline blood eosinophil count <150 cells/mcL and FeNO <20 ppb, similar severe asthma exacerbation rates were observed between DUPIXENT and placebo.

Significant improvements in percent predicted pre-bronchodilator FEV1 were observed at Week 12. Significant improvements in percent predicted FEV1 were observed as early as Week 2 and were maintained through Week 52 in VOYAGE (Figure 10).

The efficacy results for VOYAGE are presented in Table 26.

Table 26: Efficacy Results of DUPIXENT in Pediatric Subjects 6 to 11 Years of Age with Asthma (VOYAGE)
Treatment | EOS ≥300 cells/mcL [This reflects the prespecified primary analysis population for VOYAGE in the United States.]
Annualized Severe Exacerbations Rate over 52 Weeks
 | N | Rate (95% CI) | Rate Ratio (95% CI)
DUPIXENT 100 mg Q2W [The effectiveness of DUPIXENT 300 mg Q4W was extrapolated from efficacy of 100 mg Q2W.] (<30 kg)/ 200 mg Q2W (≥30 kg) | 175 | 0.24 (0.16, 0.35) | 0.35 (0.22, 0.56)
Placebo | 84 | 0.67 (0.47, 0.95)
Mean Change from Baseline in Percent Predicted FEV1 at Week 12
 | N | LS mean Δ from Baseline | LS mean difference vs. Placebo (95% CI)
DUPIXENT 100 mg Q2W (<30 kg)/ 200 mg Q2W (≥30 kg) | 168 | 10.15 | 5.32 (1.76, 8.88)
Placebo | 80 | 4.83

Figure 10: Mean Change from Baseline in Percent Predicted Pre-bronchodilator FEV1 (L) Over Time in Pediatric Subjects 6 to 11 Years of Age in VOYAGE (Baseline Blood Eosinophils ≥300 cells/mcL)

Improvements were also observed for ACQ-7-IA and PAQLQ(S)-IA at Week 24 and were sustained at Week 52. Greater responder rates were observed for ACQ-7-IA and PAQLQ(S)-IA compared to placebo at Week 24. The responder rate was defined as an improvement in score of 0.5 or more (scale range 0-6 for ACQ-7-IA and 1-7 for PAQLQ(S)-IA). In the subgroup of subjects with baseline blood eosinophil count ≥300 cells/mcL, DUPIXENT led to a higher proportion of subjects with a response in ACQ-7-IA (80.6% versus 64.3% for placebo) with an OR of 2.79 (95% CI: 1.43, 5.44), and in PAQLQ(S)-IA (72.8% versus 63.0% for placebo) with an OR of 1.84 (95% CI: 0.92, 3.65) at Week 24.

14.3 Chronic Rhinosinusitis with Nasal Polyps

The efficacy of DUPIXENT as an add-on maintenance treatment in adults with inadequately controlled chronic rhinosinusitis with nasal polyps (CRSwNP) was evaluated in two randomized, double-blind, parallel-group, multicenter, placebo-controlled studies (SINUS-24 (NCT02912468) and SINUS-52 (NCT02898454)) in 724 adult subjects 18 years of age and older on background intranasal corticosteroids (INCS). These studies included subjects with CRSwNP despite prior sino-nasal surgery or treatment with, or who were ineligible to receive or were intolerant to, systemic corticosteroids in the past 2 years. Subjects with chronic rhinosinusitis without nasal polyps were not included in these trials. Rescue with systemic corticosteroids or surgery was allowed during the studies at the investigator's discretion. In SINUS-24, a total of 276 subjects were randomized to receive either 300 mg DUPIXENT (N=143) or placebo (N=133) every 2 weeks for 24 weeks. In SINUS-52, 448 subjects were randomized to receive either 300 mg DUPIXENT (N=150) every 2 weeks for 52 weeks, 300 mg DUPIXENT (N=145) every 2 weeks until Week 24 followed by 300 mg DUPIXENT every 4 weeks until Week 52, or placebo (N=153). All subjects had evidence of sinus opacification on the Lund Mackay (LMK) sinus CT scan and 73% to 90% of subjects had opacification of all sinuses. Subjects were stratified based on their histories of prior surgery and co-morbid asthma/nonsteroidal anti-inflammatory drug exacerbated respiratory disease (NSAID-ERD). A total of 63% of subjects reported previous sinus surgery, with a mean number of 2.0 prior surgeries, 74% used systemic corticosteroids in the previous 2 years with a mean number of 1.6 systemic corticosteroid courses in the previous 2 years, 59% had co-morbid asthma, and 28% had NSAID-ERD.

The co-primary efficacy endpoints were change from baseline to Week 24 in bilateral endoscopic nasal polyps score (NPS; 0-8 scale) as graded by central blinded readers, and change from baseline to Week 24 in nasal congestion/obstruction score averaged over 28 days (NC; 0-3 scale), as determined by subjects using a daily diary. For NPS, polyps on each side of the nose were graded on a categorical scale (0=no polyps; 1=small polyps in the middle meatus not reaching below the inferior border of the middle turbinate; 2=polyps reaching below the lower border of the middle turbinate; 3=large polyps reaching the lower border of the inferior turbinate or polyps medial to the middle turbinate; 4=large polyps causing complete obstruction of the inferior nasal cavity). The total score was the sum of the right and left scores. Nasal congestion was rated daily by the subjects on a 0 to 3 categorical severity scale (0=no symptoms; 1=mild symptoms; 2=moderate symptoms; 3=severe symptoms).

In both studies, key secondary end-points at Week 24 included change from baseline in: LMK sinus CT scan score, daily loss of smell, and 22-item sino-nasal outcome test (SNOT-22). The LMK sinus CT scan score evaluated the opacification of each sinus using a 0 to 2 scale (0=normal; 1=partial opacification; 2=total opacification) deriving a maximum score of 12 per side and a total maximum score of 24 (higher scores indicate more opacification). Loss of smell was scored reflectively by the subject every morning on a 0-3 scale (0=no symptoms, 1=mild symptoms, 2=moderate symptoms, 3=severe symptoms). SNOT-22 includes 22 items assessing symptoms and symptom impact associated with CRSwNP with each item scored from 0 (no problem) to 5 (problem as bad as it can be) with a global score ranging from 0 to 110. SNOT-22 had a 2 week recall period. In the pooled efficacy results, the reduction in the proportion of subjects rescued with systemic corticosteroids and/or sino-nasal surgery (up to Week 52) were evaluated.

The demographics and baseline characteristics of these 2 trials are provided in Table 27 below.

Table 27: Demographics and Baseline Characteristics of Adult Subjects in CRSwNP Trials
Parameter | SINUS-24 (N=276) | SINUS-52 (N=448)
Mean age (years) (SD) | 50 (13) | 52 (12)
% Male | 57 | 62
Mean CRSwNP duration (years) (SD) | 11 (9) | 11 (10)
Subjects with ≥1 prior surgery (%) | 72 | 58
Subjects with systemic corticosteroid use in the previous 2 years (%) | 65 | 80
Mean Bilateral endoscopic NPS [Higher scores indicate greater disease severity] (SD), range 0-8 | 5.8 (1.3) | 6.1 (1.2)
Mean Nasal congestion (NC) score (SD), range 0-3 | 2.4 (0.6) | 2.4 (0.6)
Mean LMK sinus CT total score (SD), range 0-24 | 19 (4.4) | 18 (3.8)
Mean loss of smell score (AM), (SD) range 0-3 | 2.7 (0.5) | 2.8 (0.5)
Mean SNOT-22 total score (SD), range 0-110 | 49.4 (20.2) | 51.9 (20.9)
Mean blood eosinophils (cells/mcL) (SD) | 440 (330) | 430 (350)
Mean total IgE IU/mL (SD) | 212 (276) | 240 (342)
Atopic Medical History % Overall | 75 | 82
Asthma (%) | 58 | 60
NSAID-ERD (%) | 30 | 27
SD = standard deviation; AM = morning; NPS = nasal polyps score; SNOT-22 = 22-item sino-nasal outcome test; NSAID-ERD = asthma/nonsteroidal anti-inflammatory drug exacerbated respiratory disease

Clinical Response (SINUS-24 and SINUS-52)

The results for primary endpoints in CRSwNP studies are presented in Table 28.

Table 28: Results of the Primary Endpoints in CRSwNP Trials
 | SINUS-24 |  |  |  |  | SINUS-52
 | Placebo (n=133) |  | DUPIXENT 300 mg Q2W (n=143) |  | LS mean difference vs. Placebo (95% CI) | Placebo (n=153) |  | DUPIXENT 300 mg Q2W (n=295) |  | LS mean difference vs. Placebo (95% CI)
Primary Endpoints at Week 24
Scores | Baseline mean | LS mean change | Baseline mean | LS mean change |  | Baseline mean | LS mean change | Baseline mean | LS mean change
NPS | 5.86 | 0.17 | 5.64 | -1.89 | -2.06 (-2.43, -1.69) | 5.96 | 0.10 | 6.18 | -1.71 | -1.80 (-2.10, -1.51)
NC | 2.45 | -0.45 | 2.26 | -1.34 | -0.89 (-1.07, -0.71) | 2.38 | -0.38 | 2.46 | -1.25 | -0.87 (-1.03, -0.71)
A reduction in score indicates improvement.
NPS = nasal polyps score; NC = nasal congestion/obstruction

Statistically significant efficacy was observed in SINUS-52 with regard to improvement in bilateral endoscopic NPS score at week 24 and week 52 (see Figure 11).

Figure 11: LS Mean Change from Baseline in Bilateral Nasal Polyps Score (NPS) up to Week 52 in Subjects 18 Years of Age and Older with CRSwNP (SINUS-52 - ITT Population)

Similar results were seen in SINUS-24 at Week 24. In the post-treatment period when subjects were off DUPIXENT, the treatment effect diminished over time (see Figure 12).

Figure 12: LS Mean Change from Baseline in Bilateral Nasal Polyps Score (NPS) up to Week 48 in Subjects 18 Years of Age and Older with CRSwNP (SINUS-24 - ITT Population)

At Week 52, the LS mean difference for nasal congestion in the DUPIXENT group versus placebo was -0.98 (95% CI -1.17, -0.79). In both studies, significant improvements in nasal congestion were observed as early as the first assessment at Week 4. The LS mean difference for nasal congestion at Week 4 in the DUPIXENT group versus placebo was -0.41 (95% CI: -0.52, -0.30) in SINUS-24 and -0.37 (95% CI: -0.46, -0.27) in SINUS-52.

A significant decrease in the LMK sinus CT scan score was observed. The LS mean difference for LMK sinus CT scan score at Week 24 in the DUPIXENT group versus placebo was -7.44 (95% CI: -8.35, -6.53) in SINUS-24 and -5.13 (95% CI: -5.80, -4.46) in SINUS-52. At Week 52, in SINUS-52 the LS mean difference for LMK sinus CT scan score in the DUPIXENT group versus placebo was -6.94 (95% CI: -7.87, -6.01).

Dupilumab significantly improved the loss of smell compared to placebo. The LS mean difference for loss of smell at Week 24 in the DUPIXENT group versus placebo was -1.12 (95% CI: -1.31, -0.93) in SINUS-24 and -0.98 (95% CI: -1.15, -0.81) in SINUS-52. At Week 52, the LS mean difference for loss of smell in the DUPIXENT group versus placebo was -1.10 (95% CI -1.31, -0.89). In both studies, significant improvements in daily loss of smell severity were observed as early as the first assessment at Week 4.

Dupilumab significantly decreased sino-nasal symptoms as measured by SNOT-22 compared to placebo. The LS mean difference for SNOT-22 at Week 24 in the DUPIXENT group versus placebo was -21.12 (95% CI: -25.17, -17.06) in SINUS-24 and -17.36 (95% CI: -20.87, -13.85) in SINUS-52. At Week 52, the LS mean difference in the DUPIXENT group versus placebo was -20.96 (95% CI -25.03, -16.89).

In the pre-specified multiplicity-adjusted pooled analysis of two studies, treatment with DUPIXENT resulted in significant reduction of systemic corticosteroid use and need for sino-nasal surgery versus placebo (HR of 0.24; 95% CI: 0.17, 0.35) (see Figure 13). The proportion of subjects who required systemic corticosteroids was reduced by 74% (HR of 0.26; 95% CI: 0.18, 0.38). The total number of systemic corticosteroid courses per year was reduced by 75% (RR of 0.25; 95% CI: 0.17, 0.37). The proportion of subjects who required surgery was reduced by 83% (HR of 0.17; 95% CI: 0.07, 0.46).

Figure 13: Kaplan Meier Curve for Time to First Systemic Corticosteroid Use and/or Sino-Nasal Surgery During Treatment Period in Subjects 18 Years of Age and Older with CRSwNP (SINUS-24 and SINUS-52 Pooled - ITT Population)

The effects of DUPIXENT on the primary endpoints of NPS and nasal congestion and the key secondary endpoint of LMK sinus CT scan score were consistent in subjects with prior surgery and without prior surgery.

In subjects with co-morbid asthma, improvements in pre-bronchodilator FEV1 were similar to subjects in the asthma program.

14.4 Eosinophilic Esophagitis

Adult and Pediatric Subjects 12 Years of Age and Older with EoE

A single randomized, double-blind, parallel-group, multicenter, placebo-controlled trial, including two 24-week treatment periods (Study EoE-1 Parts A and B) was conducted in adult and pediatric subjects 12 years of age and older, weighing at least 40 kg, with EoE (NCT03633617). In both parts, subjects were randomized to receive 300 mg DUPIXENT every week or placebo. Eligible subjects had ≥15 intraepithelial eosinophils per high-power field (eos/hpf) following a treatment course of a proton pump inhibitor (PPI) either prior to or during the screening period and symptoms of dysphagia as measured by the Dysphagia Symptom Questionnaire (DSQ). At baseline, 43% of subjects in Part A and 37% of subjects in Part B had a history of prior esophageal dilations.

Demographics and baseline characteristics were similar in Parts A and B. A total of 81 subjects (61 adults and 20 pediatric subjects) were enrolled in Part A and 159 subjects (107 adults and 52 pediatric subjects) were enrolled in Part B. The mean age in years was 32 years (range 13 to 62 years) in Part A and 28 years (range 12 to 66 years) in Part B. The majority of subjects were male (60% in Part A and 68% in Part B) and White (96% in Part A and 90% in Part B). The mean baseline DSQ score (SD) was 33.6 (12.4) in Part A and 37.2 (10.7) in Part B.

The coprimary efficacy endpoints in Parts A and B were the (1) proportion of subjects achieving histological remission defined as peak esophageal intraepithelial eosinophil count of ≤6 eos/hpf at Week 24; and (2) the absolute change in the subject-reported DSQ score from baseline to Week 24.

Efficacy results for Parts A and B are presented in Table 29.

Table 29: Efficacy Results of DUPIXENT at Week 24 in Adult and Pediatric Subjects 12 Years of Age and Older with EoE (Study EoE-1 Parts A and B)
 | Study EoE-1 Part A |  |  | Study EoE-1 Part B
 | DUPIXENT 300 mg QW [For histological remission, the difference in percentages is estimated using the Cochran Mantel Haenszel method, adjusting for randomization stratification factors. For absolute change in DSQ score, the LS mean changes, standard errors, and differences are estimated using an ANCOVA model with treatment group, randomization stratification factors, and baseline measurement as covariates.] | Placebo | Difference vs. Placebo (95% CI) | DUPIXENT 300 mg QW | Placebo | Difference vs. Placebo (95% CI)
 | N = 42 | N = 39 |  | N = 80 | N = 79
Co-primary Endpoints
Proportion of subjects achieving histological remission (peak esophageal intraepithelial eosinophil count ≤6 eos/hpf), n (%) | 25 (59.5) | 2 (5.1) | 57.0 (40.9, 73.1) | 47 (58.8) | 5 (6.3) | 53.5 (41.2, 65.8)
Absolute change from baseline in DSQ score (0-84 [Total biweekly DSQ scores range from 0 to 84; higher scores indicate greater frequency and severity of dysphagia]), LS mean (SE) | -21.9 (2.5) | -9.6 (2.8) | -12.3 (-19.1, -5.5) | -23.8 (1.9) | -13.9 (1.9) | -9.9 (-14.8, -5.0)

In Parts A and B, a greater proportion of subjects randomized to DUPIXENT achieved histological remission (peak esophageal intraepithelial eosinophil count ≤6 eos/hpf) compared to placebo. Treatment with DUPIXENT also resulted in a significant improvement in LS mean change in DSQ score compared to placebo at Week 24. The results of the anchor-based analyses that incorporated the subjects' perspectives indicated that the observed improvement in dysphagia from Parts A and B is representative of a clinically meaningful within-subject improvement.

Pediatric Subjects 1 to 11 Years of Age, Weighing at Least 15 kg, with EoE

The efficacy and safety of DUPIXENT was evaluated in pediatric subjects 1 to 11 years of age, weighing at least 15 kg, with EoE in a randomized, blinded, parallel-group, multicenter trial (Study EoE-2 Parts A and B; NCT04394351). Eligible subjects had ≥15 intraepithelial eosinophils per high-power field (eos/hpf) despite a treatment course of a proton pump inhibitor (PPI) either prior to or during the screening period and a history of EoE signs and symptoms. Part A evaluated weight-based dosing regimens of DUPIXENT, 200 mg Q2W (≥15 to <30 kg) and 300 mg Q2W (≥30 to <60 kg), or placebo in 61 subjects during the 16-week treatment period.

The recommended dosage of 300 mg QW for pediatric subjects 1 to 11 years of age weighing ≥40 kg is based on modeled pharmacokinetic data to provide comparable exposures to the 300 mg QW dosage in adult and pediatric subjects 12 years of age and older weighing ≥40 kg with EoE [see Dosage and Administration (2.6) and Pharmacokinetics (12.3)].

Forty-seven subjects who completed Part A were evaluated in the 36-week extended active treatment period (Study EoE-2 Part B). All subjects in Part B were treated with the weight-based dosing regimens of DUPIXENT described for Part A.

Of the total subjects evaluated in Part A, the mean age was 8 years, the median weight was 28 kg, and 75% were male. Seven percent identified as Hispanic or Latino; 85% identified as White, 12% as Black, 2% as Asian, and 2% identified as another racial subgroup.

The primary efficacy endpoint in Part A was the proportion of subjects achieving histological remission defined as peak esophageal intraepithelial eosinophil count of ≤6 eos/hpf at Week 16.

Efficacy results for Part A are presented in Table 30.

Table 30: Efficacy Results of DUPIXENT at Week 16 in Subjects 1 to 11 Years of Age with EoE, Weighing at Least 15 kg (Study EoE-2 Part A)
 | DUPIXENT [DUPIXENT was evaluated at tiered dosing regimens based on body weight: ≥15 to <30 kg (200 mg Q2W) and ≥30 to <60 kg (300 mg Q2W). The 300 mg Q2W dosing regimen is lower than the recommended dosage of DUPIXENT in subjects ≥40 kg [see Dosage and Administration (2.6)].] N=32 | Placebo N=29 | Difference vs Placebo (95% CI)
Proportion of subjects achieving histological remission (peak esophageal intraepithelial eosinophil count ≤6 eos/hpf), n (%) [The difference in percentages is estimated using the Mantel-Haenszel method, adjusting for baseline weight group (≥15 to <30 kg and ≥30 to <60 kg).] | 21 (65.6) | 1 (3.4) | 62.0 (44.00, 79.95)

In Part B, histological remission was achieved at Week 52 in 17/32 subjects treated with DUPIXENT in Parts A and B and 8/15 subjects treated with placebo in Part A and DUPIXENT in Part B.

In Study EoE-2 Part A, an observer-reported outcome, the Pediatric EoE Sign/Symptom Questionnaire-Caregiver (PESQ-C), was used to measure signs of EoE. A greater decrease in the proportion of days with 1 or more signs of EoE (based on the PESQ-C) was observed for subjects treated with DUPIXENT compared to placebo after 16 weeks of treatment.

14.5 Prurigo Nodularis

The efficacy of DUPIXENT in adults with prurigo nodularis (PN) was evaluated in two 24-week randomized, double-blind, placebo-controlled, multicenter, parallel-group trials (PRIME (NCT04183335) and PRIME 2 (NCT04202679)). These trials enrolled 311 adult subjects with pruritus (WI-NRS ≥ 7 on a scale of 0 to 10) and greater than or equal to 20 nodular lesions. PRIME and PRIME 2 assessed the effect of DUPIXENT on pruritus improvement as well as its effect on PN lesions.

In these two trials, subjects received either subcutaneous DUPIXENT 600 mg (two 300 mg injections) on day 1, followed by 300 mg once every 2 weeks (Q2W) for 24 weeks, or matching placebo.

In these trials, the mean age was 49.5 years, the median weight was 71 kg, 65% of subjects were female, 57% were White, 6% were Black, and 34% were Asian. At baseline, the mean Worst Itch-Numeric Rating Scale (WI-NRS) was 8.5, 66% had 20 to 100 nodules (moderate), and 34% had greater than 100 nodules (severe). Eleven percent (11%) of subjects were taking stable doses of antidepressants at baseline and were instructed to continue taking these medications during the trial. Forty-three percent (43%) had a history of atopy (defined as having a medical history of AD, allergic rhinitis/rhinoconjunctivitis, asthma, or food allergy).

The WI-NRS is comprised of a single item, rated on a scale from 0 ("no itch") to 10 ("worst imaginable itch"). Subjects were asked to rate the intensity of their worst pruritus (itch) over the past 24 hours using this scale. The Investigator's Global Assessment for Prurigo Nodularis-Stage (IGA PN-S) is a scale that measures the approximate number of nodules using a 5-point scale from 0 (clear) to 4 (severe).

Efficacy was assessed with the proportion of subjects with improvement (reduction) in WI-NRS by ≥4 points, the proportion of subjects with IGA PN-S 0 or 1 (the equivalent of 0-5 nodules), and the proportion of subjects who achieved a response in both WI-NRS and IGA PN-S per the criteria described above.

The efficacy results for PRIME and PRIME2 are presented in Table 31 and Figures 14, 15, and 16.

Table 31: Efficacy Results of DUPIXENT in Adult Subjects with PN in PRIME and PRIME2
 | PRIME |  |  | PRIME2
 | Placebo (N=76) | DUPIXENT 300 mg Q2W (N=75) | Difference (95% CI) for DUPIXENT vs. Placebo | Placebo (N=82) | DUPIXENT 300 mg Q2W (N=78) | Difference (95% CI) for DUPIXENT vs. Placebo
Proportion of subjects with both an improvement (reduction) in WI-NRS by ≥4 points from baseline to Week 24 and an IGA PN-S 0 or 1 at Week 24 [Subjects who received rescue treatment earlier or had missing data were considered as non-responders.] | 9.2% | 38.7% | 29.6% (16.4, 42.8) | 8.5% | 32.1% | 25.5% (13.1, 37.9)
Proportion of subjects with improvement (reduction) in WI-NRS by ≥4 points from baseline at Week 24 | 18.4% | 60.0% | 42.7% (27.8, 57.7) | 19.5% | 57.7% | 42.6% (29.1, 56.1)
Proportion of subjects with IGA PN-S 0 or 1 at Week 24 | 18.4% | 48.0% | 28.3% (13.4, 43.2) | 15.9% | 44.9% | 30.8% (16.4, 45.2)
Proportion of subjects with improvement (reduction) in WI-NRS by ≥4 points from baseline at Week 12 | 15.8% [Not adjusted for multiplicity in PRIME.] | 44.0% | 29.2% (14.5, 43.8) | 22.0% | 37.2% | 16.8% (2.3, 31.2)

Figure 14: Proportion of Adult Subjects with PN with Both WI-NRS ≥4-point Improvement and IGA PN-S 0 or 1 Over Time in PRIME and PRIME2

Figure 15: Proportion of Adult Subjects with PN with WI-NRS ≥4-point Improvement Over Time in PRIME and PRIME2

Figure 16: Proportion of Adult Subjects with IGA PN-S 0 or 1 Over Time in PRIME and PRIME 2

The efficacy data did not show differential treatment effect across demographic subgroups.

14.6 Chronic Obstructive Pulmonary Disease

The efficacy of DUPIXENT as add-on maintenance treatment of adult patients with inadequately controlled COPD and an eosinophilic phenotype was evaluated in two randomized, double-blind, multicenter, parallel-group, placebo-controlled trials (BOREAS [NCT03930732] and NOTUS [NCT04456673]) of 52 weeks duration. The two trials enrolled a total of 1874 adult subjects with COPD.

Both trials enrolled subjects with a diagnosis of COPD with moderate to severe airflow limitation (post-bronchodilator FEV1/FVC ratio <0.7 and post-bronchodilator FEV1 of 30% to 70% predicted) and a minimum blood eosinophil count of 300 cells/mcL at screening. Trial enrollment required an exacerbation history of at least 2 moderate or 1 severe exacerbation(s) in the previous year despite receiving maintenance triple therapy consisting of a long-acting muscarinic antagonist (LAMA), long-acting beta agonist (LABA), and inhaled corticosteroid (ICS), and symptoms of chronic productive cough for at least 3 months in the past year. Greater than or equal to 95% of subjects in each trial had chronic bronchitis. Subjects also had a Medical Research Council (MRC) dyspnea score ≥2 (range 0-4). Exacerbations of COPD were defined as clinically significant worsening of COPD symptoms including increases in dyspnea, wheezing, cough, sputum volume, and/or increase in sputum purulence. Exacerbation severity was further defined as moderate if treatment with systemic corticosteroids and/or antibiotics was required, or severe if they resulted in hospitalization or observation for over 24 hours in an emergency department or urgent care facility.

In both trials, subjects were randomized to receive DUPIXENT 300 mg subcutaneously every 2 weeks (Q2W) or placebo in addition to their background maintenance therapy for 52 weeks.

The demographics and baseline characteristics of BOREAS and NOTUS trial populations are provided in Table 32 below.

Table 32: Demographics and Baseline Characteristics of Adult Subjects with COPD for BOREAS and NOTUS Trial Populations
Parameter | BOREAS (N = 939) | NOTUS (N = 935)
Mean age (years) (± SD) | 65.1 (8.1) | 65.0 (8.3)
Male (%) | 66.0 | 67.6
White, N (%) | 790 (84.1) | 838 (89.6)
Asian, N (%) | 134 (14.3) | 10 (1.1)
Black, N (%) | 5 (0.5) | 12 (1.3)
American Indian or Alaska Native, N (%) | 7 (0.7) | 48 (5.1)
Other/Multiple, N (%) | 3 (0.3) | 27 (2.9)
Ethnicity Hispanic/Latino, N (%) | 261 (27.8) | 300 (32.1)
Mean smoking history (pack-years) (± SD) | 40.5 (23.4) | 40.3 (27.2)
Current smokers (%) | 30.0 | 29.5
Chronic Bronchitis (%) | 95.0 | 99.9
Emphysema (%) | 32.6 | 30.4
Mean number of moderate [Exacerbations treated with either systemic corticosteroids and/or antibiotics.] or severe [Exacerbations requiring hospitalization or observation for over 24 hours in an emergency department or urgent care facility.] exacerbations in previous year (± SD) | 2.3 (1.0) | 2.1 (0.9)
Background COPD medications at randomization: ICS/LAMA/LABA (%) | 97.6 | 98.8
Mean post-bronchodilator FEV1/FVC ratio (± SD) | 0.49 (0.12) | 0.50 (0.12)
Mean post-bronchodilator FEV1 (L) (± SD) | 1.40 (0.47) | 1.45 (0.49)
Mean percent predicted post-bronchodilator FEV1 (%) (± SD) | 50.6 (13.1) | 50.1 (12.6)
Mean SGRQ total score (± SD) | 48.4 (17.4) | 51.5 (17.0)
Mean screening blood eosinophil count [Reported screening eosinophil value is the highest values from up to three retests] (cells/mcL) (± SD) | 521 (307) | 538 (333)
Mean baseline blood eosinophil count [Reported baseline eosinophil value was obtained within 4 weeks of screening value] (cells/mcL) (± SD) | 401 (298) | 407 (336)
ICS = inhaled corticosteroid; LAMA = long-acting muscarinic antagonist; LABA = long-acting beta agonist;
FEV1 = forced expiratory volume in 1 second; FVC = forced vital capacity

Exacerbations in Adult Subjects with COPD

The primary endpoint for BOREAS and NOTUS trials was the annualized rate of moderate or severe COPD exacerbations during the 52-week treatment period. In both trials, DUPIXENT demonstrated a significant reduction in the annualized rate of moderate or severe COPD exacerbations compared to placebo when added to background maintenance therapy (see Table 33).

Table 33: Annualized Rate of Moderate [Exacerbations treated with either systemic corticosteroids and/or antibiotics.] or Severe [Exacerbations requiring hospitalization or observation for over 24 hours in an emergency department or urgent care facility or resulting in death.] COPD Exacerbations in BOREAS and NOTUS Trials
Trial | Treatment (N) | Rate (exacerbations/year) | Rate Ratio vs. Placebo (95% CI)
BOREAS | DUPIXENT 300 mg Q2W (N=468) | 0.78 | 0.71 (0.58, 0.86)
 | Placebo (N=471) | 1.10
NOTUS | DUPIXENT 300 mg Q2W (N=470) | 0.86 | 0.66 (0.54, 0.82)
 | Placebo (N=465) | 1.30

Treatment with DUPIXENT decreased the risk of a moderate to severe COPD exacerbation as measured by time to first exacerbation when compared with placebo in BOREAS (HR: 0.80; 95% CI: 0.66, 0.98) and NOTUS (HR: 0.71; 95% CI: 0.57, 0.89).

Lung Function in Adult Subjects with COPD

In both trials (BOREAS and NOTUS), DUPIXENT demonstrated numerical improvement in post-bronchodilator FEV1 at Weeks 12 and 52 compared to placebo when added to background maintenance therapy (see Table 34 and Figure 17). Significant improvements of similar magnitude were observed in change from baseline in pre-bronchodilator FEV1 at Weeks 12 and 52 in subjects treated with DUPIXENT compared to placebo across both trials.

Table 34: Mean Change from Baseline and Difference in Post-Bronchodilator FEV1 at Weeks 12 and 52 in BOREAS and NOTUS Trials for COPD
Trial | Treatment (N) | LS Mean Change from baseline mL | LS Mean Difference vs. placebo mL (95% CI)
Post-bronchodilator FEV1 at Week 12
BOREAS | DUPIXENT 300 mg Q2W (N=468) | 158 | 74 (31, 117)
BOREAS | Placebo (N=471) | 84
NOTUS | DUPIXENT 300 mg Q2W (N=470) | 134 | 68 (26, 110)
NOTUS | Placebo (N=465) | 67
Post-bronchodilator FEV1 at Week 52
BOREAS | DUPIXENT 300 mg Q2W (N=468) | 138 | 79 (34, 124)
BOREAS | Placebo (N=471) | 58
NOTUS [Efficacy results for mean change from baseline in post-bronchodilator FEV1 at Week 52 are presented for 721 out of 935 subjects who completed the 52-week treatment period or had discontinued the trial at the time of data analysis.] | DUPIXENT 300 mg Q2W (N=362) | 127 | 67 (16, 119)
NOTUS [Efficacy results for mean change from baseline in post-bronchodilator FEV1 at Week 52 are presented for 721 out of 935 subjects who completed the 52-week treatment period or had discontinued the trial at the time of data analysis.] | Placebo (N=359) | 59

Figure 17: LS Mean Change from Baseline in Post-Bronchodilator FEV1 (mL) Over Time in BOREAS and NOTUS [Efficacy results for mean change from baseline in post-bronchodilator FEV1 over time are presented for 721 out of 935 subjects who completed the 52-week treatment period or had discontinued the trial at the time of data analysis.] Trials for COPD

BOREAS

NOTUS

Health-Related Quality of Life

In both trials (BOREAS and NOTUS), the St. George's Respiratory Questionnaire (SGRQ) total score responder rate (defined as the proportion of subjects with SGRQ improvement from baseline of at least 4 points) at Week 52 was evaluated. In BOREAS, the responder rate was 51% for subjects treated with DUPIXENT versus 43% for placebo (N=939, odds ratio: 1.44; 95% CI: 1.10, 1.89). In NOTUS, the responder rate was 51% for subjects treated with DUPIXENT versus 47% for placebo (N=721, odds ratio: 1.16; 95% CI: 0.86, 1.58).

14.7 Chronic Spontaneous Urticaria

The efficacy of DUPIXENT for the treatment of adult and pediatric patients aged 12 years and older with chronic spontaneous urticaria who remain symptomatic despite H1 antihistamine treatment was evaluated in a master protocol clinical trial (CUPID [NCT04180488]) that included three 24-week, randomized, double-blind, parallel-group, multicenter, placebo-controlled trials (CUPID Study A, Study B, and Study C), followed by 12-week blinded safety follow-up periods. CUPID Study A and Study C included subjects who remained symptomatic despite H1 antihistamine treatment and were anti-IgE treatment naïve, while CUPID Study B included patients who remained symptomatic despite H1 antihistamine and anti-IgE treatments. The efficacy of DUPIXENT was based only on CUPID Study A and Study C; Study B did not meet the primary endpoint.

CUPID Study A and Study C

A total of 284 adult and pediatric patients 12 years of age and older with CSU (Itch Severity Score over 7 days (ISS7) ≥8 on a scale of 0 to 21 and Urticaria Activity Score over 7 days (UAS7) ≥16 on a scale of 0 to 42) who were symptomatic despite the use of H1 antihistamines, but who were anti-IgE treatment naïve, were enrolled in CUPID Study A and Study C. In the DUPIXENT group, adults and pediatric subjects (12 years of age and older) weighing ≥60 kg received a subcutaneous dose of DUPIXENT 600 mg on Day 1, followed by 300 mg every 2 weeks (Q2W), while pediatric subjects (12 years of age and older) weighing 30 kg to less than 60 kg received a subcutaneous dose of DUPIXENT 400 mg on Day 1, followed by 200 mg Q2W. The demographics and baseline characteristics of the efficacy population in CUPID Study A and Study C are provided in Table 35.

Table 35: Demographics and Baseline Characteristics of Subjects with CSU in CUPID Study A and Study C
 | CUPID Study A (N=136) | CUPID Study C (N=148)
Mean age (years) (SD) | 42 (15.1) | 46 (16.3)
% Female | 66 | 70
% White | 68 | 45
% Asian | 26 | 42
% Black | 2 | 1
% Hispanic or Latino | 18 | 16
Mean body weight (kg) | 77 | 74
Mean ISS7 | 16 | 15.1
Mean UAS7 | 31.4 | 28.2
Mean HSS7 | 15.4 | 13.1
% subjects with UAS7 ≥28 | 70.6 | 58.8
Median total IgE IU/ml (Q1,Q3) | 101 (40.3, 252) | 108 (37, 309)
ISS7 = Itch Severity Score over 7 days; UAS7 = Urticaria Activity Score over 7 days; HSS7 = Hives Severity Score over 7 days; H1AH = H1 antihistamine; Q1 = 1st quartile; Q3 = 3rd quartile

The primary endpoint was change from baseline in itch severity score over 7 days (ISS7) at Week 24. The ISS7 score was defined as the sum of the daily itch severity scores (ISS), from 0 to 3, recorded at the same time of the day for a 7-day period, ranging from 0 to 21.

The key secondary endpoint was change from baseline in urticaria activity score over 7 days (UAS7) at Week 24. The UAS7 (range 0 to 42) was a composite of the weekly itch severity score (ISS7, range 0 to 21) and the weekly hive count score (HSS7, range 0 to 21).

The results for primary and secondary endpoints in CUPID Study A and Study C are presented in Table 36.

Table 36: Efficacy Results in Subjects with CSU in CUPID Study A and Study C
 | CUPID Study A |  |  | CUPID Study C
 | DUPIXENT (N=68) | Placebo (N=68) | DUPIXENT vs. Placebo (95% CI) | DUPIXENT (N=73) | Placebo (N=75) | DUPIXENT vs. Placebo (95% CI)
Primary Endpoint
Change from baseline in ISS7 at Week 24 [Values presented are LS mean change from baseline (SE) for continuous variables and number and percent of responders for binary variables.] | -10.44 (0.92) | -6.02 (0.94) | -4.42 (-6.84, -2.01) [Values presented are LS mean differences.] | -8.50 (1.39) | -6.13 (1.38) | -2.37 (-4.48, -0.27)
Secondary Endpoints
Change from baseline in UAS7 at Week 24 | -20.99 (1.77) | -11.95 (1.81) | -9.04 (-13.68, -4.40) | -15.61 (2.62) | -11.27 (2.61) | -4.34 (-8.31, -0.36)
Change from baseline in HSS7 at Week 24 | -10.54 (0.91) | -5.85 (0.93) | -4.69 (-7.08, -2.30) | -7.16 (1.30) | -5.15 (1.29) | -2.01 (-3.98, -0.04)
Proportion of patients with UAS7 ≤6 at Week 24 | 32 (47.1) | 16 (23.5) | 3.23 (1.43, 7.27) [Values presented are odds ratios.] | 29 (39.7) | 17 (22.7) | 3.05 (1.32, 7.02)
Proportion of patients with UAS7 = 0 at Week 24 | 22 (32.4) | 9 (13.2) | 3.09 (1.24, 7.69) | 22 (30.1) | 13 (17.3) | 2.73 (1.15, 6.50)

CUPID Study A showed significant improvement in ISS7 and UAS7 from baseline at Week 12 in the DUPIXENT group (LS mean difference DUPIXENT versus placebo of -2.53 [95% CI: (-4.79, -0.27)] for ISS7 and -5.44 [95% CI: (-9.77, -1.11)] for UAS7). The proportion of patients with UAS7 ≤6 at Week 12 in CUPID Study A was 35.3% in the DUPIXENT group and 17.6% in the placebo group (Odds Ratio: 2.79 [95% CI: (1.22, 6.40)]).

Mean changes in ISS7 over time in CUPID Study A and Study C are shown in Figure 18.

Figure 18: LS Mean Change from Baseline in ISS7 Over 24 Weeks in CUPID Study A and Study C

Study A

Study C

Similar changes in UAS7 and HSS7 were observed over 24 weeks.

Improvements in ISS7 and UAS7 at Week 24 were consistent regardless of the patients' baseline IgE level.

CUPID Study B

CUPID Study B enrolled 108 adult and pediatric patients 12 years of age and older with CSU who were inadequate responders (N=104) to H1 antihistamines and anti-IgE treatments or intolerant (N=4) to anti-IgE therapy. At baseline, the mean ISS7 was 16, mean UAS7 score was 31.5 and the mean HSS7 was 15.4. The majority of participants (69.4%) had a UAS7 score of ≥28 at baseline. The median (Q1, Q3) total IgE (IU/mL) at baseline was 77 (20, 204.5). CUPID Study B evaluated efficacy using the same primary and secondary endpoints as CUPID Study A and Study C. The DUPIXENT group in CUPID Study B did not meet statistical significance for reduction in the primary endpoint ISS7 at Week 24.

14.8 Bullous Pemphigoid

The efficacy of DUPIXENT in adults with bullous pemphigoid (BP) was evaluated in a 52-week randomized, double-blind, parallel-group, multicenter, placebo-controlled trial (ADEPT; NCT04206553). This trial enrolled 106 adult subjects with a Bullous Pemphigoid Disease Area Index (BPDAI) activity score ≥24 on a scale of 0-360 and a weekly average Peak Pruritus NRS score ≥4 on a scale of 0-10.

In this trial, subjects were randomized to receive either subcutaneous DUPIXENT 600 mg (two 300 mg injections) on Day 1, followed by 300 mg every other week (Q2W), or matching placebo for 52 weeks. All subjects were also initiated on a standard regimen of oral corticosteroids (prednisone or prednisolone; 0.5 or 0.75 mg/kg/day) on Day 1. After achieving control of disease activity for 2 weeks, oral corticosteroids (OCS) were tapered with the objective to taper them off no later than Week 16 as long as the control of disease activity was maintained. Subjects who experienced a loss of control of disease activity (new lesions form and existing lesions cease to heal) during OCS taper, or who relapsed post-taper, or who used rescue medications were considered treatment failures. During the OCS taper, subjects were permitted to increase their OCS once, with any subsequent increases being considered rescue therapy. Subjects could be rescued during the trial with topical or oral corticosteroids, non-steroidal immunosuppressive medications, or immunomodulating biologics. Subjects were allowed to continue trial treatment if rescued with topical or oral corticosteroids.

Demographics and baseline characteristics were similar between the treatment arms. Of the 106 subjects enrolled, the mean age was 71.3 years; 53% were female; 68% were White, 2% were Black or African American, and 15% were Asian; 3% of subjects identified as Hispanic or Latino. At baseline, 63% of subjects had prior systemic corticosteroid use for BP. The mean Peak Pruritus NRS score was 7.5 at baseline.

The primary endpoint was the proportion of subjects achieving sustained remission at Week 36. Sustained remission was defined as the achievement of complete remission and off OCS no later than Week 16, absence of disease relapse from the time of completion of the corticosteroid taper to Week 36, and absence of rescue therapy during the 36-week double-blind treatment period. Secondary endpoints included total cumulative dose of OCS and proportion of subjects with a reduction in itch defined as at least a 4-point improvement (reduction) in the Peak Pruritus NRS.

The efficacy results for ADEPT are presented in Table 37. The proportion of subjects that received rescue therapy during the 36-week treatment period was 53% in the DUPIXENT group and 79% in the placebo group.

Table 37: Efficacy Results of DUPIXENT at Week 36 in Adults with BP in ADEPT
 | DUPIXENT 300 mg Q2W + OCS (N=53) | Placebo + OCS (N=53) | Difference (95% CI) for DUPIXENT vs. Placebo
Proportion of subjects achieving sustained remission [Sustained remission was defined as the achievement of complete remission and off OCS no later than Week 16, absence of disease relapse from the time of completion of the corticosteroid taper to Week 36, and absence of rescue therapy during the 36-week double-blind treatment period.] | 18.3% | 6.1% | 12.2% (-0.8, 26.1)
Proportion of subjects with improvement (reduction) of ≥4 points in Peak Pruritus NRS from baseline | 38.3% | 10.5% | 27.8% (11.6, 43.4)

The median (min, max) cumulative dose of OCS at Week 36 was 2.8 g (1.2, 22.7) in the DUPIXENT group compared to 4.1 g (1.5, 23.3) in the placebo group.

16 HOW SUPPLIED/STORAGE AND HANDLING

How Supplied

DUPIXENT (dupilumab) Injection is a clear to slightly opalescent, colorless to pale yellow solution, supplied in single-dose pre-filled syringes with needle shield or pre-filled pens.

The pre-filled syringe with needle shield is designed to deliver:

- 300 mg of DUPIXENT in 2 mL solution (NDC 0024-5914-00)
- 200 mg of DUPIXENT in 1.14 mL solution (NDC 0024-5918-00)

The pre-filled pen is designed to deliver:

- 300 mg of DUPIXENT in 2 mL solution (NDC 0024-5915-00)
- 200 mg of DUPIXENT in 1.14 mL solution (NDC 0024-5919-00)

DUPIXENT is available in cartons containing 2 pre-filled syringes with needle shield or 2 pre-filled pens.

Pack Size | 300 mg/2 mL (150 mg/mL) Pre-filled Syringe with Needle Shield | 200 mg/1.14 mL (175 mg/mL) Pre-filled Syringe with Needle Shield
Pack of 2 syringes | NDC 0024-5914-01 | NDC 0024-5918-01

Pack Size | 300 mg/2 mL (150 mg/mL) Pre-filled Pen | 200 mg/1.14 mL (175 mg/mL) Pre-filled Pen
Pack of 2 pens | NDC 0024-5915-02 | NDC 0024-5919-02

Storage and Handling

DUPIXENT is sterile and preservative-free. Discard any unused portion.

Store refrigerated at 2°C to 8°C (36°F to 46°F) in the original carton to protect from light.

If necessary, DUPIXENT may be kept at room temperature up to 25°C (77°F) for a maximum of 14 days. Do not store above 25°C (77°F). After removal from the refrigerator, DUPIXENT must be used within 14 days or discarded.

Do not expose DUPIXENT to heat or direct sunlight.

Do NOT freeze. Do NOT shake.

17 PATIENT COUNSELING INFORMATION

Advise the patient to read the FDA-approved patient labeling (Patient Information and Instructions for Use).

Pregnancy Registry

There is a pregnancy exposure registry that monitors pregnancy outcomes in women exposed to DUPIXENT during pregnancy. Encourage participation and advise patients about how they may enroll in the registry [see Use in Specific Populations (8.1)].

Administration Instructions

Provide proper training to patients and/or caregivers on proper subcutaneous injection technique, including aseptic technique, and the preparation and administration of DUPIXENT prior to use. Advise patients to follow sharps disposal recommendations [see Dosage and Administration (2.1) and Instructions for Use].

Hypersensitivity

Advise patients to discontinue DUPIXENT and to seek immediate medical attention if they experience any symptoms of systemic hypersensitivity reactions [see Warnings and Precautions (5.1)].

Advise patients to report signs and symptoms of AGEP to their healthcare provider [see Warnings and Precautions (5.1)].

Conjunctivitis and Keratitis

Advise patients to consult their healthcare provider if new onset or worsening eye symptoms develop [see Warnings and Precautions (5.2)].

Eosinophilic Conditions

Advise patients to notify their healthcare provider if they present with clinical features of eosinophilic pneumonia or eosinophilic granulomatosis with polyangiitis [see Warnings and Precautions (5.3)].

Not for Acute Symptoms of Asthma or Chronic Obstructive Pulmonary Disease or Acute Deteriorating Disease

Inform patients that DUPIXENT does not treat acute symptoms or acute exacerbations of asthma or COPD. Inform patients to seek medical advice if their asthma or COPD remains uncontrolled or worsens after initiation of treatment with DUPIXENT [see Warnings and Precautions (5.4)].

Reduction in Corticosteroid Dosage

Inform patients to not discontinue systemic or inhaled corticosteroids except under the direct supervision of a healthcare provider. Inform patients that reduction in corticosteroid dose may be associated with systemic withdrawal symptoms and/or unmask conditions previously suppressed by systemic corticosteroid therapy [see Warnings and Precautions (5.5)].

Patients with Co-morbid Asthma

Advise patients with co-morbid asthma not to adjust or stop their asthma treatment without talking to their healthcare providers [see Warnings and Precautions (5.6)].

Psoriasis

Advise patients that cases of new-onset psoriasis have been reported with the use of DUPIXENT. Advise patients to report new-onset psoriasis symptoms to their healthcare provider [see Warnings and Precautions (5.7)].

Arthralgia and Psoriatic Arthritis

Advise patients that cases of new-onset psoriatic arthritis have been reported with the use of DUPIXENT. Advise patients to report new onset or worsening joint symptoms to their healthcare provider [see Warnings and Precautions (5.8)].

Parasitic (Helminth) Infections

Advise patients to notify their healthcare provider if they present with clinical features consistent with helminthic infection [see Warnings and Precautions (5.9)].

Vaccinations

Advise patients that vaccination with live vaccines is not recommended immediately prior to and while they are receiving DUPIXENT. Instruct patients to inform their healthcare provider that they are taking DUPIXENT prior to a potential vaccination [see Warnings and Precautions (5.10)].

Manufactured by:
Regeneron Pharmaceuticals, Inc.
Tarrytown, NY 10591
U.S. License No. 1760

Marketed by:
sanofi-aventis U.S. LLC (Morristown, NJ 07960) and
Regeneron Pharmaceuticals, Inc. (Tarrytown, NY 10591)

For patent information: www.dupixent-patents.com

DUPIXENT® is a registered trademark of Sanofi Biotechnology

© 2025 Regeneron Pharmaceuticals, Inc. / sanofi-aventis U.S. LLC. All rights reserved.

PATIENT INFORMATION
DUPIXENT® (DU-pix-ent)
(dupilumab)
injection, for subcutaneous use

What is DUPIXENT?
DUPIXENT is a prescription medicine used:

- to treat adults and children 6 months of age and older with moderate-to-severe eczema (atopic dermatitis or AD) that is not well controlled with prescription therapies used on the skin (topical), or who cannot use topical therapies. DUPIXENT can be used with or without topical corticosteroids.
- with other asthma medicines for the maintenance treatment of moderate-to-severe asthma in adults and children 6 years of age and older whose asthma is not controlled with their current asthma medicines. DUPIXENT helps prevent severe asthma attacks (exacerbations) and can improve your breathing. DUPIXENT may also help reduce the amount of oral corticosteroids you need while preventing severe asthma attacks and improving your breathing.
- with other medicines for the maintenance treatment of chronic rhinosinusitis with nasal polyps (CRSwNP) in adults and children 12 years of age and older whose disease is not controlled.
- to treat adults and children 1 year of age and older with eosinophilic esophagitis (EoE), who weigh at least 33 pounds (15 kg).
- to treat adults with prurigo nodularis (PN).
- with other medicines for the maintenance treatment of adults with inadequately controlled chronic obstructive pulmonary disease (COPD) and a high number of blood eosinophils (a type of white blood cell that may contribute to your COPD). DUPIXENT is used to reduce the number of flare-ups (the worsening of your COPD symptoms for several days) and can improve your breathing.
- to treat chronic spontaneous urticaria (CSU) in adults and children 12 years of age and older, who continue to have hives that are not controlled with H1 antihistamine treatment.
- to treat adults with bullous pemphigoid (BP).

DUPIXENT is not used to relieve sudden breathing problems and will not replace an inhaled rescue medicine or to treat any other forms of hives (urticaria).
DUPIXENT works by blocking two proteins that contribute to a type of inflammation that plays a major role in AD, asthma, CRSwNP, EoE, PN, COPD, CSU, and BP.
It is not known if DUPIXENT is safe and effective in children with:

- AD under 6 months of age.
- Asthma under 6 years of age.
- CRSwNP under 12 years of age.
- EoE under 1 year of age, or who weigh less than 33 pounds (15 kg).

- PN under 18 years of age.
- COPD under 18 years of age. COPD is most often seen in adults.
- CSU under 12 years of age, or who weigh less than 66 pounds (30 kg).
- BP under 18 years of age. BP is most often seen in adults.

Do not use DUPIXENT if you are allergic to dupilumab or to any of the ingredients in DUPIXENT. See the end of this Patient Information leaflet for a complete list of ingredients in DUPIXENT.

Before using DUPIXENT, tell your healthcare provider about all your medical conditions, including if you:

- have eye problems.
- have a parasitic (helminth) infection.
- are scheduled to receive any vaccinations. You should not receive a "live vaccine" right before and during treatment with DUPIXENT.
- are pregnant or plan to become pregnant. It is not known whether DUPIXENT will harm your unborn baby.
  Pregnancy Exposure Registry. There is a pregnancy exposure registry for women who use DUPIXENT during pregnancy. The purpose of this registry is to collect information about the health of you and your baby. Your healthcare provider can enroll you in this registry. You may also enroll yourself or get more information about the registry by calling 1-877-311-8972 or going to https://mothertobaby.org/ongoing-study/dupixent/.
- are breastfeeding or plan to breastfeed. It is not known whether DUPIXENT passes into your breast milk.

Tell your healthcare provider about all of the medicines you take, including prescription and over-the-counter medicines, vitamins, and herbal supplements.
Especially tell your healthcare provider if you:

- are taking oral, topical, or inhaled corticosteroid medicines
- have asthma and use an asthma medicine
- have AD, CRSwNP, EoE, PN, COPD, CSU, or BP and also have asthma

Do not change or stop your other medicines, including corticosteroid medicine or other asthma medicine, without talking to your healthcare provider. This may cause other symptoms that were controlled by those medicines to come back.

How should I use DUPIXENT?

- See the detailed "Instructions for Use" that comes with DUPIXENT for information on how to prepare and inject DUPIXENT and how to properly store and throw away (dispose of) used DUPIXENT pre-filled syringes and pre-filled pens.
- Use DUPIXENT exactly as prescribed by your healthcare provider.
- Your healthcare provider will tell you how much DUPIXENT to inject and how often to inject it.
- DUPIXENT comes as a single-dose pre-filled syringe with needle shield or as a pre-filled pen.
  - The DUPIXENT pre-filled pen is only for use in adults and children 2 years of age and older.
  - The DUPIXENT pre-filled syringe is for use in adults and children 6 months of age and older.
- DUPIXENT is given as an injection under the skin (subcutaneous injection).
- If your healthcare provider decides that you or a caregiver can give the injections of DUPIXENT, you or your caregiver should receive training on the right way to prepare and inject DUPIXENT. Do not try to inject DUPIXENT until you have been shown the right way by your healthcare provider. In children 12 years of age and older, it is recommended that DUPIXENT be given by or under the supervision of an adult. In children 6 months to less than 12 years of age, DUPIXENT should be given by a caregiver.
- If your dose schedule is every week and you miss a dose of DUPIXENT: Give the DUPIXENT injection as soon as possible and start a new every week dose schedule from the time you remember to take your DUPIXENT injection.
- If your dose schedule is every 2 weeks and you miss a dose of DUPIXENT: Give the DUPIXENT injection within 7 days from the missed dose, then continue with your original schedule. If the missed dose is not given within 7 days, start a new every 2-week dose schedule from the time you remember to take your DUPIXENT injection.
- If your dose schedule is every 4 weeks and you miss a dose of DUPIXENT: Give the DUPIXENT injection within 7 days from the missed dose, then continue with your original schedule. If the missed dose is not given within 7 days, start a new every 4-week dose schedule from the time you remember to take your DUPIXENT injection.
- If you inject too much DUPIXENT, call your healthcare provider or Poison Help line at 1-800-222-1222 or go to the nearest hospital emergency room right away.
- Your healthcare provider may prescribe other medicines to use with DUPIXENT. Use the other prescribed medicines exactly as your healthcare provider tells you to.

What are the possible side effects of DUPIXENT?
DUPIXENT can cause serious side effects, including:

- Allergic reactions. DUPIXENT can cause allergic reactions, including skin reactions, that can sometimes be severe. Stop using DUPIXENT and tell your healthcare provider or get emergency help right away if you get any of the following signs or symptoms:

- breathing problems or wheezing
- fast pulse
- fever
- general ill feeling
- swollen lymph nodes
- joint pain

- swelling of the face, lips, mouth, tongue, or throat
- hives
- itching
- nausea or vomiting
- cramps in your stomach-area

- fainting, dizziness, feeling lightheaded
- skin rash, including rash that looks like a bullseye, painful red or blue bumps under the skin, or red pus-filled spots on the skin

- Eye problems. Tell your healthcare provider if you have any new or worsening eye problems, including eye pain or changes in vision, such as blurred vision. Your healthcare provider may send you to an ophthalmologist for an eye exam if needed.
- Inflammation of your blood vessels. Rarely, this can happen in people with asthma who receive DUPIXENT. This may happen in people who also take a steroid medicine by mouth, that is being stopped or the dose is being lowered. Tell your healthcare provider right away if you get:

- rash
- worsening shortness of breath
- persistent fever

- chest pain
- brown or dark colored urine
- a feeling of pins and needles or numbness of your arms or legs

- Psoriasis. This can happen in people with atopic dermatitis and asthma who receive DUPIXENT. Tell your healthcare provider about any new skin symptoms. Your healthcare provider may send you to a dermatologist for an examination if needed.
- Joint aches and pain. Joint aches and pain can happen in people who use DUPIXENT. Some people have had trouble walking or moving due to their joint symptoms, and in some cases needed to be hospitalized. Tell your healthcare provider about any new or worsening joint symptoms. Your healthcare provider may stop DUPIXENT if you develop joint symptoms.

The most common side effects of DUPIXENT include:

- injection site reactions
- upper respiratory tract infections
- eye problems, including eye and eyelid inflammation, redness, swelling, itching, eye infection, dry eye, and blurred vision
- herpes virus infections
- common cold symptoms (nasopharyngitis)
- cold sores in your mouth or on your lips
- high count of a certain white blood cell (eosinophilia)
- viral infection
- back pain
- inflammation inside the nose (rhinitis)

- dizziness
- muscle pain
- diarrhea
- pain in the throat (oropharyngeal pain)
- stomach problems (gastritis)
- joint pain (arthralgia)
- trouble sleeping (insomnia)
- toothache
- parasitic (helminth) infections
- headache
- urinary tract infection

Tell your healthcare provider if you have any side effect that bothers you or that does not go away.
These are not all of the possible side effects of DUPIXENT.
Call your doctor for medical advice about side effects. You may report side effects to FDA at 1-800-FDA-1088.

How should I store DUPIXENT?

- Store DUPIXENT in the refrigerator between 36ºF to 46ºF (2ºC to 8ºC).
- Store DUPIXENT in the original carton to protect from light.
- DUPIXENT can be stored at room temperature up to 77°F (25°C) up to 14 days. Throw away (dispose of) any DUPIXENT that has been left at room temperature for longer than 14 days.
- Do not heat or put DUPIXENT into direct sunlight.
- Do not freeze. Do not shake.

Keep DUPIXENT and all medicines out of the reach of children.

General information about the safe and effective use of DUPIXENT.
Medicines are sometimes prescribed for purposes other than those listed in a Patient Information leaflet. Do not use DUPIXENT for a condition for which it was not prescribed. Do not give DUPIXENT to other people, even if they have the same symptoms that you have. It may harm them. You can ask your pharmacist or healthcare provider for information about DUPIXENT that is written for health professionals.

What are the ingredients in DUPIXENT?
Active ingredient: dupilumab
Inactive ingredients: L-arginine hydrochloride, L-histidine, polysorbate 80, sodium acetate, sucrose, and water for injection.
Manufactured by: Regeneron Pharmaceuticals, Inc., Tarrytown, NY 10591 U.S. License No. 1760
Marketed by: sanofi-aventis U.S. LLC (Morristown, NJ 07960) and Regeneron Pharmaceuticals, Inc. (Tarrytown, NY 10591)
DUPIXENT® is a registered trademark of Sanofi Biotechnology / © 2025 Regeneron Pharmaceuticals, Inc. / sanofi-aventis U.S. LLC. All rights reserved.
For more information about DUPIXENT, go to www.DUPIXENT.com or call 1-844-DUPIXENT (1-844-387-4936).

This Patient Information has been approved by the U.S. Food and Drug Administration.

Revised: June 2025

INSTRUCTIONS FOR USE DUPIXENT® (DU-pix-ent) (dupilumab) injection, for subcutaneous use Single-Dose Pre-filled Syringe with Needle Shield

Read this Instructions for Use before using the DUPIXENT Pre-filled Syringe. Do not inject yourself or someone else until you have been shown how to inject DUPIXENT. Your healthcare provider can show you or your caregiver how to prepare and inject a dose of DUPIXENT before you try to do it yourself the first time. Keep these instructions for future use. Call your healthcare provider if you have any questions.

This device is a Single-Dose Pre-filled Syringe (called "DUPIXENT Syringe" in these instructions). It contains 300 mg of DUPIXENT for injection under the skin (subcutaneous injection).

The parts of the DUPIXENT Syringe are shown below:

Important Information

- Read all of the instructions carefully before using the DUPIXENT Syringe.
- Ask your healthcare provider how often you will need to inject the medicine.
- In children 12 years of age and older, it is recommended that DUPIXENT be administered by or under supervision of an adult.
- In children 6 months to less than 12 years of age, DUPIXENT should be given by a caregiver.
- Rotate the injection site each time you inject.
- Do not use the DUPIXENT Syringe if it has been dropped on a hard surface or damaged.
- Do not use the DUPIXENT Syringe if the Needle Cap is missing or not securely attached.
- Do not touch the Plunger Rod until you are ready to inject.
- Do not inject through clothes.
- Do not get rid of any air bubble in the DUPIXENT Syringe.

- To reduce the risk of accidental needle sticks, each pre-filled syringe has a Needle Shield that is automatically activated to cover the needle after you have given your injection.
- Do not pull back on the Plunger Rod at any time.
- Do not remove the Needle Cap until just before you give the injection.
- Throw away (dispose of) the used DUPIXENT Single-Dose Pre-filled Syringe right away after use. See "Step 13: Dispose" below.
- Do not re-use a DUPIXENT Single-Dose Pre-filled Syringe.

How should I store DUPIXENT?

- Keep DUPIXENT Syringes and all medicines out of the reach of children.
- Store DUPIXENT Syringes in the refrigerator between 36°F to 46°F (2°C to 8°C).
- Store DUPIXENT Syringes in the original carton to protect them from light.
- DUPIXENT Syringes can be stored at room temperature up to 77°F (25°C) up to 14 days. Throw away (dispose of) any DUPIXENT Syringes that have been left at room temperature for longer than 14 days.
- Do not shake the DUPIXENT Syringe.
- Do not heat the DUPIXENT Syringe.
- Do not freeze the DUPIXENT Syringe.
- Do not put the DUPIXENT Syringe into direct sunlight.

Step 1: Remove

Remove the DUPIXENT Syringe from the carton by holding the middle of the Syringe Body.

Do not pull off the Needle Cap until you are ready to inject.

Do not use the DUPIXENT Syringe if it has been dropped on a hard surface or damaged.

Step 2: Prepare

Ensure you have the following:

- the DUPIXENT Pre-filled Syringe
- 1 alcohol wipe*
- 1 cotton ball or gauze*
- a sharps disposal container* (See Step 13)

*Items not included in the carton

Step 3: Check

When you receive your DUPIXENT Syringes, always check to see that:

- you have the correct medicine and dose.
- the expiration date on the Single-Dose Pre-filled Syringe has not passed.

Do not use the DUPIXENT Syringe if the expiration date has passed.

Step 4: Inspect

Look at the medicine through the Viewing Window on the DUPIXENT Syringe:

Check to see if the liquid is clear and colorless to pale yellow.

Note: You may see an air bubble, this is normal.

Do not use the DUPIXENT Syringe if the liquid is discolored or cloudy, or if it contains visible flakes or particles.

Step 5: Wait 45 minutes

Lay the DUPIXENT Syringe on a flat surface and let it naturally warm to room temperature for at least 45 minutes.

Do not heat the DUPIXENT Syringe.

Do not put the DUPIXENT Syringe into direct sunlight.

Do not keep DUPIXENT Syringes at room temperature for more than 14 days. Throw away (dispose of) any DUPIXENT Syringes that have been left at room temperature for longer than 14 days.

Step 6: Choose your injection site

- You can inject into your thigh or stomach, except for the 2 inches (5 cm) around your belly button (navel).
- If a caregiver injects your dose, they can also use the outer area of the upper arm.
- Choose a different site each time you inject DUPIXENT.

Do not inject into skin that is tender, damaged, bruised or scarred.

Step 7: Clean

Wash your hands.

Clean the injection site with an alcohol wipe.

Let your skin dry before injecting.

Do not touch the injection site again or blow on it before the injection.

Step 8: Remove Needle Cap

Hold the DUPIXENT Syringe in the middle of the Syringe Body with the Needle pointing away from you and pull off the Needle Cap.

Do not put the Needle Cap back on.

Do not touch the Needle.

Inject your medicine right away after removing the Needle Cap.

Step 9: Pinch

Pinch a fold of skin at the injection site (thigh or stomach, except 2 inches around your belly button, or outer area of the upper arm if injected by your caregiver). The figure below shows an example of pinching a fold of skin on your stomach.

Step 10: Insert

Insert the Needle completely into the fold of the skin at about a 45° angle.

Step 11: Push

Relax the pinch.

Push the Plunger Rod down slowly and steadily as far as it will go until the DUPIXENT Syringe is empty.

Note: You will feel some resistance. This is normal.

Step 12: Release and Remove

Lift your thumb to release the Plunger Rod until the Needle is covered by the Needle Shield and then remove the Syringe from the injection site.

Lightly press a cotton ball or gauze on the injection site if you see any blood.

Do not put the Needle Cap back on.

Do not rub your skin after the injection.

Step 13: Dispose

Put your used Needles, DUPIXENT Syringes, and Needle Caps in a FDA-cleared sharps disposal container right away after use.

Do not dispose of (throw away) Needles, DUPIXENT Syringes, and Needle Caps in your household trash.

If you do not have a FDA-cleared sharps disposal container, you may use a household container that is:

- made of a heavy-duty plastic,
- can be closed with a tight-fitting, puncture-resistant lid, without sharps being able to come out,
- upright and stable during use,
- leak-resistant, and
- properly labeled to warn of hazardous waste inside the container

When your sharps disposal container is almost full, you will need to follow your community guidelines for the right way to dispose of your sharps disposal container. There may be state or local laws about how you should throw away used Needles and Syringes.

For more information about safe sharps disposal, and for specific information about sharps disposal in the state that you live in, go to the FDA's website at: http://www.fda.gov/safesharpsdisposal

Do not dispose of your used sharps disposal container in your household trash unless your community guidelines permit this. Do not recycle your used sharps disposal container.

Do not put the Needle Cap back on.

Manufactured by: Regeneron Pharmaceuticals, Inc. Tarrytown, NY 10591
U.S. License No. 1760

Marketed by: sanofi-aventis U.S. LLC (Bridgewater, NJ 08807) and Regeneron Pharmaceuticals, Inc. (Tarrytown, NY 10591)
DUPIXENT® is a registered trademark of Sanofi Biotechnology

© 2023 Regeneron Pharmaceuticals, Inc. / sanofi-aventis U.S. LLC. All rights reserved.

This Instructions for Use has been approved by the U.S. Food and Drug Administration.

Revised: July 2023

INSTRUCTIONS FOR USE DUPIXENT® (DU-pix-ent) (dupilumab) injection, for subcutaneous use Single-Dose Pre-filled Syringe with Needle Shield

Read this Instructions for Use before using the DUPIXENT Pre-filled Syringe. Do not inject yourself or someone else until you have been shown how to inject DUPIXENT. Your healthcare provider can show you or your caregiver how to prepare and inject a dose of DUPIXENT before you try to do it yourself the first time. Keep these instructions for future use. Call your healthcare provider if you have any questions.

This device is a Single-Dose Pre-filled Syringe (called "DUPIXENT Syringe" in these instructions). It contains 200 mg of DUPIXENT for injection under the skin (subcutaneous injection).

The parts of the DUPIXENT Syringe are shown below:

Important Information

- Read all of the instructions carefully before using the DUPIXENT Syringe.
- Ask your healthcare provider how often you will need to inject the medicine.
- In children 12 years of age and older, it is recommended that DUPIXENT be administered by or under supervision of an adult.
- In children 6 months to less than 12 years of age, DUPIXENT should be given by a caregiver.
- Rotate the injection site each time you inject.
- Do not use the DUPIXENT Syringe if it has been dropped on a hard surface or damaged.
- Do not use the DUPIXENT Syringe if the Needle Cap is missing or not securely attached.
- Do not touch the Plunger Rod until you are ready to inject.
- Do not inject through clothes.
- Do not get rid of any air bubble in the DUPIXENT Syringe.

- To reduce the risk of accidental needle sticks, each pre-filled syringe has a Needle Shield that is automatically activated to cover the needle after you have given your injection.
- Do not pull back on the Plunger Rod at any time.
- Do not remove the Needle Cap until just before you give the injection.
- Throw away (dispose of) the used DUPIXENT Single-Dose Pre-filled Syringe right away after use. See "Step 13: Dispose" below.
- Do not re-use a DUPIXENT Single-Dose Pre-filled Syringe.

How should I store DUPIXENT?

- Keep DUPIXENT Syringes and all medicines out of the reach of children.
- Store DUPIXENT Syringes in the refrigerator between 36°F to 46°F (2°C to 8°C).
- Store DUPIXENT Syringes in the original carton to protect them from light.
- DUPIXENT Syringes can be stored at room temperature up to 77°F (25°C) up to 14 days. Throw away (dispose of) any DUPIXENT Syringes that have been left at room temperature for longer than 14 days.
- Do not shake the DUPIXENT Syringe.
- Do not heat the DUPIXENT Syringe.
- Do not freeze the DUPIXENT Syringe.
- Do not put the DUPIXENT Syringe into direct sunlight.

Step 1: Remove

Remove the DUPIXENT Syringe from the carton by holding the middle of the Syringe Body.

Do not pull off the Needle Cap until you are ready to inject.

Do not use the DUPIXENT Syringe if it has been dropped on a hard surface or damaged.

Step 2: Prepare

Ensure you have the following:

- the DUPIXENT Pre-filled Syringe
- 1 alcohol wipe*
- 1 cotton ball or gauze*
- a sharps disposal container* (See Step 13)

*Items not included in the carton

Step 3: Check

When you receive your DUPIXENT Syringes, always check to see that:

- you have the correct medicine and dose.
- the expiration date on the Single-Dose Pre-filled Syringe has not passed.

Do not use the DUPIXENT Syringe if the expiration date has passed.

Step 4: Inspect

Look at the medicine through the Viewing Window on the DUPIXENT Syringe:

Check to see if the liquid is clear and colorless to pale yellow.

Note: You may see an air bubble, this is normal.

Do not use the DUPIXENT Syringe if the liquid is discolored or cloudy, or if it contains visible flakes or particles.

Step 5: Wait 30 minutes

Lay the DUPIXENT Syringe on a flat surface and let it naturally warm to room temperature for at least 30 minutes.

Do not heat the DUPIXENT Syringe.

Do not put the DUPIXENT Syringe into direct sunlight.

Do not keep DUPIXENT Syringes at room temperature for more than 14 days. Throw away (dispose of) any DUPIXENT Syringes that have been left at room temperature for longer than 14 days.

Step 6: Choose your injection site

- You can inject into your thigh or stomach, except for the 2 inches (5 cm) around your belly button (navel).
- If a caregiver injects your dose, they can also use the outer area of the upper arm.
- Choose a different site each time you inject DUPIXENT.

Do not inject into skin that is tender, damaged, bruised or scarred.

Step 7: Clean

Wash your hands.

Clean the injection site with an alcohol wipe.

Let your skin dry before injecting.

Do not touch the injection site again or blow on it before the injection.

Step 8: Remove Needle Cap

Hold the DUPIXENT Syringe in the middle of the Syringe Body with the Needle pointing away from you and pull off the Needle Cap.

Do not put the Needle Cap back on.

Do not touch the Needle.

Inject your medicine right away after removing the Needle Cap.

Step 9: Pinch

Pinch a fold of skin at the injection site (thigh or stomach, except 2 inches around your belly button, or outer area of the upper arm if injected by your caregiver). The figure below shows an example of pinching a fold of skin on your stomach.

Step 10: Insert

Insert the Needle completely into the fold of the skin at about a 45° angle.

Step 11: Push

Relax the pinch.

Push the Plunger Rod down slowly and steadily as far as it will go until the DUPIXENT Syringe is empty.

Note: You will feel some resistance. This is normal.

Step 12: Release and Remove

Lift your thumb to release the Plunger Rod until the Needle is covered by the Needle Shield and then remove the Syringe from the injection site.

Lightly press a cotton ball or gauze on the injection site if you see any blood.

Do not put the Needle Cap back on.

Do not rub your skin after the injection.

Step 13: Dispose

Put your used Needles, DUPIXENT Syringes, and Needle Caps in a FDA-cleared sharps disposal container right away after use.

Do not dispose of (throw away) Needles, DUPIXENT Syringes, and Needle Caps in your household trash.

If you do not have a FDA-cleared sharps disposal container, you may use a household container that is:

- made of a heavy-duty plastic,
- can be closed with a tight-fitting, puncture-resistant lid, without sharps being able to come out,
- upright and stable during use,
- leak-resistant, and
- properly labeled to warn of hazardous waste inside the container

When your sharps disposal container is almost full, you will need to follow your community guidelines for the right way to dispose of your sharps disposal container. There may be state or local laws about how you should throw away used Needles and Syringes.

For more information about safe sharps disposal, and for specific information about sharps disposal in the state that you live in, go to the FDA's website at: http://www.fda.gov/safesharpsdisposal

Do not dispose of your used sharps disposal container in your household trash unless your community guidelines permit this. Do not recycle your used sharps disposal container.

Do not put the Needle Cap back on.

Manufactured by: Regeneron Pharmaceuticals, Inc. Tarrytown, NY 10591
U.S. License No. 1760

Marketed by: sanofi-aventis U.S. LLC (Bridgewater, NJ 08807) and Regeneron Pharmaceuticals, Inc. (Tarrytown, NY 10591)
DUPIXENT® is a registered trademark of Sanofi Biotechnology

© 2023 Regeneron Pharmaceuticals, Inc. / sanofi-aventis U.S. LLC. All rights reserved.

This Instructions for Use has been approved by the U.S. Food and Drug Administration.

Revised: July 2023

Instructions for Use
DUPIXENT® (DU-pix-ent)
(dupilumab)
injection, for subcutaneous use
Single-Dose Pre-filled Pen (300 mg/2 mL)

This Instructions for Use contains information on how to inject DUPIXENT.

Read this Instructions for Use before using the DUPIXENT Pre-filled Pen. Do not inject yourself or someone else until you have been shown how to inject DUPIXENT. Your healthcare provider can show you or your caregiver how to prepare and inject a dose of DUPIXENT before you try to do it yourself for the first time. Keep this Instructions for Use. Call your healthcare provider if you have any questions.

This DUPIXENT Pre-filled Pen is only for use in adults and children aged 2 years and older.

This DUPIXENT Pre-filled Pen is a single-dose device. It contains 300 mg of DUPIXENT for injection under the skin (subcutaneous injection).

The parts of the DUPIXENT Pre-filled Pen are shown below:

Important Information

- Read all of the instructions carefully before using the DUPIXENT Pre-filled Pen.
- Ask your healthcare provider how often you will need to inject the medicine.
- In children 12 years of age and older, it is recommended that DUPIXENT be administered by or under supervision of an adult.
- In children 2 years to less than 12 years of age, DUPIXENT should be given by a caregiver.
- Choose a different injection site for each injection.
- Do not press or touch the Yellow Needle Cover with your fingers.
- Do not inject through clothes.
- Do not remove the Green Cap until just before you give the injection.
- Do not try to put the Green Cap back on the DUPIXENT Pre-filled Pen.
- Throw away (dispose of) the used DUPIXENT Pre-filled Pen right away after use.
- Do not re-use a DUPIXENT Pre-filled Pen.

Storing DUPIXENT

- Store unused DUPIXENT Pre-filled Pens in the refrigerator between 36ºF to 46ºF (2ºC to 8ºC).
- Store DUPIXENT Pre-filled Pens in the original carton to protect from light.
- If necessary, you may keep DUPIXENT Pre-filled Pens at room temperature up to 77ºF (25ºC) for up to 14 days.
- Do not store DUPIXENT Pre-filled Pens at room temperature more than 77ºF (25ºC).
- After removing a DUPIXENT Pre-filled Pen from the refrigerator, it must be used within 14 days or thrown away (disposed of).
- Do not shake the DUPIXENT Pre-filled Pen at any time.
- Do not heat the DUPIXENT Pre-filled Pen.
- Do not freeze the DUPIXENT Pre-filled Pen.
- Do not put the DUPIXENT Pre-filled Pen into direct sunlight.
- Keep DUPIXENT Pre-filled Pens and all medicines out of the reach of children.

A. Get ready to inject

A1. Gather supplies

Find a clean, flat work surface. Make sure you have the following supplies:

A2. Check the Pen

- Do not use the DUPIXENT Pre-filled Pen if it has been damaged.
- Do not use the DUPIXENT Pre-filled Pen if the Green Cap is missing or not securely attached.
- Do not use the DUPIXENT Pre-filled Pen if the Window is yellow before use.

A3. Look at the Label

- Check to be sure that you have the correct Medicine and dose.

- Check the expiration date.
- Do not use the DUPIXENT Pre-filled Pen if the expiration date has passed.

A4. Check the Medicine

- Look at the Medicine through the Window: it should be clear and colorless to pale yellow.
- Note: You may see an air bubble, this is normal.
- Do not use the DUPIXENT Pre-filled Pen if the liquid is discolored or cloudy, or if it contains visible flakes or particles.

A5. Wait 45 minutes

- Lay the DUPIXENT Pre-filled Pen on a flat surface and let it warm up at room temperature less than 77ºF (25ºC) for at least 45 minutes.
- Do not heat the DUPIXENT Pre-filled Pen in a microwave, hot water or direct sunlight.

B. Choose and prepare your injection site

B1. Wash your hands well with soap and water

B2. Choose an injection site

- Thigh
- Stomach except for the 2 inches (5 cm) around your belly button (navel).
- A caregiver can also inject in the outer area of the upper arm.
- Choose a different site for each injection.
- Do not inject into skin that is tender, damaged, has bruises or scars, or into areas with visible veins.
- Do not inject through clothes.

B3. Prepare the injection site

- Clean the injection site with an alcohol wipe.
- Let the skin dry before injecting.
- Do not touch the injection site again or blow on it before the injection.

C. Give the injection

C1. Remove Green Cap

- Remove the Green Cap by pulling it straight off, as shown. Do not twist the Green Cap off.
- Do not remove the Green Cap until you are ready to inject.
- Do not press or touch the Yellow Needle Cover with your fingers. The Needle is inside.
- Do not put the Green Cap back on the DUPIXENT Pre-filled Pen after you have removed it.

C2. Pinch Skin and Place
Pinch the skin before and during the injection.
- Hold the DUPIXENT Pre-filled Pen as shown so that you can see the Window. Place the Yellow Needle Cover on the skin.
- Place the Yellow Needle Cover on the skin at approximately a 90-degree angle.
- Pinching is not needed for adults and children aged 12 years and older.
C3. Press down ➜ Watch Window turn fully yellow ➜ Then count to 5
Press and hold the DUPIXENT Pre-filled Pen firmly against the skin until you cannot see the Yellow Needle Cover.; - There will be a "click" when the injection starts, and - The Window will start to turn yellow. - Keep pressing the DUPIXENT Pre-filled Pen against the skin. | Keep pressing the DUPIXENT Pre-filled Pen against the skin and watch the window:; - The Window will turn completely yellow, and - You will hear a 2nd "click". - Keep pressing the DUPIXENT Pre-filled Pen against the skin. | Keep pressing the DUPIXENT Pre-filled Pen against the skin and count to 5 to make sure you get your full dose.

Pinching of the skin is not needed for adults and children aged 12 years and older.

C4. Remove

- After you have completed the injection pull straight up to remove DUPIXENT Pre-filled Pen from the skin. The Yellow Needle Cover will cover the needle.
- If you see any blood at the site, lightly dab a cotton ball or gauze pad.
- Do not rub the skin after the injection.
- If the Window does not turn completely Yellow, or if it looks like medicine is still coming out of the pen, you may not have received a full dose. Dispose of (throw away) the pen and contact your healthcare provider right away.
- Do not give a second dose without speaking to your healthcare provider.

D. Dispose of used DUPIXENT Pre-filled Pen

How to Dispose of (throw away) DUPIXENT Pre-filled Pen:
Put the used DUPIXENT Pre-filled Pens and Green Caps in a FDA-cleared sharps disposal container right away after use.

Do not dispose of (throw away) DUPIXENT Pre-filled Pens and Green Caps in your household trash.

If you do not have a FDA-cleared sharps disposal container, you may use a household container that is:

- made of a heavy-duty plastic,
- can be closed with a tightfitting, puncture-resistant lid, without sharps being able to come out,
- upright and stable during use,
- leak-resistant, and
- properly labeled to warn of hazardous waste inside the container.

When your sharps disposal container is almost full, you will need to follow your community guidelines for the right way to dispose of your sharps disposal container. There may be state or local laws about how you should throw away used DUPIXENT Pre-filled Pens.
For more information about safe sharps disposal, and for specific information about sharps disposal in the state that you live in, go to the FDA's website at: http://www.fda.gov/safesharpsdisposal

Do not dispose of your used sharps disposal container in your household trash unless your community guidelines permit this.

Do not recycle your used sharps disposal container.

Keep your sharps disposal container out of the reach of children.

Manufactured by:
Regeneron Pharmaceuticals, Inc.
Tarrytown, NY 10591
U.S. License No. 1760
Marketed by:
sanofi-aventis U.S. LLC (Bridgewater, NJ 08807) and
Regeneron Pharmaceuticals, Inc. (Tarrytown, NY 10591)
DUPIXENT® is a registered trademark of Sanofi Biotechnology
© 2023 Regeneron Pharmaceuticals, Inc. / sanofi-aventis U.S. LLC. All rights reserved.

This Instructions for Use has been approved by the U.S. Food and Drug Administration.

Revised: July 2023

Instructions for Use

DUPIXENT® (DU-pix-ent)
(dupilumab)
injection, for subcutaneous use
Single-Dose Pre-filled Pen (200 mg/1.14 mL)

This Instructions for Use contains information on how to inject DUPIXENT.

Read this Instructions for Use before using the DUPIXENT Pre-filled Pen. Do not inject yourself or someone else until you have been shown how to inject DUPIXENT. Your healthcare provider can show you or your caregiver how to prepare and inject a dose of DUPIXENT before you try to do it yourself for the first time. Keep this Instructions for Use. Call your healthcare provider if you have any questions.

This DUPIXENT Pre-filled Pen is only for use in adults and children aged 2 years and older.

This DUPIXENT Pre-filled Pen is a single-dose device. It contains 200 mg of DUPIXENT for injection under the skin (subcutaneous injection).

The parts of the DUPIXENT Pre-filled Pen are shown below:

Important Information

- Read all of the instructions carefully before using the DUPIXENT Pre-filled Pen.
- Ask your healthcare provider how often you will need to inject the medicine.
- In children 12 years of age and older, it is recommended that DUPIXENT be administered by or under supervision of an adult.
- In children 2 years to less than 12 years of age, DUPIXENT should be given by a caregiver.
- Choose a different injection site for each injection.
- Do not press or touch the Orange Needle Cover with your fingers.
- Do not inject through clothes.
- Do not remove the Yellow Cap until just before you give the injection.
- Do not try to put the Yellow Cap back on the DUPIXENT Pre-filled Pen.
- Throw away (dispose of) the used DUPIXENT Pre-filled Pen right away after use.
- Do not re-use a DUPIXENT Pre-filled Pen.

Storing DUPIXENT

- Store unused DUPIXENT Pre-filled Pens in the refrigerator between 36°F to 46°F (2°C to 8°C).
- Store DUPIXENT Pre-filled Pens in the original carton to protect from light.
- If necessary, you may keep DUPIXENT Pre-filled Pens at room temperature up to 77°F (25°C) for up to 14 days.
- Do not store DUPIXENT Pre-filled Pens at room temperature more than 77°F (25°C).
- After removing a DUPIXENT Pre-filled Pen from the refrigerator, it must be used within 14 days or thrown away (disposed of).
- Do not shake the DUPIXENT Pre-filled Pen at any time.
- Do not heat the DUPIXENT Pre-filled Pen.
- Do not freeze the DUPIXENT Pre-filled Pen.
- Do not put the DUPIXENT Pre-filled Pen into direct sunlight.
- Keep DUPIXENT Pre-filled Pens and all medicines out of the reach of children.

A. Get ready to inject

A1. Gather supplies

Find a clean, flat work surface. Make sure you have the following supplies:

A2. Check the Pen

- Do not use the DUPIXENT Pre-filled Pen if it has been damaged.
- Do not use the DUPIXENT Pre-filled Pen if the Yellow Cap is missing or not securely attached.
- Do not use the DUPIXENT Pre-filled Pen if the Window is yellow before use.

A3. Look at the Label

- Check to be sure that you have the correct Medicine and dose.

- Check the expiration date.
- Do not use the DUPIXENT Pre-filled Pen if the expiration date has passed.

A4. Check the Medicine

- Look at the Medicine through the Window: it should be clear and colorless to pale yellow.
- Note: You may see an air bubble, this is normal.
- Do not use the DUPIXENT Pre-filled Pen if the liquid is discolored or cloudy, or if it contains visible flakes or particles.

A5. Wait 30 minutes

- Lay the DUPIXENT Pre-filled Pen on a flat surface and let it warm up at room temperature less than 77°F (25°C) for at least 30 minutes.
- Do not heat the DUPIXENT Pre-filled Pen in a microwave, hot water or direct sunlight.

B. Choose and prepare your injection site

B1. Wash your hands well with soap and water

B2. Choose an injection site

- Thigh
- Stomach except for the 2 inches (5 cm) around your belly button (navel).
- A caregiver can also inject in the outer area of the upper arm.
- Choose a different site for each injection.
- Do not inject into skin that is tender, damaged, has bruises or scars, or into areas with visible veins.
- Do not inject through clothes.

B3. Prepare the injection site

- Clean the injection site with an alcohol wipe.
- Let the skin dry before injecting.
- Do not touch the injection site again or blow on it before the injection.

C. Give the injection

C1. Remove Yellow Cap

- Remove the Yellow Cap by pulling it straight off, as shown. Do not twist the Yellow Cap off.
- Do not remove the Yellow Cap until you are ready to inject.
- Do not press or touch the Orange Needle Cover with your fingers. The Needle is inside.
- Do not put the Yellow Cap back on the DUPIXENT Pre-filled Pen after you have removed it.

C2. Pinch Skin and Place
Pinch the skin before and during the injection.
- Hold the DUPIXENT Pre-filled Pen as shown so that you can see the Window. Place the Orange Needle Cover on the skin.
- Place the Orange Needle Cover on the skin at approximately a 90-degree angle.
- Pinching is not needed for adults and children aged 12 years and older.
C3. Press down ➜ Watch Window turn fully yellow ➜ Then count to 5
Press and hold the DUPIXENT Pre-filled Pen firmly against the skin until you cannot see the Orange Needle Cover.; - There will be a "click" when the injection starts, and - The Window will start to turn yellow. - Keep pressing the DUPIXENT Pre-filled Pen against the skin. | Keep pressing the DUPIXENT Pre-filled Pen against the skin and watch the window:; - The Window will turn completely yellow, and - You will hear a 2nd "click". - Keep pressing the DUPIXENT Pre-filled Pen against the skin. | Keep pressing the DUPIXENT Pre-filled Pen against the skin and count to 5 to make sure you get your full dose.

Pinching of the skin is not needed for adults and children aged 12 years and older.

C4. Remove

- After you have completed the injection pull straight up to remove DUPIXENT Pre-filled Pen from the skin. The Orange Needle Cover will cover the needle.
- If you see any blood at the site, lightly dab a cotton ball or gauze pad.
- Do not rub the skin after the injection.
- If the Window does not turn completely Yellow, or if it looks like medicine is still coming out of the pen, you may not have received a full dose. Dispose of (throw away) the pen and contact your healthcare provider right away.
- Do not give a second dose without speaking to your healthcare provider.

D. Dispose of used DUPIXENT Pre-filled Pen

How to Dispose of (throw away) DUPIXENT Pre-filled Pen:
Put the used DUPIXENT Pre-filled Pens and Yellow Caps in a FDA-cleared sharps disposal container right away after use.

Do not dispose of (throw away) DUPIXENT Pre-filled Pens and Yellow Caps in your household trash.

If you do not have a FDA-cleared sharps disposal container, you may use a household container that is:

- made of a heavy-duty plastic,
- can be closed with a tightfitting, puncture-resistant lid, without sharps being able to come out,
- upright and stable during use,
- leak-resistant, and
- properly labeled to warn of hazardous waste inside the container.

When your sharps disposal container is almost full, you will need to follow your community guidelines for the right way to dispose of your sharps disposal container. There may be state or local laws about how you should throw away used DUPIXENT Pre-filled Pens.
For more information about safe sharps disposal, and for specific information about sharps disposal in the state that you live in, go to the FDA's website at: http://www.fda.gov/safesharpsdisposal

Do not dispose of your used sharps disposal container in your household trash unless your community guidelines permit this.

Do not recycle your used sharps disposal container.

Keep your sharps disposal container out of the reach of children.

Manufactured by:
Regeneron Pharmaceuticals, Inc.
Tarrytown, NY 10591
U.S. License No. 1760
Marketed by:
sanofi-aventis U.S. LLC (Bridgewater, NJ 08807) and
Regeneron Pharmaceuticals, Inc. (Tarrytown, NY 10591)
DUPIXENT® is a registered trademark of Sanofi Biotechnology
© 2023 Regeneron Pharmaceuticals, Inc. / sanofi-aventis U.S. LLC. All rights reserved.

This Instructions for Use has been approved by the U.S. Food and Drug Administration.

Revised: July 2023

INSTRUCTIONS FOR USE DUPIXENT® (DU-pix-ent) (dupilumab) injection, for subcutaneous use Single-Dose Pre-filled Syringe with Needle Shield

Read this Instructions for Use before using the DUPIXENT Pre-filled Syringe. Do not inject the child until you have been shown how to inject DUPIXENT. Your healthcare provider can show you how to prepare and inject a dose of DUPIXENT before you try to do it yourself the first time. Keep these instructions for future use. Call your healthcare provider if you have any questions.

This device is a Single-Dose Pre-filled Syringe (called "DUPIXENT Syringe" in these instructions). It contains 100 mg of DUPIXENT for injection under the skin (subcutaneous injection).

The parts of the DUPIXENT Syringe are shown below:

Important Information

- Read all of the instructions carefully before using the DUPIXENT Syringe.
- Ask your healthcare provider how often you will need to inject the medicine.
- In children 6 months to less than 12 years of age, DUPIXENT should be given by a caregiver.
- Rotate the injection site each time you inject.
- Do not use the DUPIXENT Syringe if it has been dropped on a hard surface or damaged.
- Do not use the DUPIXENT Syringe if the Needle Cap is missing or not securely attached.
- Do not touch the Plunger Rod until you are ready to inject.
- Do not inject through clothes.
- Do not get rid of any air bubble in the DUPIXENT Syringe.

- To reduce the risk of accidental needle sticks, each pre-filled syringe has a Needle Shield that is automatically activated to cover the needle after you have given the injection.
- Do not pull back on the Plunger Rod at any time.
- Do not remove the Needle Cap until just before you give the injection.
- Throw away (dispose of) the used DUPIXENT Single-Dose Pre-filled Syringe right away after use. See "Step 13: Dispose" below.
- Do not re-use a DUPIXENT Single-Dose Pre-filled Syringe.

How should I store DUPIXENT?

- Keep DUPIXENT Syringes and all medicines out of the reach of children.
- Store DUPIXENT Syringes in the refrigerator between 36°F to 46°F (2°C to 8°C).
- Store DUPIXENT Syringes in the original carton to protect them from light.
- DUPIXENT Syringes can be stored at room temperature up to 77°F (25°C) up to 14 days. Throw away (dispose of) any DUPIXENT Syringes that have been left at room temperature for longer than 14 days.
- Do not shake the DUPIXENT Syringe.
- Do not heat the DUPIXENT Syringe.
- Do not freeze the DUPIXENT Syringe.
- Do not put the DUPIXENT Syringe into direct sunlight.

Step 1: Remove

Remove the DUPIXENT Syringe from the carton by holding the middle of the Syringe Body.

Do not pull off the Needle Cap until you are ready to inject.

Do not use the DUPIXENT Syringe if it has been dropped on a hard surface or damaged.

Step 2: Prepare

Ensure you have the following:

- the DUPIXENT Pre-filled Syringe
- 1 alcohol wipe*
- 1 cotton ball or gauze*
- a sharps disposal container* (See Step 13)

*Items not included in the carton

Step 3: Check

When you receive the DUPIXENT Syringes, always check to see that:

- you have the correct medicine and dose.
- the expiration date on the Single-Dose Pre-filled Syringe has not passed.

Do not use the DUPIXENT Syringe if the expiration date has passed.

Step 4: Inspect

Look at the medicine through the Viewing Window on the DUPIXENT Syringe:

Check to see if the liquid is clear and colorless to pale yellow.

Note: You may see an air bubble, this is normal.

Do not use the DUPIXENT Syringe if the liquid is discolored or cloudy, or if it contains visible flakes or particles.

Step 5: Wait 30 minutes

Lay the DUPIXENT Syringe on a flat surface and let it naturally warm to room temperature for at least 30 minutes.

Do not heat the DUPIXENT Syringe.

Do not put the DUPIXENT Syringe into direct sunlight.

Do not keep DUPIXENT Syringes at room temperature for more than 14 days. Throw away (dispose of) any DUPIXENT Syringes that have been left at room temperature for longer than 14 days.

Step 6: Choose the injection site

- You can inject into the thigh, outer area of the upper arm or stomach, except for the 2 inches (5 cm) around the belly button (navel).
- Choose a different site each time you inject DUPIXENT.

Do not inject into skin that is tender, damaged, bruised or scarred.

Step 7: Clean

Wash your hands.

Clean the injection site with an alcohol wipe.

Let the skin dry before injecting.

Do not touch the injection site again or blow on it before the injection.

Step 8: Remove Needle Cap

Hold the DUPIXENT Syringe in the middle of the Syringe Body with the Needle pointing away from you and pull off the Needle Cap.

Do not put the Needle Cap back on.

Do not touch the Needle.

Inject the medicine right away after removing the Needle Cap.

Step 9: Pinch

Pinch a fold of skin at the injection site (thigh or stomach, except 2 inches around the belly button, or outer area of the upper arm). The figure below shows an example of pinching a fold of skin on the stomach.

Step 10: Insert

Insert the Needle completely into the fold of the skin at about a 45° angle.

Step 11: Push

Relax the pinch.

Push the Plunger Rod down slowly and steadily as far as it will go until the DUPIXENT Syringe is empty.

Note: You will feel some resistance. This is normal.

Step 12: Release and Remove

Lift your thumb to release the Plunger Rod until the Needle is covered by the Needle Shield and then remove the Syringe from the injection site.

Lightly press a cotton ball or gauze on the injection site if you see any blood.

Do not put the Needle Cap back on.

Do not rub the skin after the injection.

Step 13: Dispose

Put used Needles, DUPIXENT Syringes, and Needle Caps in a FDA-cleared sharps disposal container right away after use.

Do not dispose of (throw away) Needles, DUPIXENT Syringes, and Needle Caps in your household trash.

If you do not have a FDA-cleared sharps disposal container, you may use a household container that is:

- made of a heavy-duty plastic,
- can be closed with a tight-fitting, puncture-resistant lid, without sharps being able to come out,
- upright and stable during use,
- leak-resistant, and
- properly labeled to warn of hazardous waste inside the container

When your sharps disposal container is almost full, you will need to follow your community guidelines for the right way to dispose of your sharps disposal container. There may be state or local laws about how you should throw away used Needles and Syringes.

For more information about safe sharps disposal, and for specific information about sharps disposal in the state that you live in, go to the FDA's website at: http://www.fda.gov/safesharpsdisposal

Do not dispose of your used sharps disposal container in your household trash unless your community guidelines permit this. Do not recycle your used sharps disposal container.

Do not put the Needle Cap back on.

Manufactured by: Regeneron Pharmaceuticals, Inc. Tarrytown, NY 10591
U.S. License No. 1760

Marketed by: sanofi-aventis U.S. LLC (Bridgewater, NJ 08807) and Regeneron Pharmaceuticals,
Inc. (Tarrytown, NY 10591)
DUPIXENT® is a registered trademark of Sanofi Biotechnology

© 2023 Regeneron Pharmaceuticals, Inc. / sanofi-aventis U.S. LLC. All rights reserved.

This Instructions for Use has been approved by the U.S. Food and Drug Administration.

Revised: July 2023

PRINCIPAL DISPLAY PANEL - 300 mg/2 mL Syringe Carton

NDC 0024-5914-01

Rx Only

DUPIXENT®
(dupilumab)
Injection

300 mg/2 mL (150 mg/mL)

For Subcutaneous Use Only.

300 mg/2 mL
Per Pre-filled Syringe

2
Single-dose
Pre-filled Syringes
with Needle Shield

Keep out of reach of children. Do not use after
expiration. Do not use if seal is broken or damaged.

Store refrigerated at 36° to 46°F (2° to 8°C) in the original carton.
Dosage and Administration: See package insert for dosage information and directions for use.

sanofi | REGENERON

PRINCIPAL DISPLAY PANEL - 200 mg/1.14 mL Syringe Carton

NDC 0024-5918-01

Rx Only

DUPIXENT®
(dupilumab)
Injection

200 mg/1.14 mL (175 mg/mL)

For Subcutaneous Use Only.

200 mg/1.14 mL
Per Pre-filled Syringe

2
Single-dose
Pre-filled Syringes
with Needle Shield

Keep out of reach of children. Do not use after
expiration. Do not use if seal is broken or damaged.

Store refrigerated at 36° to 46°F (2° to 8°C) in the original carton.
Dosage and Administration: See package insert for dosage information and directions for use.

sanofi | REGENERON

PRINCIPAL DISPLAY PANEL - 300 mg/2 mL Pen Carton

NDC 0024-5915-02
Rx Only

DUPIXENT®
(dupilumab)
Injection
Single-dose Pre-filled Pen

300 mg/2 mL (150 mg/mL)

For Subcutaneous Use Only.

2
Single-dose
Pre-filled Pens

Keep out of reach of children. Do not use
after expiration. Do not use if seal is broken
or damaged.

Store refrigerated at 36° to 46°F (2° to 8°C) in the original carton.
Do NOT freeze. Do NOT heat.
Dosage and Administration: See package insert for dosage information
and directions for use.

300 mg/2 mL
Per Pre-filled Pen

sanofi | REGENERON

PRINCIPAL DISPLAY PANEL - 200 mg/1.14 mL Pen Carton

NDC 0024-5919-02
Rx Only

DUPIXENT®
(dupilumab)
Injection
Single-dose Pre-filled Pen

200 mg/1.14 mL (175 mg/mL)

For Subcutaneous Use Only.

2
Single-dose
Pre-filled Pens

Keep out of reach of children. Do not use after
expiration. Do not use if seal is broken or damaged.

Store refrigerated at 36° to 46°F (2° to 8°C) in
the original carton. Do not freeze. Do not heat.
Dosage and Administration: See package insert
for dosage information and directions for use.

200 mg/1.14 mL
Per Pre-filled Pen

sanofi | REGENERON

PRINCIPAL DISPLAY PANEL - 100 mg/0.67 mL Syringe Carton

NDC 0024-5911-02

Rx Only

DUPIXENT®
(dupilumab)
Injection

100 mg/0.67 mL (150 mg/mL)

For Subcutaneous Use Only.

2
Single-dose
Pre-filled Syringes
with Needle Shield

Keep out of reach of children. Do not use after
expiration. Do not use if seal is broken or damaged.

Store refrigerated at 36° to 46°F (2° to 8°C) in the original carton.
Dosage and Administration: See package insert for dosage information and directions for use.

100 mg/0.67 mL

sanofi | REGENERON